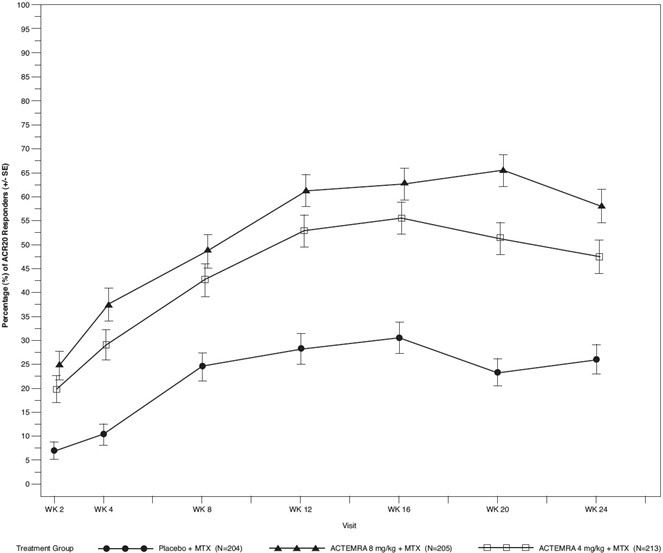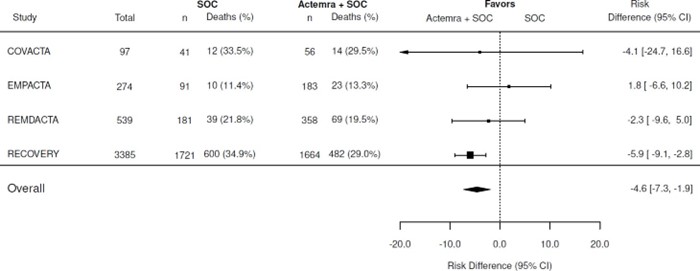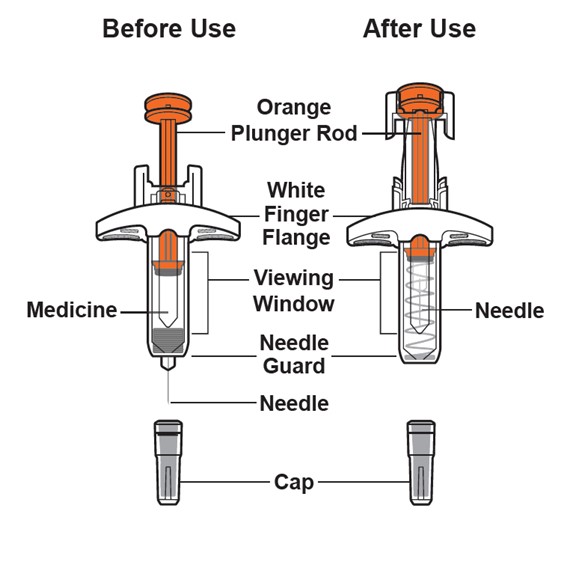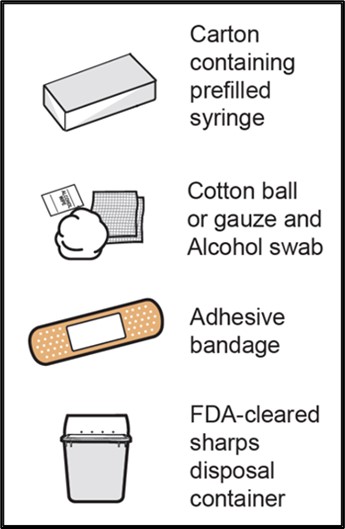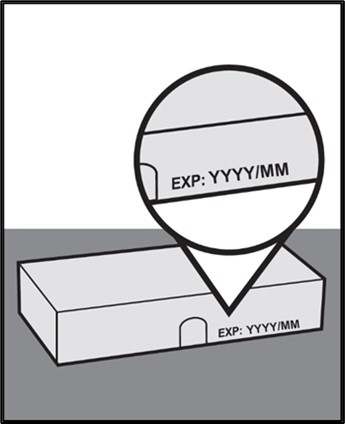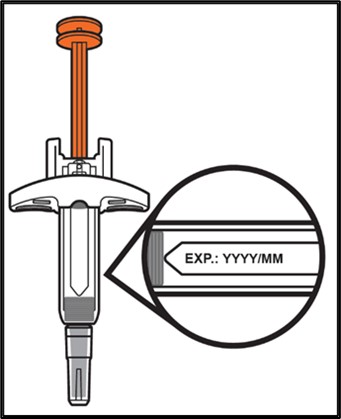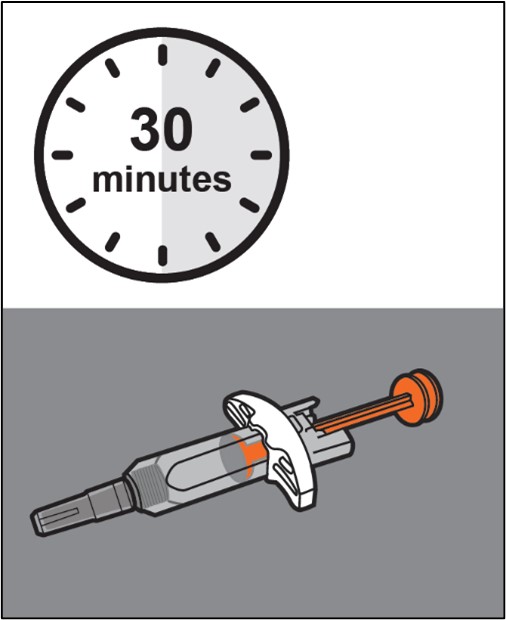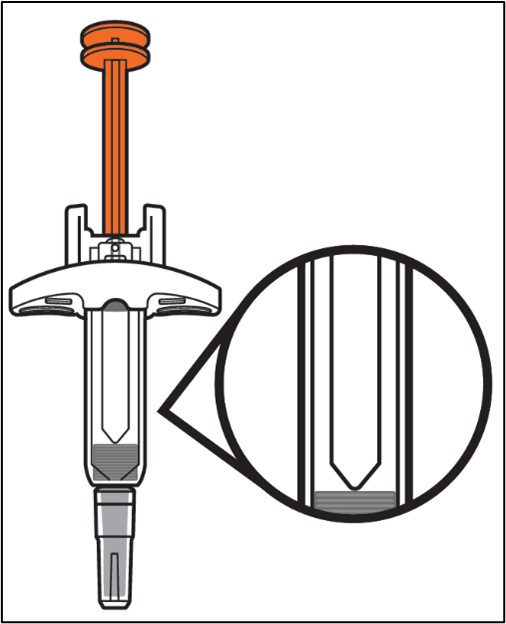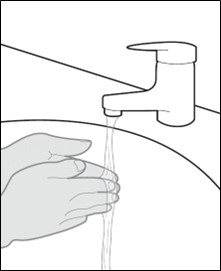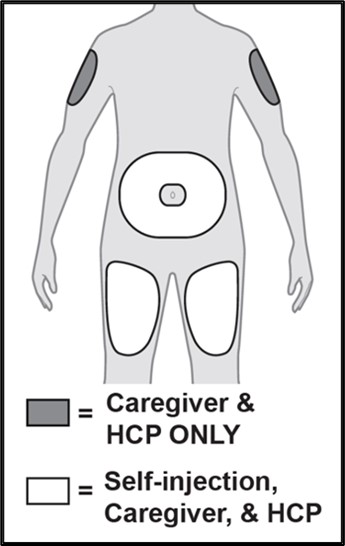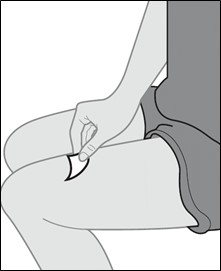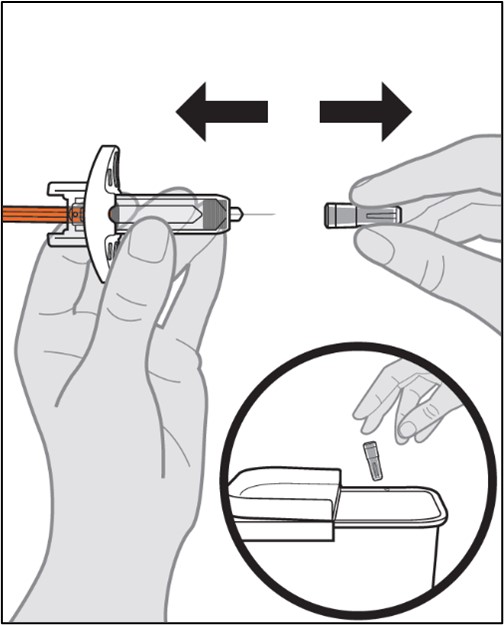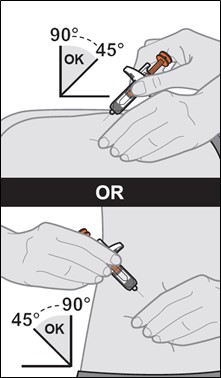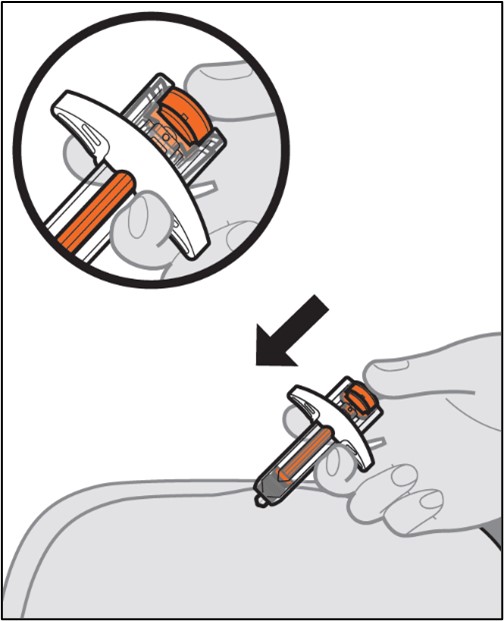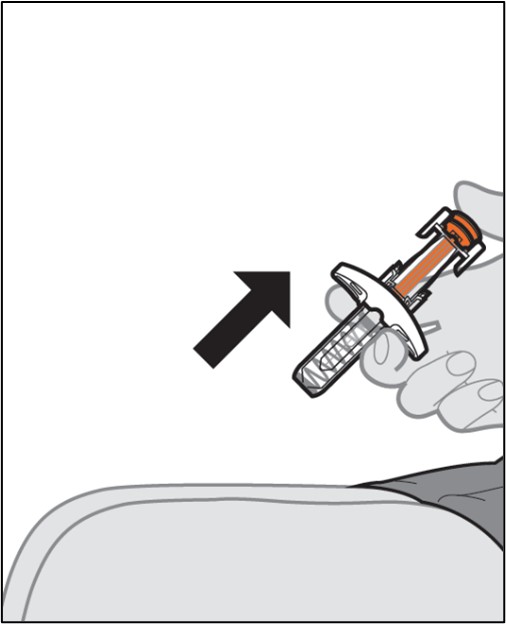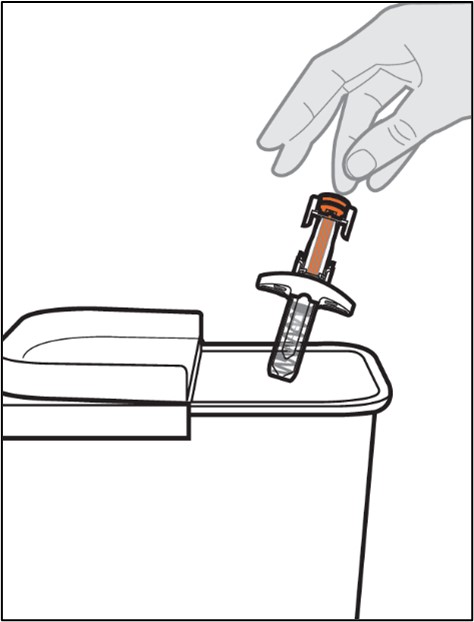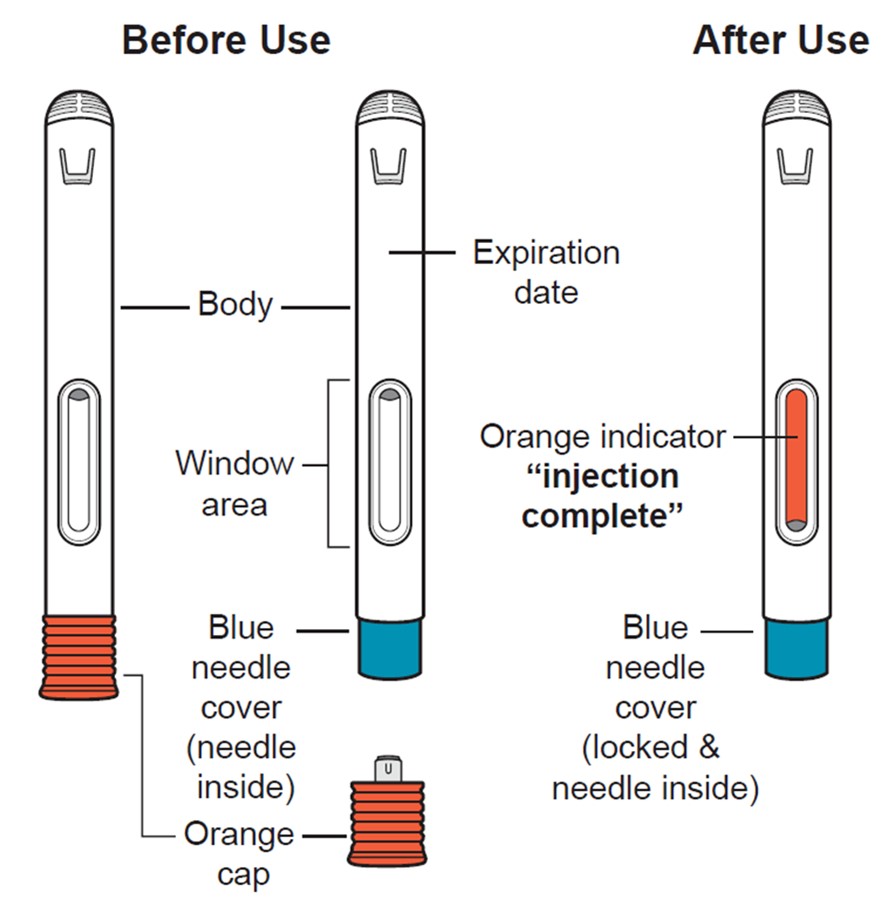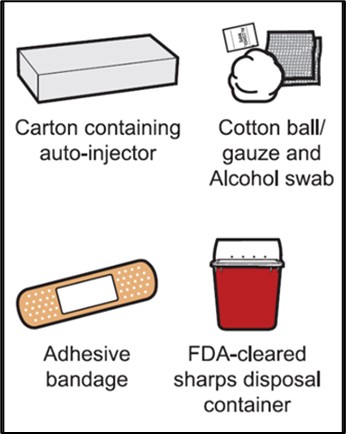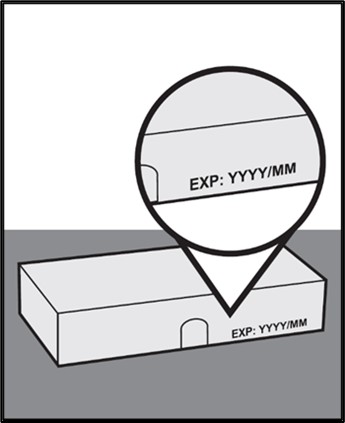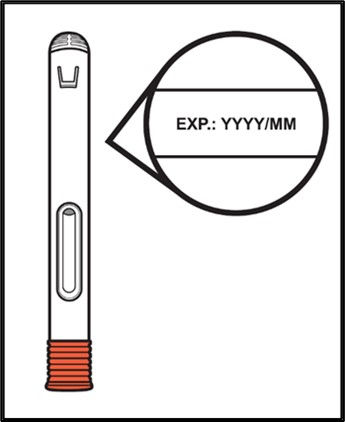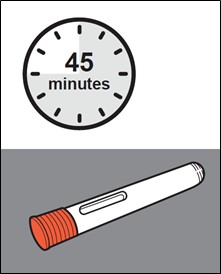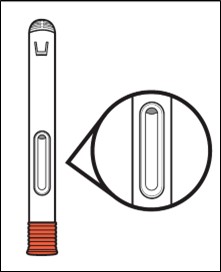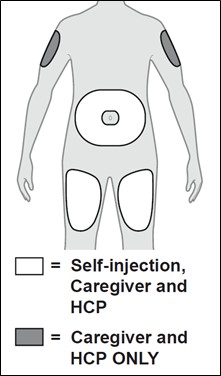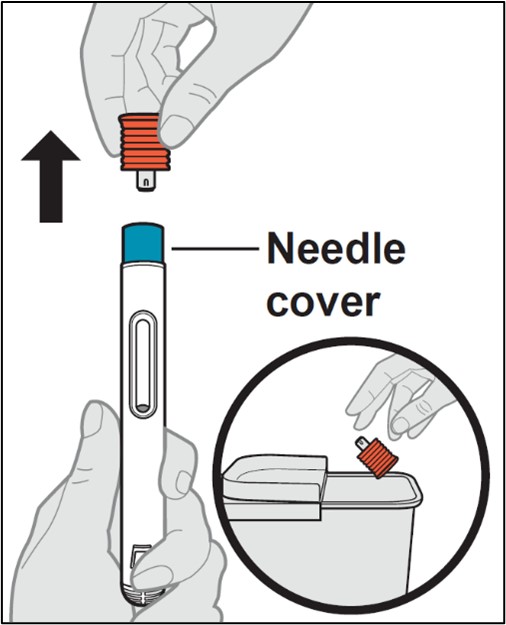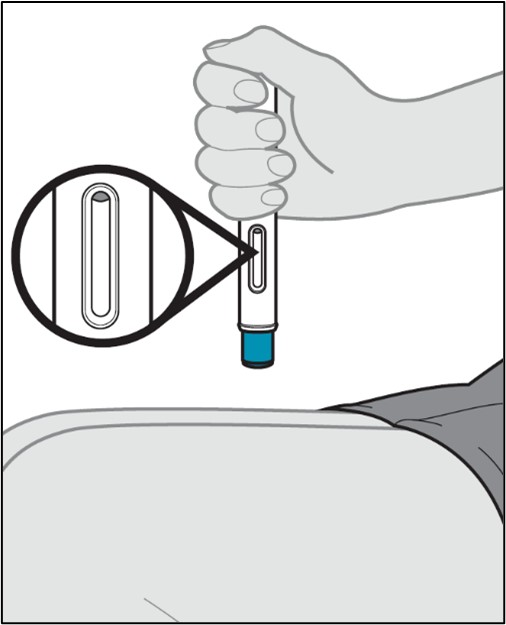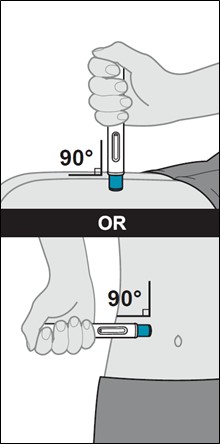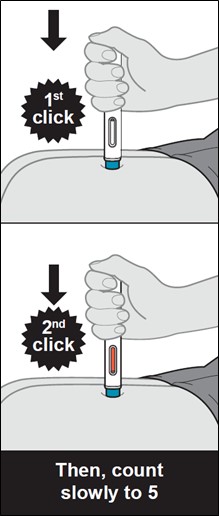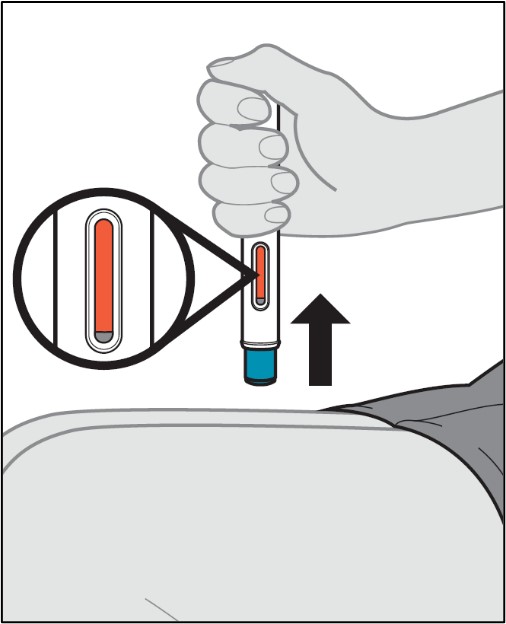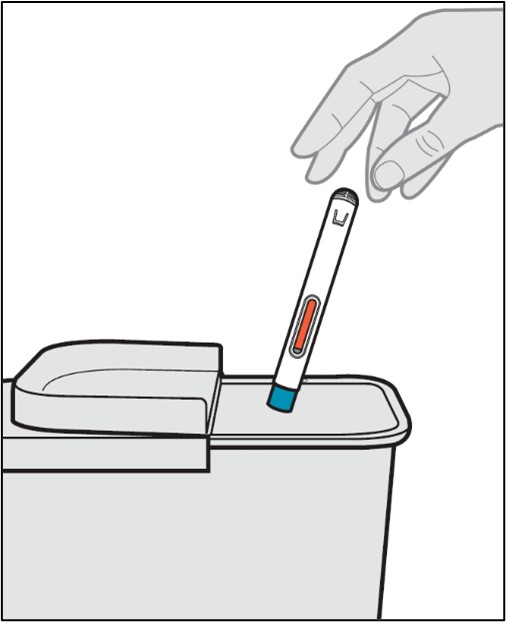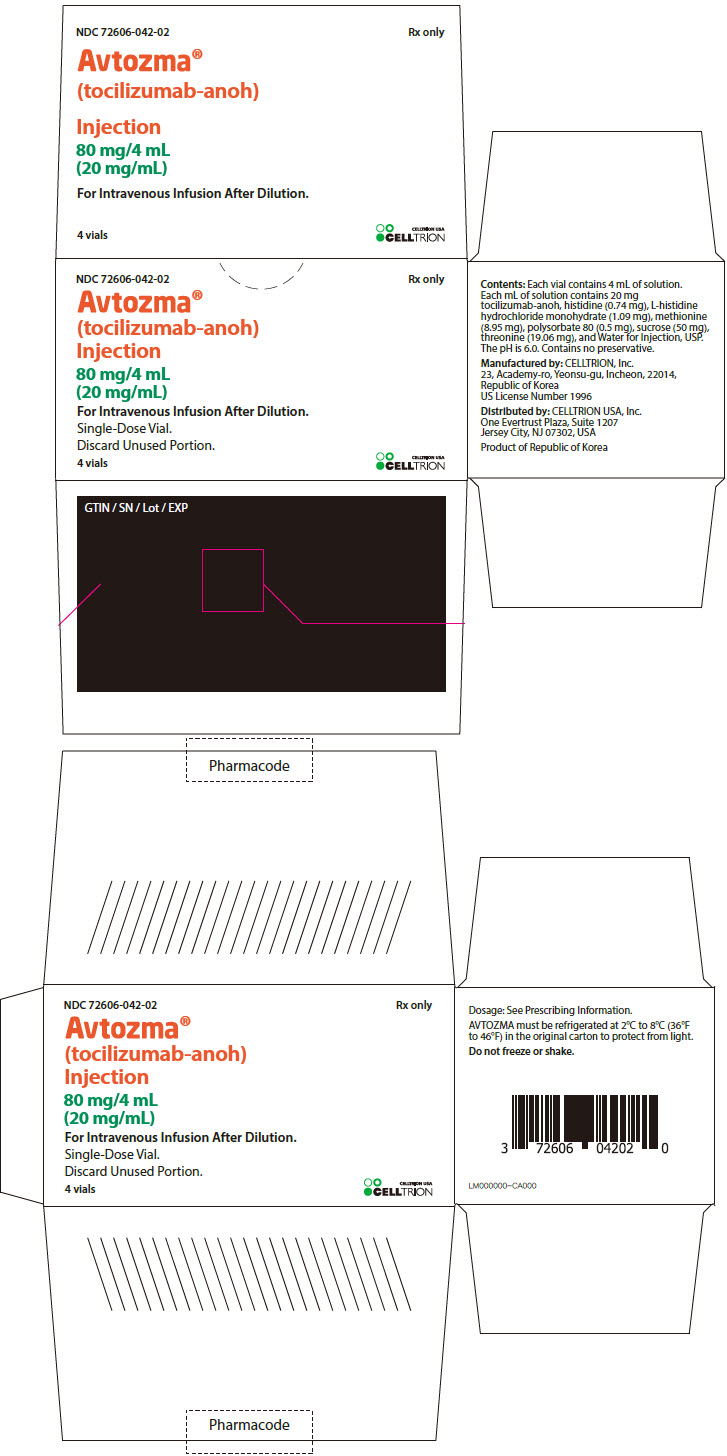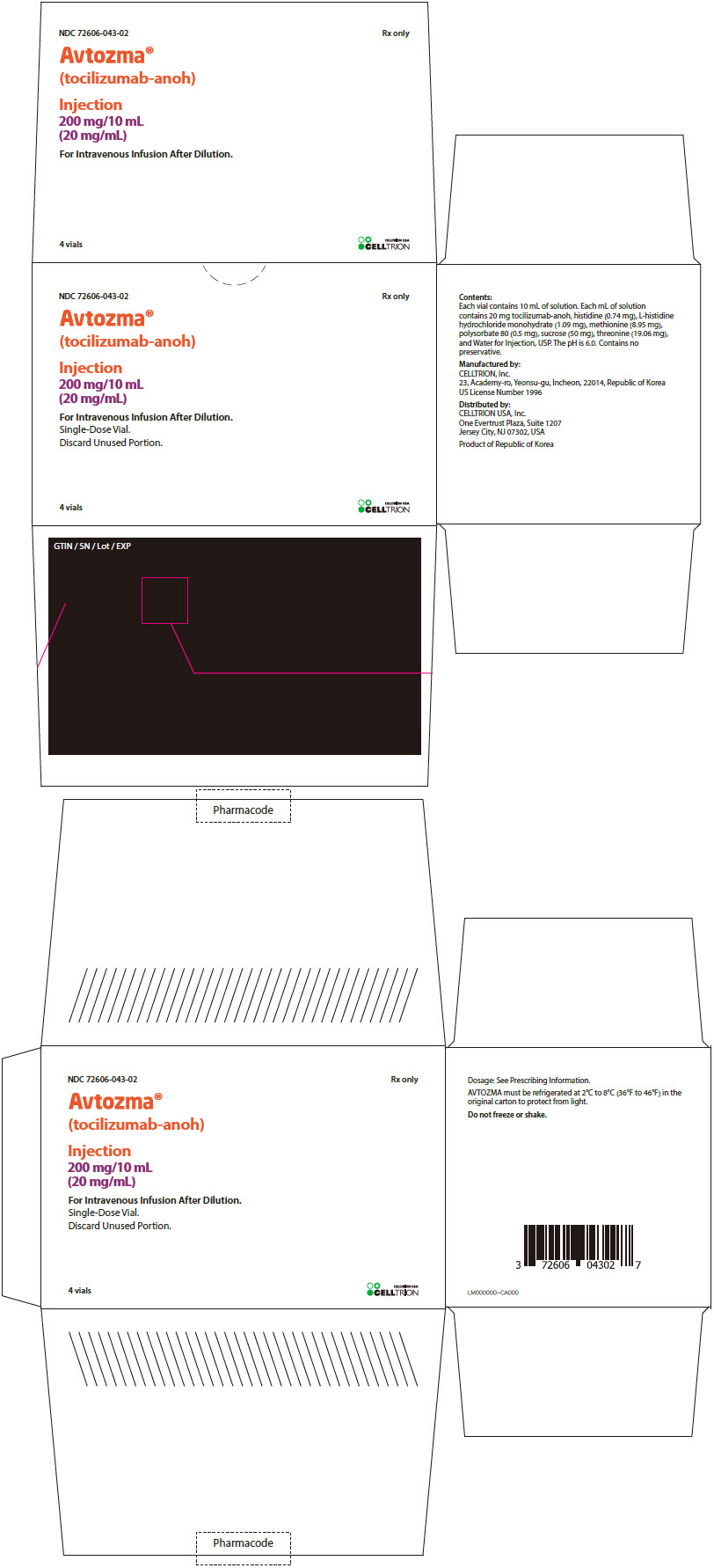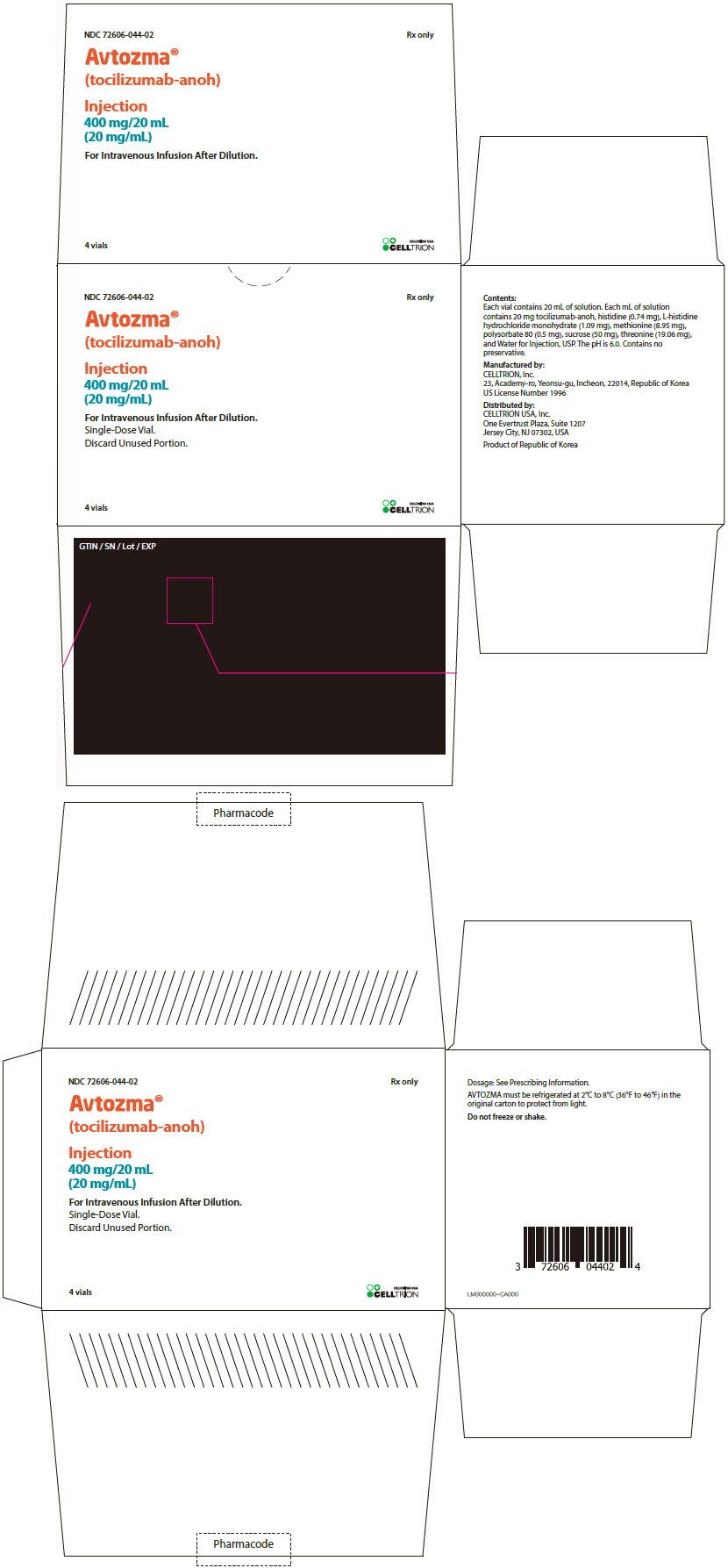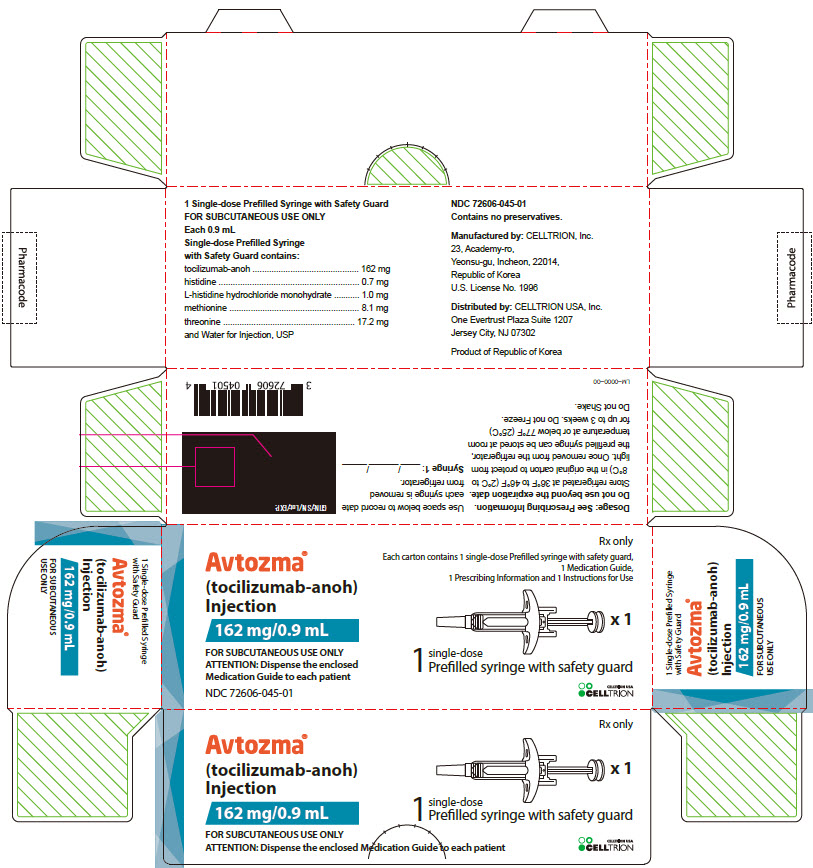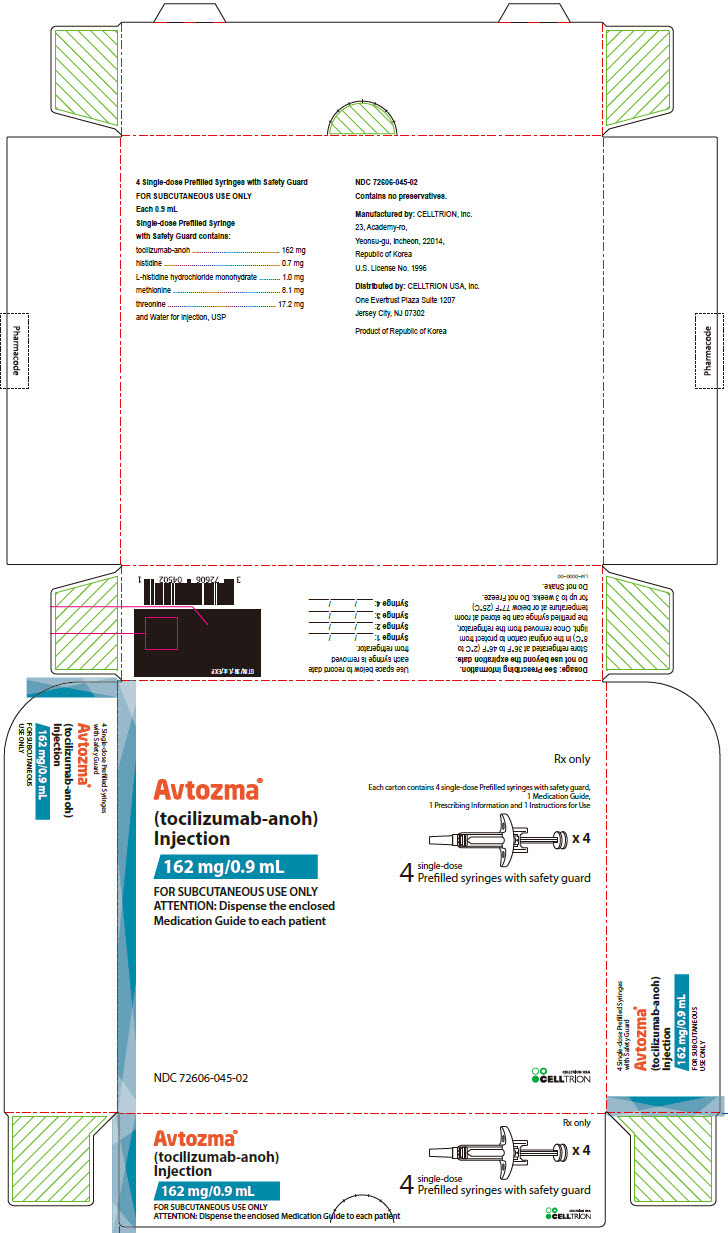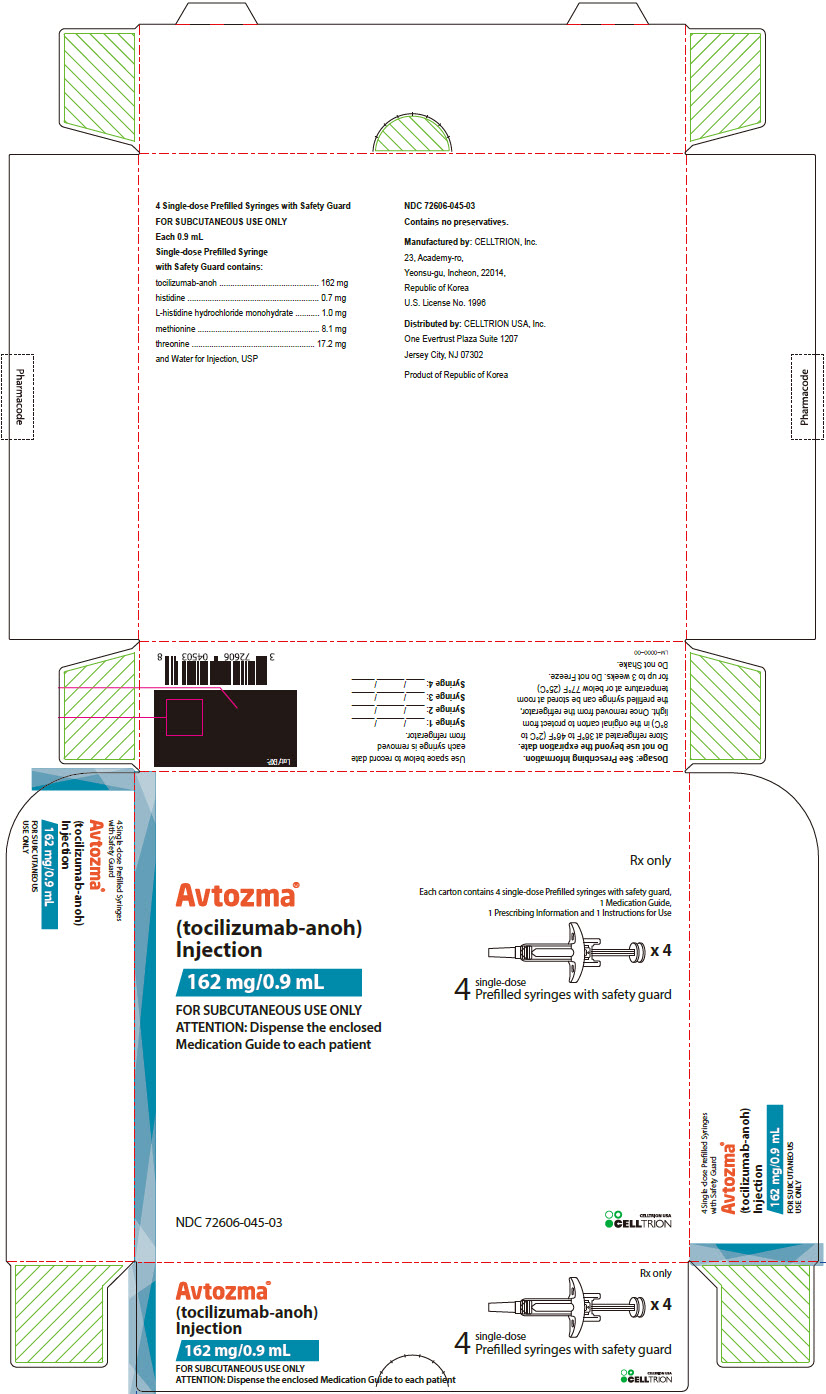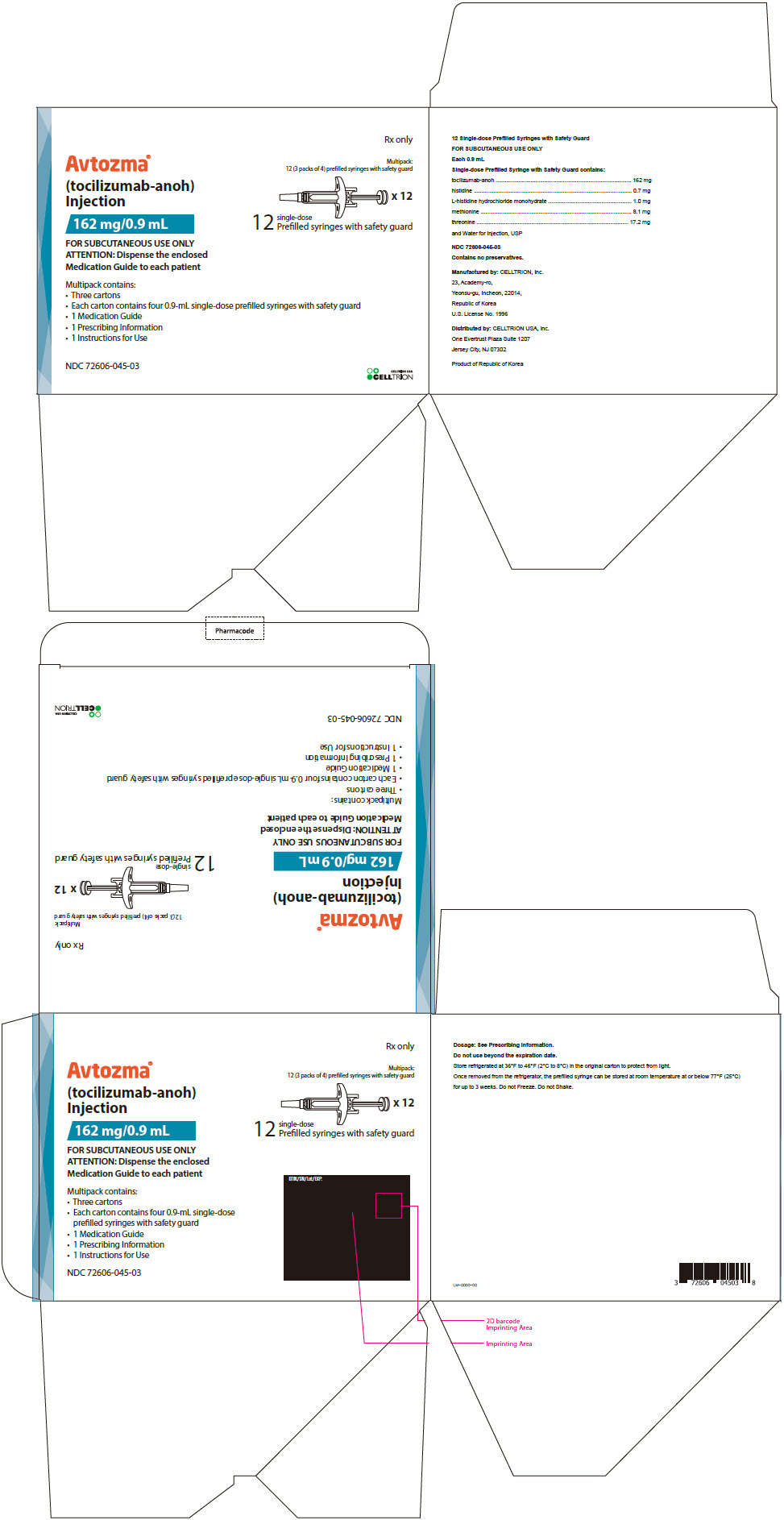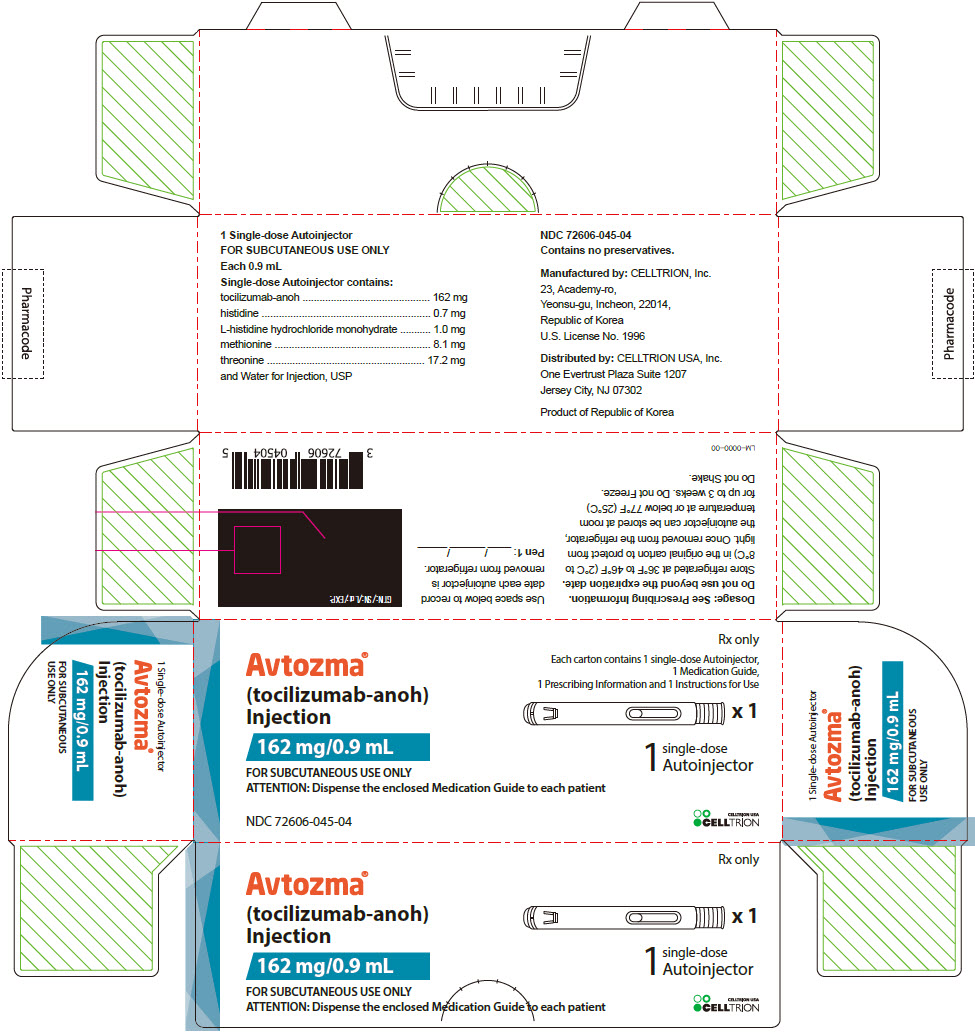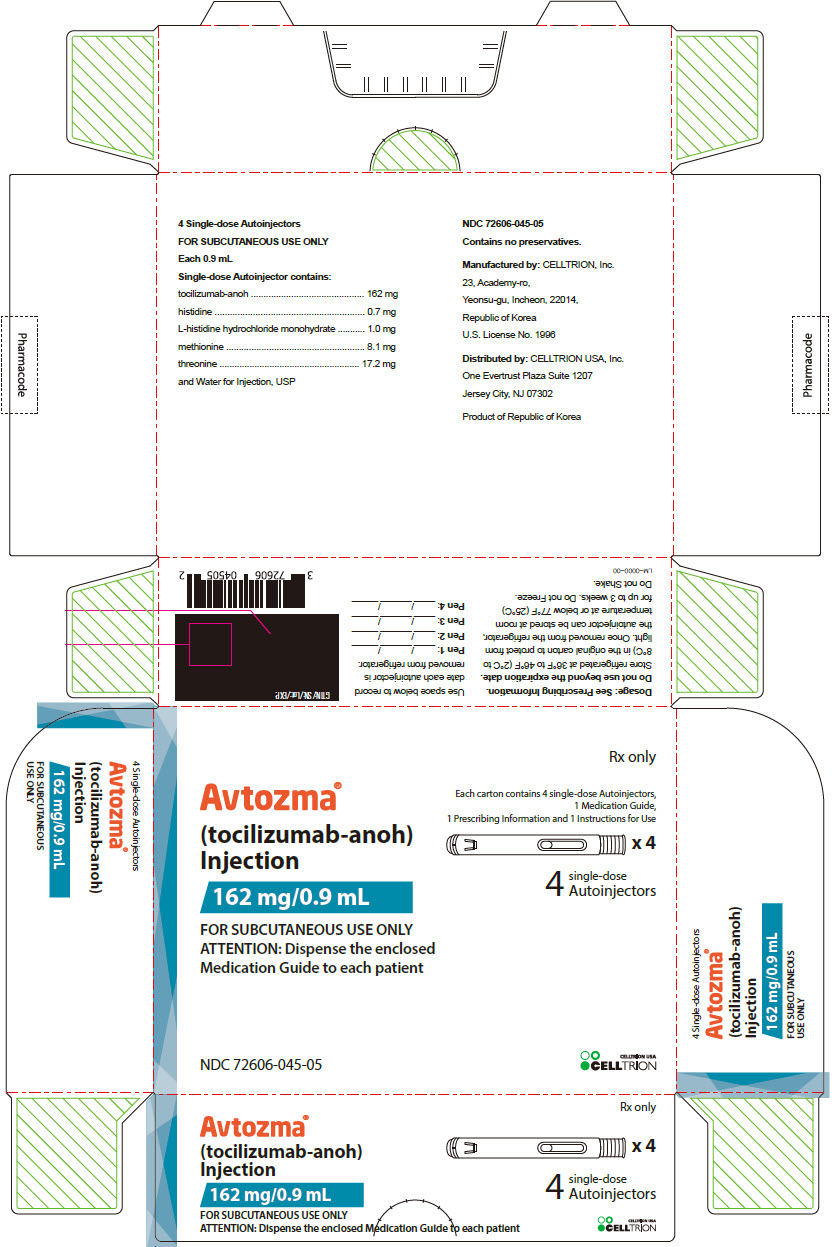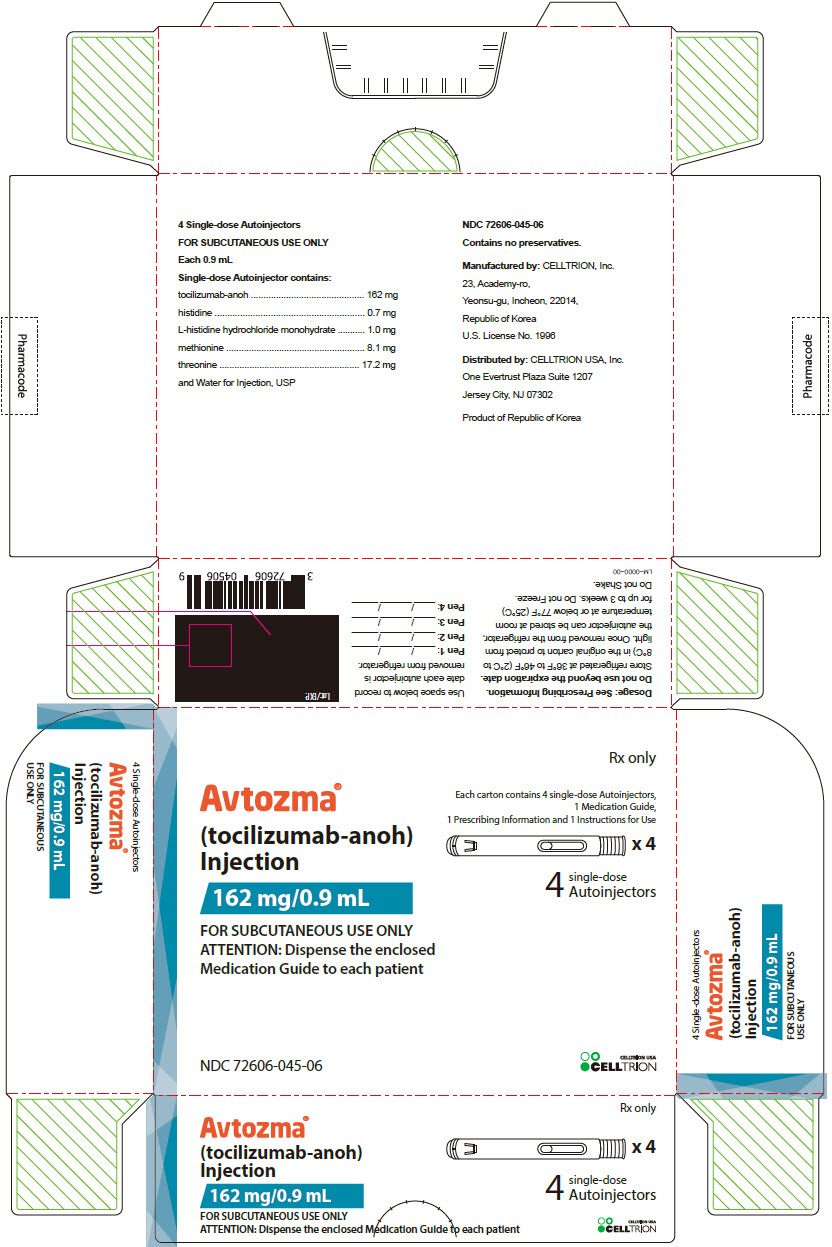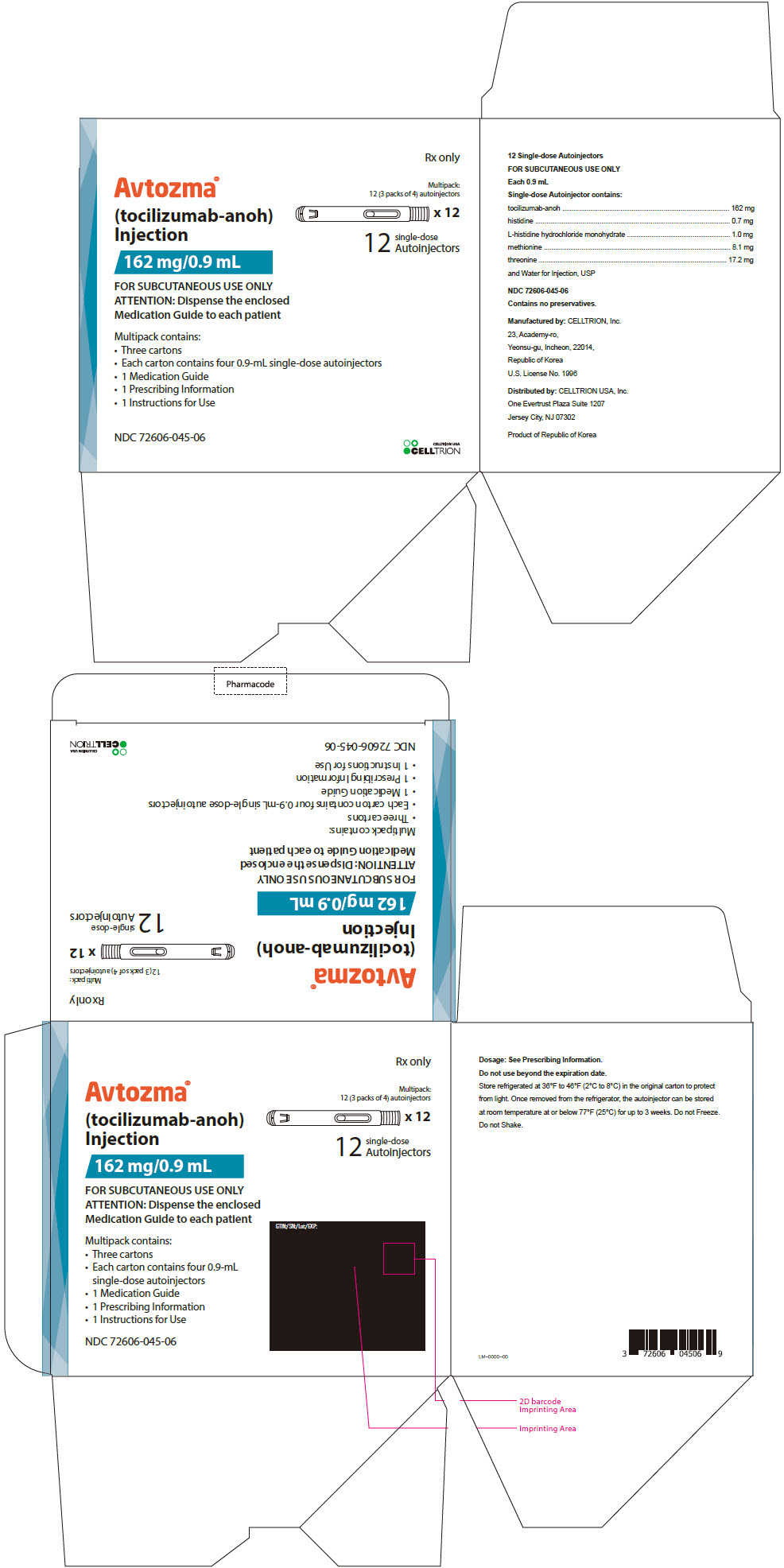 DRUG LABEL: AVTOZMA
NDC: 72606-042 | Form: INJECTION, SOLUTION
Manufacturer: CELLTRION USA, Inc.
Category: prescription | Type: HUMAN PRESCRIPTION DRUG LABEL
Date: 20260123

ACTIVE INGREDIENTS: tocilizumab 80 mg/4 mL

HIGHLIGHTS OF PRESCRIBING INFORMATION

These highlights do not include all the information needed to use AVTOZMA safely and effectively. See full prescribing information for AVTOZMA.
AVTOZMA® (tocilizumab-anoh) injection, for intravenous or subcutaneous use
Initial U.S. Approval: 2025
AVTOZMA (tocilizumab-anoh) is biosimilar [Biosimilar means that the biological product is approved based on data demonstrating that it is highly similar to an FDA-approved biological product, known as a reference product, and that there are no clinically meaningful differences between the biosimilar product and the reference product. Biosimilarity of AVTOZMA has been demonstrated for the condition(s) of use (e.g. indication(s), dosing regimen(s)), strength(s), dosage form(s), and route(s) of administration described in its Full Prescribing Information.] to ACTEMRA (tocilizumab).

WARNING: RISK OF SERIOUS INFECTIONS

See full prescribing information for complete boxed warning.

- Serious infections leading to hospitalization or death including tuberculosis (TB), bacterial, invasive fungal, viral, and other opportunistic infections have occurred in patients receiving tocilizumab products. (5.1)
- If a serious infection develops, interrupt AVTOZMA until the infection is controlled. (5.1)
- Perform test for latent TB (except patients with COVID-19); if positive, start treatment for TB prior to starting AVTOZMA. (5.1)
- Monitor all patients for active TB during treatment, even if initial latent TB test is negative. (5.1)

RECENT MAJOR CHANGES

Indications and Usage (1.5) 07/2025
Dosage and Administration (2.1, 2.6) 07/2025

1 INDICATIONS AND USAGE

AVTOZMA® (tocilizumab-anoh) is an interleukin-6 (IL-6) receptor antagonist indicated for treatment of:

Rheumatoid Arthritis (RA) (1.1)

- Adult patients with moderately to severely active rheumatoid arthritis who have had an inadequate response to one or more Disease-Modifying Anti-Rheumatic Drugs (DMARDs).

Giant Cell Arteritis (GCA) (1.2)

- Adult patients with giant cell arteritis.

Polyarticular Juvenile Idiopathic Arthritis (PJIA) (1.3)

- Patients 2 years of age and older with active polyarticular juvenile idiopathic arthritis.

Systemic Juvenile Idiopathic Arthritis (SJIA) (1.4)

- Patients 2 years of age and older with active systemic juvenile idiopathic arthritis.

Cytokine Release Syndrome (CRS) (1.5)

- Adults and pediatric patients with 2 years of age and older with chimeric antigen recept (CAR) T cell-induced severe or life-threatening cytokine release syndrome.

Coronavirus Disease 2019 (COVID-19) (1.6)

- Hospitalized adult patients with coronavirus disease 2019 (COVID-19) who are receiving systemic corticosteroids and require supplemental oxygen, non-invasive or invasive mechanical ventilation, or extracorporeal membrane oxygenation (ECMO).

2 DOSAGE AND ADMINISTRATION

For RA, pJIA and sJIA, AVTOZMA may be used alone or in combination with methotrexate: and in RA, other non-biologic DMARDs may be used. (2)

General Administration and Dosing Information (2.1)

- RA, GCA, PJIA and SJIA It is recommended that AVTOZMA not be initiated in patients with an absolute neutrophil count (ANC) below 2000 per mm^3, platelet count below 100,000 per mm^3, or ALT or AST above 1.5 times the upper limit of normal (ULN)(5.3, 5.4).
- COVID-19 It is recommended that AVTOZMA not be initiated in patients with an absolute neutrophil count (ANC) below 1000 per mm^3, platelet count below 50,000 mm^3, or ALT or AST above 10 times ULN (5.3, 5.4).
- In RA, CRS, or COVID-19 patients, AVTOZMA doses exceeding 800 mg per infusion are not recommended. (2.2, 2.6, 12.3)
- In GCA patients, AVTOZMA doses exceeding 600 mg per infusion are not recommended. (2.3, 12.3)

Rheumatoid Arthritis (2.2)

Recommended Adult Intravenous Dosage:

When used in combination with non-biologic DMARDs or as monotherapy the recommended starting dose is 4 mg per kg every 4 weeks followed by an increase to 8 mg per kg every 4 weeks based on clinical response.

Recommended Adult Subcutaneous Dosage:

Patients less than 100 kg weight | 162 mg administered subcutaneously every other week, followed by an increase to every week based on clinical response
Patients at or above 100 kg weight | 162 mg administered subcutaneously every week

Giant Cell Arteritis (2.3)

Recommended Adult Intravenous Dosage:

The recommended dose is 6 mg per kg every 4 weeks in combination with a tapering course of glucocorticoids. AVTOZMA can be used alone following discontinuation of glucocorticoids.

Recommended Adult Subcutaneous Dosage:

The recommended dose is 162 mg given once every week as a subcutaneous injection, in combination with a tapering course of glucocorticoids.

A dose of 162 mg given once every other week as a subcutaneous injection, in combination with a tapering course of glucocorticoids, may be prescribed based on clinical considerations.

AVTOZMA can be used alone following discontinuation of glucocorticoids.

Polyarticular Juvenile Idiopathic Arthritis (2.4)

Recommended Intravenous PJIA Dosage Every 4 Weeks
Patients less than 30 kg weight | 10 mg per kg
Patients at or above 30 kg weight | 8 mg per kg

Recommended Subcutaneous PJIA Dosage
Patients less than 30 kg weight | 162 mg once every three weeks
Patients at or above 30 kg weight | 162 mg once every two weeks

Systemic Juvenile Idiopathic Arthritis (2.5)

Recommended Intravenous SJIA Dosage Every 2 Weeks
Patients less than 30 kg weight | 12 mg per kg
Patients at or above 30 kg weight | 8 mg per kg

Recommended Subcutaneous SJIA Dosage
Patients less than 30 kg weight | 162 mg every two weeks
Patients at or above 30 kg weight | 162 mg every week

Cytokine Release Syndrome (2.6)

Recommened Intravenous CRS Dosage
Patients less than 30 kg weight | 12 mg per kg
Patients at or above 30 kg weight | 8 mg per kg
Alone or in combination with corticosteroids

Coronavirus Disease 2019 (2.7)

The recommended dosage of AVTOZMA for adult patients with COVID-19 is 8 mg per kg administered by a 60-minute intravenous infusion.

Administration of Intravenous Formulation (2.8)

- For patients with RA, GCA, COVID-19, CRS, PJIA, and SJIA patients at or above 30 kg, dilute to 100 mL in 0.9% or 0.45% Sodium Chloride Injection, USP for intravenous infusion using aseptic technique.
- For PJIA, CRS and SJIA patients less than 30 kg, dilute to 50 mL in 0.9% or 0.45% Sodium Chloride Injection, USP for intravenous infusion using aseptic technique.
- Administer as a single intravenous drip infusion over 1 hour; do not administer as bolus or push.

Administration of Subcutaneous Formulation (2.9)

- Follow the Instructions for Use for prefilled syringe and prefilled autoinjector

Dose Modifications (2.10)

- Recommended for management of certain dose-related laboratory changes including elevated liver enzymes, neutropenia, and thrombocytopenia.

3 DOSAGE FORMS AND STRENGTHS

Intravenous Infusion

Injection: 80 mg/4 mL (20 mg/mL), 200 mg/10 mL (20 mg/mL),

400 mg/20 mL (20 mg/mL) in single-dose vials for further dilution prior to intravenous infusion (3)

Subcutaneous Injection

Injection: 162 mg/0.9 mL in a single-dose prefilled syringe or single-dose prefilled autoinjector (3)

4 CONTRAINDICATIONS

- Known hypersensitivity to tocilizumab products. (4)

5 WARNINGS AND PRECAUTIONS

- Serious Infections – do not administer AVTOZMA during an active infection, including localized infections. If a serious infection develops, interrupt AVTOZMA until the infection is controlled. (5.1)
- Gastrointestinal (GI) perforation—use with caution in patients who may be at increased risk. (5.2)
- Hepatotoxicity- Monitor patients for signs and symptoms of hepatic injury. Modify or discontinue AVTOZMA if abnormal liver tests persist or worsen or if clinical signs and symptoms of liver disease develop. (2.8, 5.3)
- Laboratory monitoring—recommended due to potential consequences of treatment-related changes in neutrophils, platelets, lipids, and liver function tests. (2.8, 5.4)
- Hypersensitivity reactions, including anaphylaxis and death and serious cutaneous reactions including Drug Reaction with Eosinophilia and Systemic Symptoms (DRESS) – discontinue AVTOZMA, treat promptly, and monitor until reaction resolves. (5.6)
- Live vaccines—Avoid use with AVTOZMA. (5.9, 7.3)

6 ADVERSE REACTIONS

Most common adverse reactions (incidence of at least 5%): upper respiratory tract infections, nasopharyngitis, headache, hypertension, increased ALT, injection site reactions. (6)

To report SUSPECTED ADVERSE REACTIONS, contact CELLTRION USA Inc., at 1-800-560-9414 or FDA at 1-800-FDA-1088 or www.fda.gov/medwatch

8 USE IN SPECIFIC POPULATIONS

- Pregnancy: Based on animal data, may cause fetal harm. (8.1)
- Lactation: Discontinue drug or nursing taking into consideration importance of drug to mother. (8.2)

FULL PRESCRIBING INFORMATION

WARNING: RISK OF SERIOUS INFECTIONS

Patients treated with tocilizumab products including AVTOZMA are at increased risk for developing serious infections that may lead to hospitalization or death [see Warnings and Precautions (5.1), Adverse Reactions (6.1)]. Most patients who developed these infections were taking concomitant immunosuppressants such as methotrexate or corticosteroids.

If a serious infection develops, interrupt AVTOZMA until the infection is controlled. Reported infections include:

- Active tuberculosis, which may present with pulmonary or extrapulmonary disease. Patients, except those with COVID-19, should be tested for latent tuberculosis before AVTOZMA use and during therapy. Treatment for latent infection should be initiated prior to AVTOZMA use.
- Invasive fungal infections, including candidiasis, aspergillosis, and pneumocystis. Patients with invasive fungal infections may present with disseminated, rather than localized, disease.
- Bacterial, viral and other infections due to opportunistic pathogens.

The risks and benefits of treatment with AVTOZMA should be carefully considered prior to initiating therapy in patients with chronic or recurrent infection.

Patients should be closely monitored for the development of signs and symptoms of infection during and after treatment with AVTOZMA, including the possible development of tuberculosis in patients who tested negative for latent tuberculosis infection prior to initiating therapy [see Warnings and Precautions (5.1)].

1 INDICATIONS AND USAGE

1.1 Rheumatoid Arthritis (RA)

AVTOZMA® (tocilizumab-anoh) is indicated for the treatment of adult patients with moderately to severely active rheumatoid arthritis who have had an inadequate response to one or more Disease-Modifying Anti-Rheumatic Drugs (DMARDs).

1.2 Giant Cell Arteritis (GCA)

AVTOZMA® (tocilizumab-anoh) is indicated for the treatment of giant cell arteritis (GCA) in adult patients.

1.3 Polyarticular Juvenile Idiopathic Arthritis (PJIA)

AVTOZMA® (tocilizumab-anoh) is indicated for the treatment of active polyarticular juvenile idiopathic arthritis in patients 2 years of age and older.

1.4 Systemic Juvenile Idiopathic Arthritis (SJIA)

AVTOZMA® (tocilizumab-anoh) is indicated for the treatment of active systemic juvenile idiopathic arthritis in patients 2 years of age and older.

1.5 Cytokine Release Syndrome (CRS)

AVTOZMA® (tocilizumab-anoh) is indicated for the treatment of chimeric antigen receptor (CAR) T cell-induced severe or life-threatening cytokine release syndrome in adults and pediatric patients 2 years of age and older.

1.6 Coronavirus Disease 2019 (COVID-19)

AVTOZMA® (tocilizumab-anoh) is indicated for the treatment of coronavirus disease 2019 (COVID-19) in hospitalized adult patients who are receiving systemic corticosteroids and require supplemental oxygen, non- invasive or invasive mechanical ventilation, or extracorporeal membrane oxygenation (ECMO).

2 DOSAGE AND ADMINISTRATION

2.1 General Considerations for Administration

Not Recommended for Concomitant Use with Biological DMARDs

Tocilizumab products have not been studied in combination with biological DMARDs such as TNF antagonists, IL-1R antagonists, anti-CD20 monoclonal antibodies and selective co-stimulation modulators because of the possibility of increased immunosuppression and increased risk of infection. Avoid using AVTOZMA with biological DMARDs.

Baseline Laboratory Evaluation Prior to Treatment

Obtain and assess baseline complete blood count (CBC) and liver function tests prior to treatment.

- RA, GCA, PJIA and SJIA – It is recommended that AVTOZMA not be initiated in patients with an absolute neutrophil count (ANC) below 2000 per mm^3, platelet count below 100,000 per mm^3, or ALT or AST above 1.5 times the upper limit of normal (ULN) [see Warnings and Precautions (5.3, 5.4)].
- CRS - Patients with severe or life-threatening CRS frequently have cytopenias or elevated ALT or AST due to the lymphodepleting chemotherapy or the CRS. The decision to administer AVTOZMA should take in to account the potential benefit of treating the CRS versus the risks of short-term treatment with AVTOZMA.
- COVID-19 – It is recommended that AVTOZMA not be initiated in patients with an absolute neutrophil count (ANC) below 1000 per mm^3, platelet count below 50,000 mm^3, or ALT or AST above 10 times ULN [see Warnings and Precautions (5.3, 5.4)].

2.2 Recommended Dosage for Rheumatoid Arthritis

AVTOZMA may be used as monotherapy or concomitantly with methotrexate or other non-biologic DMARDs as an intravenous infusion or as a subcutaneous injection.

Recommended Intravenous Dosage Regimen:

The recommended dosage of AVTOZMA for adult patients given as a 60-minute single intravenous drip infusion is 4 mg per kg every 4 weeks followed by an increase to 8 mg per kg every 4 weeks based on clinical response.

- Reduction of dose from 8 mg per kg to 4 mg per kg is recommended for management of certain dose-related laboratory changes including elevated liver enzymes, neutropenia, and thrombocytopenia [see Dosage and Administration (2.10), Warnings and Precautions (5.3, 5.4), and Adverse Reactions (6.1)].
- Doses exceeding 800 mg per infusion are not recommended in RA patients [see Clinical Pharmacology (12.3)].

Recommended Subcutaneous Dosage Regimen:

Patients less than 100 kg weight | 162 mg administered subcutaneously every other week, followed by an increase to every week based on clinical response
Patients at or above 100 kg weight | 162 mg administered subcutaneously every week

When transitioning from AVTOZMA intravenous therapy to subcutaneous administration, administer the first subcutaneous dose instead of the next scheduled intravenous dose.

Interruption of dose or reduction in frequency of administration of subcutaneous dose from every week to every other week dosing is recommended for management of certain dose-related laboratory changes including elevated liver enzymes, neutropenia, and thrombocytopenia [see Dosage and Administration (2.10), Warnings and Precautions (5.3, 5.4), and Adverse Reactions (6.2)].

2.3 Recommended Dosage for Giant Cell Arteritis

Recommended Intravenous Dosage Regimen:

The recommended dosage of AVTOZMA for adult patients given as a 60-minute single intravenous drip infusion is 6 mg per kg every 4 weeks in combination with tapering course of glucocorticoids.

AVTOZMA can be used alone following discontinuation of glucocorticoids.

- Interruption of dosing may be needed for management of dose-related laboratory abnormalities including elevated liver enzymes, neutropenia, and thrombocytopenia [see Dosage and Administration (2.10)].
- Doses exceeding 600 mg per infusion are not recommended in GCA patients [see Clinical Pharmacology (12.3)].

Recommended Subcutaneous Dosage Regimen:

The recommended dose of AVTOZMA for adult patients with GCA is 162 mg given once every week as a subcutaneous injection in combination with a tapering course of glucocorticoids.

A dose of 162 mg given once every other week as a subcutaneous injection in combination with a tapering course of glucocorticoids may be prescribed based on clinical considerations.

AVTOZMA can be used alone following discontinuation of glucocorticoids.

When transitioning from AVTOZMA intravenous therapy to subcutaneous administration, administer the first subcutaneous dose instead of the next scheduled intravenous dose.

Interruption of dose or reduction in frequency of administration of subcutaneous dose from every week to every other week dosing may be needed for management of dose-related laboratory abnormalities including elevated liver enzymes, neutropenia, and thrombocytopenia [see Dosage and Administration (2.10)].

2.4 Recommended Dosage for Polyarticular Juvenile Idiopathic Arthritis

AVTOZMA may be used as an intravenous infusion or as a subcutaneous injection alone or in combination with methotrexate. Do not change dose based solely on a single visit body weight measurement, as weight may fluctuate.

Recommended Intravenous Dosage Regimen:

The recommended dosage of AVTOZMA for PJIA patients given once every 4 weeks as a 60-minute single intravenous drip infusion is:

Recommended Intravenous PJIA Dosage Every 4 Weeks
Patients less than 30 kg weight | 10 mg per kg
Patients at or above 30 kg weight | 8 mg per kg

Recommended Subcutaneous Dosage Regimen:

Recommended Subcutaneous PJIA Dosage
Patients less than 30 kg weight | 162 mg once every 3 weeks
Patients at or above 30 kg weight | 162 mg once every 2 weeks

When transitioning from AVTOZMA intravenous therapy to subcutaneous administration, administer the first subcutaneous dose instead of the next scheduled intravenous dose.

Interruption of dosing may be needed for management of dose-related laboratory abnormalities including elevated liver enzymes, neutropenia, and thrombocytopenia [see Dosage and Administration (2.10)].

2.5 Recommended Dosage for Systemic Juvenile Idiopathic Arthritis

AVTOZMA may be used as an intravenous infusion or as a subcutaneous injection alone or in combination with methotrexate. Do not change a dose based solely on a single visit body weight measurement, as weight may fluctuate.

Recommended Intravenous Dosage Regimen:

The recommended dose of AVTOZMA for SJIA patients given once every 2 weeks as a 60-minute single intravenous drip infusion is:

Recommended Intravenous SJIA Dosage Every 2 Weeks
Patients less than 30 kg weight | 12 mg per kg
Patients at or above 30 kg weight | 8 mg per kg

Recommended Subcutaneous Dosage Regimen:

Recommended Subcutaneous SJIA Dosage
Patients less than 30 kg weight | 162 mg once every two weeks
Patients at or above 30 kg weight | 162 mg once every week

When transitioning from AVTOZMA intravenous therapy to subcutaneous administration, administer the first subcutaneous dose when the next scheduled intravenous dose is due.

Interruption of dosing may be needed for management of dose-related laboratory abnormalities including elevated liver enzymes, neutropenia, and thrombocytopenia [see Dosage and Administration (2.10)].

2.6 Recommended Dosage for Cytokine Release Syndrome (CRS)

Use only the intravenous route for treatment of CRS. The recommended dose of AVTOZMA for treatment of CRS given as a 60-minute intravenous infusion is:

Recommended Intravenous CRS Dosage
Patients less than 30 kg weight | 12 mg per kg
Patients at or above 30 kg weight | 8 mg per kg
Alone or in combination with corticosteroids

• If no clinical improvement in the signs and symptoms of CRS occurs after the first dose, up to 3 additional does of AVTOZMA may be administered. The interval between consecutive doses should be at least 8 hours.
• Doses exceeding 800 mg per infusion are not recommended in CRS patients.
• Subcutaneous administration is not approved for CRS.

2.7 Coronavirus Disease 2019 (COVID-19)

Administer AVTOZMA by intravenous infusion only.

The recommended dosage of AVTOZMA for treatment of adult patients with COVID-19 is 8 mg per kg administered as a single 60-minute intravenous infusion. If clinical signs or symptoms worsen or do not improve after the first dose, one additional infusion of AVTOZMA may be administered at least 8 hours after the initial infusion.

- Doses exceeding 800 mg per infusion are not recommended in patients with COVID-19.
- Subcutaneous administration is not approved for COVID-19.

2.8 Preparation and Administration Instructions for Intravenous Infusion

AVTOZMA for intravenous infusion should be diluted by a healthcare professional using aseptic technique as follows:

- Use a sterile needle and syringe to prepare AVTOZMA.
- Patients less than 30 kg: use a 50 mL infusion bag or bottle of 0.9% or 0.45% Sodium Chloride Injection, USP, and then follow steps 1 and 2 below.
- Patients at or above 30 kg weight: use a 100 mL infusion bag or bottle, and then follow steps 1 and 2 below.
- Step 1. Withdraw a volume of 0.9% or 0.45% Sodium Chloride Injection, USP, equal to the volume of the AVTOZMA injection required for the patient's dose from the infusion bag or bottle [see Dosage and Administration (2.2, 2.4, 2.5, 2.6)].

For Intravenous Use: Volume of AVTOZMA Injection per kg of Body Weight
Dosage | Indication | Volume of AVTOZMA injection per kg of body weight
4 mg/kg | Adult RA | 0.2 mL/kg
6 mg/kg | Adult GCA | 0.3 mL/kg
8 mg/kg | Adult RA Adult COVID-19 SJIA, PJIA and CRS (greater than or equal to 30 kg of body weight) | 0.4 mL/kg
10 mg/kg | PJIA (less than 30 kg of body weight) | 0.5 mL/kg
12 mg/kg | SJIA and CRS (less than 30 kg of body weight) | 0.6 mL/kg

- Step 2. Withdraw the amount of AVTOZMA for intravenous infusion from the vial(s) and add slowly into the 0.9% or 0.45% Sodium Chloride Injection, USP infusion bag or bottle. To mix the solution, gently invert the bag to avoid foaming.
- The fully diluted AVTOZMA solutions for infusion using 0.9% Sodium Chloride Injection, USP may be stored at 36°F to 46°F (2°C to 8°C) for up to 48 hours or room temperature up to 86°F (30°C) for up to 4 hours and should be protected from light.
- The fully diluted AVTOZMA solutions for infusion using 0.45% Sodium Chloride Injection, USP may be stored at 36°F to 46°F (2°C to 8°C) for up to 48 hours or room temperature up to 86°F (30°C) for up to 4 hours and should be protected from light.
- AVTOZMA solutions do not contain preservatives; therefore, unused product remaining in the vials should not be used.
- Allow the fully diluted AVTOZMA solution to reach room temperature prior to infusion.
- The infusion should be administered over 60 minutes, and must be administered with an infusion set. Do not administer as an intravenous push or bolus.
- AVTOZMA should not be infused concomitantly in the same intravenous line with other drugs. No physical or biochemical compatibility studies have been conducted to evaluate the co-administration of AVTOZMA with other drugs.
- Parenteral drug products should be inspected visually for particulate matter and discoloration prior to administration, whenever solution and container permit. If particulates and discolorations are noted, the product should not be used.
- Fully diluted AVTOZMA solutions are compatible with polypropylene, polyethylene and polyvinyl chloride infusion bags and polypropylene, polyethylene and glass infusion bottles.

2.9 Preparation and Administration Instructions for Subcutaneous Injection

- AVTOZMA for subcutaneous injection is not intended for intravenous drip infusion.
  Assess suitability of patient for subcutaneous home use and instruct patients to inform a healthcare professional before administering the next dose if they experience any symptoms of allergic reaction. Patients should seek immediate medical attention if they develop symptoms of serious allergic reactions. AVTOZMA subcutaneous injection is intended for use under the guidance of a healthcare practitioner. After proper training in subcutaneous injection technique, a patient may self-inject AVTOZMA or the patient's caregiver may administer AVTOZMA if a healthcare practitioner determines that it is appropriate. PJIA and SJIA patients may self-inject with the AVTOZMA prefilled syringe or prefilled autoinjector, or the patient's caregiver may administer AVTOZMA if both the healthcare practitioner and the parent/legal guardian determines it is appropriate [see Use in Specific Populations (8.4)]. Patients, or patient caregivers, should be instructed to follow the directions provided in the Instructions for Use (IFU) for additional details on medication administration.
- Parenteral drug products should be inspected visually for particulate matter and discoloration prior to administration. Do not use AVTOZMA prefilled syringes (PFS) or prefilled autoinjector (AI) exhibiting particulate matter, cloudiness, or discoloration. AVTOZMA for subcutaneous administration should be clear to slightly opalescent and colorless to yellow. Do not use if any part of the PFS or AI appears to be damaged.
- Patients using AVTOZMA for subcutaneous administration should be instructed to inject the full amount in the syringe (0.9 mL) or full amount in the autoinjector (0.9 mL), which provides 162 mg of AVTOZMA, according to the directions provided in the IFU.
- Injection sites should be rotated with each injection and should never be given into moles, scars, or areas where the skin is tender, bruised, red, hard, or not intact.

2.10 Dosage Modifications due to Serious Infections or Laboratory Abnormalities

Serious Infections

Hold AVTOZMA treatment if a patient develops a serious infection until the infection is controlled.

Laboratory Abnormalities

Rheumatoid Arthritis and Giant Cell Arteritis

Liver Enzyme Abnormalities [see Warnings and Precautions (5.3, 5.4)]
Lab Value | Recommendation for RA | Recommendation for GCA
Greater than 1 to 3× ULN | Dose modify concomitant DMARDs if appropriate For persistent increases in this range:; - For patients receiving intravenous AVTOZMA, reduce dose to 4 mg per kg or hold AVTOZMA until ALT or AST have normalized - For patients receiving subcutaneous AVTOZMA, reduce injection frequency to every other week or hold dosing until ALT or AST have normalized. Resume AVTOZMA at every other week and increase frequency to every week as clinically appropriate. | Dose modify immunomodulatory agents if appropriate For persistent increases in this range:; - For patients receiving intravenous AVTOZMA, hold AVTOZMA until ALT or AST have normalized - For patients receiving subcutaneous AVTOZMA, reduce injection frequency to every other week or hold dosing until ALT or AST have normalized. Resume AVTOZMA at every other week and increase frequency to every week as clinically appropriate.
Greater than 3 to 5× ULN (confirmed by repeat testing) | Hold AVTOZMA dosing until less than 3× ULN and follow recommendations above for greater than 1 to 3× ULN For persistent increases greater than 3× ULN, discontinue AVTOZMA | Hold AVTOZMA dosing until less than 3× ULN and follow recommendations above for greater than 1 to 3× ULN For persistent increases greater than 3× ULN, discontinue AVTOZMA
Greater than 5× ULN | Discontinue AVTOZMA | Discontinue AVTOZMA

Low Absolute Neutrophil Count (ANC) [see Warnings and Precautions (5.4)]
Lab Value (cells per mm^3) | Recommendation for RA | Recommendation for GCA
ANC greater than 1000 | Maintain dose | Maintain dose
ANC 500 to 1000 | Hold AVTOZMA dosing When ANC greater than 1000 cells per mm^3:; - For patients receiving intravenous AVTOZMA, resume AVTOZMA at 4 mg per kg and increase to 8 mg per kg as clinically appropriate - For patients receiving subcutaneous AVTOZMA, resume AVTOZMA at every other week and increase frequency to every week as clinically appropriate | Hold AVTOZMA dosing When ANC greater than 1000 cells per mm^3:; - For patients receiving intravenous AVTOZMA, resume AVTOZMA at 6 mg per kg - For patients receiving subcutaneous AVTOZMA, resume AVTOZMA at every other week and increase frequency to every week as clinically appropriate
ANC less than 500 | Discontinue AVTOZMA | Discontinue AVTOZMA

Low Platelet Count [see Warnings and Precautions (5.4)]
Lab Value (cells per mm^3) | Recommendation for RA | Recommendation for GCA
50,000 to 100,000 | Hold AVTOZMA dosing When platelet count is greater than 100,000 cells per mm^3:; - For patients receiving intravenous AVTOZMA, resume AVTOZMA at 4 mg per kg and increase to 8 mg per kg as clinically appropriate - For patients receiving subcutaneous AVTOZMA, resume AVTOZMA at every other week and increase frequency to every week as clinically appropriate | Hold AVTOZMA dosing When platelet count is greater than 100,000 cells per mm^3:; - For patients receiving intravenous AVTOZMA, resume AVTOZMA at 6 mg per kg - For patients receiving subcutaneous AVTOZMA, resume AVTOZMA at every other week and increase frequency to every week as clinically appropriate
Less than 50,000 | Discontinue AVTOZMA | Discontinue AVTOZMA

Polyarticular and Systemic Juvenile Idiopathic Arthritis

Dose reduction of tocilizumab products has not been studied in the PJIA and SJIA populations. Dose interruptions of AVTOZMA are recommended for liver enzyme abnormalities, low neutrophil counts, and low platelet counts in patients with PJIA and SJIA at levels similar to what is outlined above for patients with RA and GCA. If appropriate, dose modify or stop concomitant methotrexate and/or other medications and hold AVTOZMA dosing until the clinical situation has been evaluated. In PJIA and SJIA the decision to discontinue AVTOZMA for a laboratory abnormality should be based upon the medical assessment of the individual patient.

3 DOSAGE FORMS AND STRENGTHS

Intravenous Infusion

Injection: 80 mg/4 mL, 200 mg/10 mL, 400 mg/20 mL as a clear to slightly opalescent, colorless to pale yellow solution in 20 mg/mL single-dose vials for further dilution prior to intravenous infusion.

Subcutaneous Injection

Injection: 162 mg/0.9 mL clear to slightly opalescent, colorless to yellow solution in a single-dose prefilled syringe or single-dose prefilled autoinjector.

4 CONTRAINDICATIONS

AVTOZMA is contraindicated in patients with known hypersensitivity to tocilizumab products [see Warnings and Precautions (5.6)].

5 WARNINGS AND PRECAUTIONS

5.1 Serious Infections

Serious and sometimes fatal infections due to bacterial, mycobacterial, invasive fungal, viral, protozoal, or other opportunistic pathogens have been reported in patients receiving immunosuppressive agents including tocilizumab products. The most common serious infections included pneumonia, urinary tract infection, cellulitis, herpes zoster, gastroenteritis, diverticulitis, sepsis and bacterial arthritis [see Adverse Reactions (6.1)]. Among opportunistic infections, tuberculosis, cryptococcus, aspergillosis, candidiasis, and pneumocystosis were reported with tocilizumab products. Other serious infections, not reported in clinical studies, may also occur (e.g., histoplasmosis, coccidioidomycosis, listeriosis). Patients have presented with disseminated rather than localized disease, and were often taking concomitant immunosuppressants such as methotrexate or corticosteroids which in addition to rheumatoid arthritis may predispose them to infections.

Do not administer AVTOZMA in patients with an active infection, including localized infections. The risks and benefits of treatment should be considered prior to initiating AVTOZMA in patients:

- with chronic or recurrent infection;
- who have been exposed to tuberculosis;
- with a history of serious or an opportunistic infection;
- who have resided or traveled in areas of endemic tuberculosis or endemic mycoses; or
- with underlying conditions that may predispose them to infection.

Closely monitor patients for the development of signs and symptoms of infection during and after treatment with AVTOZMA, as signs and symptoms of acute inflammation may be lessened due to suppression of the acute phase reactants [see Dosage and Administration (2.10), Adverse Reactions (6.1), and Patient Counseling Information (17)].

Hold AVTOZMA if a patient develops a serious infection, an opportunistic infection, or sepsis. A patient who develops a new infection during treatment with AVTOZMA should undergo a prompt and complete diagnostic workup appropriate for an immunocompromised patient, initiate appropriate antimicrobial therapy, and closely monitor the patient.

COVID-19

In patients with COVID-19, monitor for signs and symptoms of new infections during and after treatment with AVTOZMA. There is limited information regarding the use of tocilizumab products in patients with COVID-19 and concomitant active serious infections. The risks and benefits of treatment with AVTOZMA in COVID-19 patients with other concurrent infections should be considered.

Tuberculosis

Evaluate patients for tuberculosis risk factors and test for latent infection prior to initiating AVTOZMA. In patients with COVID-19, testing for latent infection is not necessary prior to initiating treatment with AVTOZMA.

Consider anti-tuberculosis therapy prior to initiation of AVTOZMA in patients with a past history of latent or active tuberculosis in whom an adequate course of treatment cannot be confirmed, and for patients with a negative test for latent tuberculosis but having risk factors for tuberculosis infection. Consultation with a physician with expertise in the treatment of tuberculosis is recommended to aid in the decision whether initiating anti- tuberculosis therapy is appropriate for an individual patient.

Closely monitor patients for the development of signs and symptoms of tuberculosis including patients who tested negative for latent tuberculosis infection prior to initiating therapy.

The incidence of tuberculosis in worldwide clinical development programs is 0.1%. Patients with latent tuberculosis should be treated with standard antimycobacterial therapy before initiating AVTOZMA.

Viral Reactivation

Viral reactivation has been reported with immunosuppressive biologic therapies and cases of herpes zoster exacerbation were observed in clinical studies with tocilizumab. No cases of Hepatitis B reactivation were observed in the trials; however patients who screened positive for hepatitis were excluded.

5.2 Gastrointestinal Perforations

Events of gastrointestinal perforation have been reported in clinical trials, primarily as complications of diverticulitis in patients treated with tocilizumab. Use AVTOZMA with caution in patients who may be at increased risk for gastrointestinal perforation. Promptly evaluate patients presenting with fever, new onset abdominal symptoms, and a change in bowel habits for early identification of gastrointestinal perforation [see Adverse Reactions (6.1)].

5.3 Hepatotoxicity

Serious cases of hepatic injury have been observed in patients taking intravenous or subcutaneous tocilizumab products. Some of these cases have resulted in liver transplant or death. Time to onset for cases ranged from months to years after treatment initiation with tocilizumab products. While most cases presented with marked elevations of transaminases (> 5 times ULN), some cases presented with signs or symptoms of liver dysfunction and only mildly elevated transaminases.

During randomized controlled studies, treatment with tocilizumab was associated with a higher incidence of transaminase elevations [see Adverse Reactions (6.1, 6.2, 6.5, 6.7)]. Increased frequency and magnitude of these elevations was observed when potentially hepatotoxic drugs (e.g., MTX) were used in combination with tocilizumab.

For RA and GCA patients, obtain a liver test panel (serum alanine aminotransferase [ALT], aspartate aminotransferase [AST], alkaline phosphatase, and total bilirubin) before initiating AVTOZMA, every 4 to 8 weeks after start of therapy for the first 6 months of treatment and every 3 months thereafter. It is not recommended to initiate AVTOZMA treatment in RA or GCA patients with elevated transaminases ALT or AST greater than 1.5× ULN. In patients who develop elevated ALT or AST greater than 5× ULN, discontinue AVTOZMA. For recommended modifications based upon increase in transaminases see Dosage and Administration. (2.10)

Patients hospitalized with COVID-19 may have elevated ALT or AST levels. Multi-organ failure with involvement of the liver is recognized as a complication of severe COVID-19. The decision to administer AVTOZMA should balance the potential benefit of treating COVID-19 against the potential risks of acute treatment with AVTOZMA. It is not recommended to initiate AVTOZMA treatment in COVID-19 patients with elevated ALT or AST above 10 × ULN. Monitor ALT and AST during treatment.

Measure liver tests promptly in patients who report symptoms that may indicate liver injury, such as fatigue, anorexia, right upper abdominal discomfort, dark urine or jaundice. In this clinical context, if the patient is found to have abnormal liver tests (e.g., ALT greater than three times the upper limit of the reference range, serum total bilirubin greater than two times the upper limit of the reference range), AVTOZMA treatment should be interrupted and investigation done to establish the probable cause. AVTOZMA should only be restarted in patients with another explanation for the liver test abnormalities after normalization of the liver tests.

A similar pattern of liver enzyme elevation is noted with tocilizumab products treatment in the PJIA and SJIA populations. Monitor liver test panel at the time of the second administration and thereafter every 4 to 8 weeks for PJIA and every 2 to 4 weeks for SJIA.

5.4 Changes in Laboratory Parameters

Patients with Rheumatoid Arthritis, Giant Cell Arteritis and Coronavirus Disease 2019

Neutropenia

Treatment with tocilizumab products was associated with a higher incidence of neutropenia. Infections have been uncommonly reported in association with treatment-related neutropenia in long-term extension studies and postmarketing clinical experience.

–It is not recommended to initiate AVTOZMA treatment in RA and GCA patients with a low neutrophil count, i.e., absolute neutrophil count (ANC) less than 2000 per mm^3. In patients who develop an absolute neutrophil count less than 500 per mm^3 treatment is not recommended.–Monitor neutrophils 4 to 8 weeks after start of therapy and every 3 months thereafter [see Clinical Pharmacology (12.2)]. For recommended modifications based on ANC results see Dosage and Administration (2.10).

–It is not recommended to initiate AVTOZMA treatment in COVID-19 patients with an ANC less than 1000 per mm^3. Neutrophils should be monitored.

Thrombocytopenia

Treatment with tocilizumab products was associated with a reduction in platelet counts. Treatment-related reduction in platelets was not associated with serious bleeding events in clinical trials [see Adverse Reactions (6.1, 6.2)].

–It is not recommended to initiate AVTOZMA treatment in RA and GCA patients with a platelet count below 100,000 per mm^3. In patients who develop a platelet count less than 50,000 per mm^3 treatment is not recommended.–Monitor platelets 4 to 8 weeks after start of therapy and every 3 months thereafter. For recommended modifications based on platelet counts see Dosage and Administration (2.10).–In COVID-19 patients with a platelet count less than 50,000 per mm^3, treatment is not recommended. Platelets should be monitored.

Elevated Liver Enzymes

Refer to 5.3 Hepatotoxicity. For recommended modifications [see Dosage and Administration (2.10)]

Lipid Abnormalities

Treatment with tocilizumab products was associated with increases in lipid parameters such as total cholesterol, triglycerides, LDL cholesterol, and/or HDL cholesterol [see Adverse Reactions (6.1, 6.2)].

-Assess lipid parameters approximately 4 to 8 weeks following initiation of AVTOZMA therapy.–Subsequently, manage patients according to clinical guidelines [e.g., National Cholesterol Educational Program (NCEP)] for the management of hyperlipidemia.

Patients with Polyarticular and Systemic Juvenile Idiopathic Arthritis

A similar pattern of liver enzyme elevation, low neutrophil count, low platelet count and lipid elevations is noted with tocilizumab products treatment in the PJIA and SJIA populations. Monitor neutrophils, platelets, ALT and AST at the time of the second administration and thereafter every 4 to 8 weeks for PJIA and every 2 to 4 weeks for SJIA. Monitor lipids as above for approved adult indications [see Dosage and Administration (2.10)].

5.5 Immunosuppression

The impact of treatment with tocilizumab products on the development of malignancies is not known but malignancies were observed in clinical studies [see Adverse Reactions (6.1)]. AVTOZMA is an immunosuppressant, and treatment with immunosuppressants may result in an increased risk of malignancies.

5.6 Hypersensitivity Reactions, Including Anaphylaxis

Hypersensitivity reactions, including anaphylaxis, have been reported in association with tocilizumab products and anaphylactic events with a fatal outcome have been reported with intravenous infusion of tocilizumab products. Anaphylaxis and other hypersensitivity reactions that required treatment discontinuation were reported in 0.1% (3 out of 2644) of patients in the 6-month controlled trials of intravenous tocilizumab, 0.2% (8 out of 4009) of patients in the intravenous all-exposure RA population, 0.7% (8 out of 1068) in the subcutaneous 6-month controlled RA trials, and in 0.7% (10 out of 1465) of patients in the subcutaneous all- exposure population. In the SJIA controlled trial with intravenous tocilizumab, 1 out of 112 patients (0.9%) experienced hypersensitivity reactions that required treatment discontinuation. In the PJIA controlled trial with intravenous tocilizumab, 0 out of 188 patients (0%) in the tocilizumab all-exposure population experienced hypersensitivity reactions that required treatment discontinuation. Reactions that required treatment discontinuation included generalized erythema, rash, and urticaria. Injection site reactions were categorized separately [see Adverse Reactions (6)].

In the postmarketing setting, events of hypersensitivity reactions, including anaphylaxis and death have occurred in patients treated with a range of doses of intravenous tocilizumab products, with or without concomitant therapies. Events have occurred in patients who received premedication. Hypersensitivity, including anaphylaxis events, have occurred both with and without previous hypersensitivity reactions and as early as the first infusion of tocilizumab products [see Adverse Reactions (6.10)]. In addition, serious cutaneous reactions, including Drug Reaction with Eosinophilia and Systemic Symptoms (DRESS), have been reported in patients with autoinflammatory conditions treated with tocilizumab products.

AVTOZMA for intravenous use should only be infused by a healthcare professional with appropriate medical support to manage anaphylaxis. For AVTOZMA subcutaneous injection, advise patients to seek immediate medical attention if they experience any symptoms of a hypersensitivity reaction. If a hypersensitivity reaction occurs, immediately discontinue AVTOZMA, treat promptly and monitor until signs and symptoms resolve .

5.7 Demyelinating Disorders

The impact of treatment with tocilizumab products on demyelinating disorders is not known, but multiple sclerosis and chronic inflammatory demyelinating polyneuropathy were reported rarely in RA clinical studies. Monitor patients for signs and symptoms potentially indicative of demyelinating disorders. Prescribers should exercise caution in considering the use of AVTOZMA in patients with preexisting or recent onset demyelinating disorders.

5.8 Active Hepatic Disease and Hepatic Impairment

Treatment with AVTOZMA is not recommended in patients with active hepatic disease or hepatic impairment [see Adverse Reactions (6.1), Use in Specific Populations (8.6)].

5.9 Vaccinations

Avoid use of live vaccines concurrently with AVTOZMA as clinical safety has not been established. No data are available on the secondary transmission of infection from persons receiving live vaccines to patients receiving tocilizumab products.

No data are available on the effectiveness of vaccination in patients receiving tocilizumab products. Because IL-6 inhibition may interfere with the normal immune response to new antigens, it is recommended that all patients, particularly pediatric or elderly patients, if possible, be brought up to date with all immunizations in agreement with current immunization guidelines prior to initiating AVTOZMA therapy. The interval between live vaccinations and initiation of AVTOZMA therapy should be in accordance with current vaccination guidelines regarding immunosuppressive agents.

6 ADVERSE REACTIONS

The following serious adverse reactions are described elsewhere in labeling:

- Serious Infections [see Warnings and Precautions (5.1)]
- Gastrointestinal Perforations [see Warnings and Precautions (5.2)]
- Laboratory Parameters [see Warnings and Precautions (5.4)]
- Immunosuppression [see Warnings and Precautions (5.5)]
- Hypersensitivity Reactions, Including Anaphylaxis [see Warnings and Precautions (5.6)]
- Demyelinating Disorders [see Warnings and Precautions (5.7)]
- Active Hepatic Disease and Hepatic Impairment [see Warnings and Precautions (5.8)]

Because clinical studies are conducted under widely varying conditions, adverse reaction rates observed in the clinical studies of a drug cannot be directly compared to rates in the clinical studies of another drug and may not predict the rates observed in a broader patient population in clinical practice.

6.1 Clinical Trials Experience in Rheumatoid Arthritis Patients Treated with Intravenous Tocilizumab (Tocilizumab-IV)

The tocilizumab-IV data in rheumatoid arthritis (RA) includes 5 double-blind, controlled, multicenter studies. In these studies, patients received doses of tocilizumab-IV 8 mg per kg monotherapy (288 patients), tocilizumab- IV 8 mg per kg in combination with DMARDs (including methotrexate) (1582 patients), or tocilizumab-IV 4 mg per kg in combination with methotrexate (774 patients).

The all exposure population includes all patients in registration studies who received at least one dose of tocilizumab-IV. Of the 4009 patients in this population, 3577 received treatment for at least 6 months, 3309 for at least one year; 2954 received treatment for at least 2 years and 2189 for 3 years.

All patients in these studies had moderately to severely active rheumatoid arthritis. The study population had a mean age of 52 years, 82% were female and 74% were Caucasian.

The most common serious adverse reactions were serious infections [see Warnings and Precautions (5.1)]. The most commonly reported adverse reactions in controlled studies up to 24 weeks (occurring in at least 5% of patients treated with tocilizumab-IV monotherapy or in combination with DMARDs) were upper respiratory tract infections, nasopharyngitis, headache, hypertension and increased ALT.

The proportion of patients who discontinued treatment due to any adverse reactions during the double-blind, placebo-controlled studies was 5% for patients taking tocilizumab-IV and 3% for placebo-treated patients. The most common adverse reactions that required discontinuation of tocilizumab-IV were increased hepatic transaminase values (per protocol requirement) and serious infections.

Overall Infections

In the 24 week, controlled clinical studies, the rate of infections in the tocilizumab-IV monotherapy group was 119 events per 100 patient-years and was similar in the methotrexate monotherapy group. The rate of infections in the 4 mg per kg and 8 mg per kg tocilizumab-IV plus DMARD group was 133 and 127 events per 100 patient- years, respectively, compared to 112 events per 100 patient-years in the placebo plus DMARD group. The most commonly reported infections (5% to 8% of patients) were upper respiratory tract infections and nasopharyngitis.

The overall rate of infections with tocilizumab-IV in the all exposure population remained consistent with rates in the controlled periods of the studies.

Serious Infections

In the 24 week, controlled clinical studies, the rate of serious infections in the tocilizumab-IV monotherapy group was 3.6 per 100 patient-years compared to 1.5 per 100 patient-years in the methotrexate group. The rate of serious infections in the 4 mg per kg and 8 mg per kg tocilizumab-IV plus DMARD group was 4.4 and 5.3 events per 100 patient-years, respectively, compared to 3.9 events per 100 patient-years in the placebo plus DMARD group.

In the all-exposure population, the overall rate of serious infections remained consistent with rates in the controlled periods of the studies. The most common serious infections included pneumonia, urinary tract infection, cellulitis, herpes zoster, gastroenteritis, diverticulitis, sepsis and bacterial arthritis. Cases of opportunistic infections have been reported [see Warnings and Precautions (5.1)].

In the cardiovascular outcomes Study WA25204, the rate of serious infections in the tocilizumab 8 mg/kg IV every 4 weeks group, with or without DMARD, was 4.5 per 100 patient-years, and the rate in the etanercept 50 mg weekly SC group, with or without DMARD, was 3.2 per 100 patient-years [see Clinical Studies (14.1)].

Gastrointestinal Perforations

During the 24 week, controlled clinical trials, the overall rate of gastrointestinal perforation was 0.26 events per 100 patient-years with tocilizumab-IV therapy.

In the all-exposure population, the overall rate of gastrointestinal perforation remained consistent with rates in the controlled periods of the studies. Reports of gastrointestinal perforation were primarily reported as complications of diverticulitis including generalized purulent peritonitis, lower GI perforation, fistula and abscess. Most patients who developed gastrointestinal perforations were taking concomitant nonsteroidal anti- inflammatory medications (NSAIDs), corticosteroids, or methotrexate [see Warnings and Precautions (5.2)]. The relative contribution of these concomitant medications versus tocilizumab-IV to the development of GI perforations is not known.

Infusion Reactions

In the 24 week, controlled clinical studies, adverse events associated with the infusion (occurring during or within 24 hours of the start of infusion) were reported in 8% and 7% of patients in the 4 mg per kg and 8 mg per kg tocilizumab-IV plus DMARD group, respectively, compared to 5% of patients in the placebo plus DMARD group. The most frequently reported event on the 4 mg per kg and 8 mg per kg dose during the infusion was hypertension (1% for both doses), while the most frequently reported event occurring within 24 hours of finishing an infusion were headache (1% for both doses) and skin reactions (1% for both doses), including rash, pruritus and urticaria. These events were not treatment limiting.

Anaphylaxis

Hypersensitivity reactions requiring treatment discontinuation, including anaphylaxis, associated with tocilizumab-IV were reported in 0.1% (3 out of 2644) in the 24 week, controlled trials and in 0.2% (8 out of 4009) in the all-exposure population. These reactions were generally observed during the second to fourth infusion of tocilizumab-IV. Appropriate medical treatment should be available for immediate use in the event of a serious hypersensitivity reaction [see Warnings and Precautions (5.6)].

Laboratory Abnormalities

Neutropenia

In the 24 week, controlled clinical studies, decreases in neutrophil counts below 1000 per mm^3 occurred in 1.8% and 3.4% of patients in the 4 mg per kg and 8 mg per kg tocilizumab-IV plus DMARD group, respectively, compared to 0.1% of patients in the placebo plus DMARD group. Approximately half of the instances of ANC below 1000 per mm^3 occurred within 8 weeks of starting therapy. Decreases in neutrophil counts below 500 per mm^3 occurred in 0.4% and 0.3% of patients in the 4 mg per kg and 8 mg per kg tocilizumab-IV plus DMARD, respectively, compared to 0.1% of patients in the placebo plus DMARD group. There was no clear relationship between decreases in neutrophils below 1000 per mm^3 and the occurrence of serious infections.

In the all-exposure population, the pattern and incidence of decreases in neutrophil counts remained consistent with what was seen in the 24 week controlled clinical studies [see Warnings and Precautions (5.4)].

Thrombocytopenia

In the 24 week, controlled clinical studies, decreases in platelet counts below 100,000 per mm^3 occurred in 1.3% and 1.7% of patients on 4 mg per kg and 8 mg per kg tocilizumab-IV plus DMARD, respectively, compared to 0.5% of patients on placebo plus DMARD, without associated bleeding events.

In the all-exposure population, the pattern and incidence of decreases in platelet counts remained consistent with what was seen in the 24 week controlled clinical studies [see Warnings and Precautions (5.4)].

Elevated Liver Enzymes

Liver enzyme abnormalities are summarized in Table 1. In patients experiencing liver enzyme elevation, modification of treatment regimen, such as reduction in the dose of concomitant DMARD, interruption of tocilizumab-IV, or reduction in tocilizumab-IV dose, resulted in decrease or normalization of liver enzymes [see Dosage and Administration (2.10)]. These elevations were not associated with clinically relevant increases in direct bilirubin, nor were they associated with clinical evidence of hepatitis or hepatic insufficiency [see Warnings and Precautions (5.3, 5.4)].

Table 1 Incidence of Liver Enzyme Abnormalities in the 24 Week Controlled Period of Studies I to V [For a description of these studies, see Section 14, Clinical Studies.]
 | Tocilizumab 8 mg per kg MONOTHERAPY | Methotrexate | Tocilizumab 4 mg per kg + DMARDs | Tocilizumab 8 mg per kg + DMARDs | Placebo + DMARDs
 | N = 288 (%) | N = 284 (%) | N = 774 (%) | N = 1582 (%) | N = 1170 (%)
ULN = Upper Limit of Normal
AST (U/L)
> ULN to 3× ULN | 22 | 26 | 34 | 41 | 17
> 3× ULN to 5× ULN | 0.3 | 2 | 1 | 2 | 0.3
> 5× ULN | 0.7 | 0.4 | 0.1 | 0.2 | < 0.1
ALT (U/L)
> ULN to 3× ULN | 36 | 33 | 45 | 48 | 23
> 3× ULN to 5× ULN | 1 | 4 | 5 | 5 | 1
> 5× ULN | 0.7 | 1 | 1.3 | 1.5 | 0.3

In the all-exposure population, the elevations in ALT and AST remained consistent with what was seen in the 24 week, controlled clinical trials.

In Study WA25204, of the 1538 patients with moderate to severe RA [see Clinical Studies (14.1)] and treated with tocilizumab, elevations in ALT or AST >3 × ULN occurred in 5.3% and 2.2% patients, respectively. One serious event of drug induced hepatitis with hyperbilirubinemia was reported in association with tocilizumab.

Lipids

Elevations in lipid parameters (total cholesterol, LDL, HDL, triglycerides) were first assessed at 6 weeks following initiation of tocilizumab-IV in the controlled 24 week clinical trials. Increases were observed at this time point and remained stable thereafter. Increases in triglycerides to levels above 500 mg per dL were rarely observed. Changes in other lipid parameters from baseline to week 24 were evaluated and are summarized below:

- Mean LDL increased by 13 mg per dL in the tocilizumab 4 mg per kg+DMARD arm, 20 mg per dL in the tocilizumab 8 mg per kg+DMARD, and 25 mg per dL in tocilizumab 8 mg per kg monotherapy.
- Mean HDL increased by 3 mg per dL in the tocilizumab 4 mg per kg+DMARD arm, 5 mg per dL in the tocilizumab 8 mg per kg+DMARD, and 4 mg per dL in tocilizumab 8 mg per kg monotherapy.
- Mean LDL/HDL ratio increased by an average of 0.14 in the tocilizumab 4 mg per kg+DMARD arm, 0.15 in the tocilizumab 8 mg per kg+DMARD, and 0.26 in tocilizumab 8 mg per kg monotherapy.
- ApoB/ApoA1 ratios were essentially unchanged in tocilizumab-treated patients.

Elevated lipids responded to lipid lowering agents.

In the all-exposure population, the elevations in lipid parameters remained consistent with what was seen in the 24 week, controlled clinical trials.

Immunogenicity

The observed incidence of anti-drug antibodies is highly dependent on the sensitivity and specificity of the assay. Differences in assay methods preclude meaningful comparisons of the incidence of anti-drug antibodies in the studies described below with the incidence of anti-drug antibodies in other studies, including those of tocilizumab or of other tocilizumab products.

In the 24 week, controlled clinical studies, a total of 2876 patients have been tested for anti-tocilizumab antibodies. Forty-six patients (2%) developed positive anti-tocilizumab antibodies, of whom 5 had an associated, medically significant, hypersensitivity reaction leading to withdrawal. Thirty patients (1%) developed neutralizing antibodies.

Malignancies

During the 24 week, controlled period of the studies, 15 malignancies were diagnosed in patients receiving tocilizumab-IV, compared to 8 malignancies in patients in the control groups. Exposure-adjusted incidence was similar in the tocilizumab-IV groups (1.32 events per 100 patient-years) and in the placebo plus DMARD group (1.37 events per 100 patient-years).

In the all-exposure population, the rate of malignancies remained consistent with the rate observed in the 24 week, controlled period [see Warnings and Precautions (5.5)].

Other Adverse Reactions

Adverse reactions occurring in 2% or more of patients on 4 or 8 mg per kg tocilizumab-IV plus DMARD and at least 1% greater than that observed in patients on placebo plus DMARD are summarized in Table 2.

Table 2 Adverse Reactions Occurring in at Least 2% or More of Patients on 4 or 8 mg per kg Tocilizumab plus DMARD and at Least 1% Greater Than That Observed in Patients on Placebo plus DMARD
24 Week Phase 3 Controlled Study Population
 | Tocilizumab 8 mg per kg MONOTHERAPY | Methotrexate | Tocilizumab 4 mg per kg + DMARDs | Tocilizumab 8 mg per kg + DMARDs | Placebo + DMARDs
Preferred Term | N = 288 (%) | N = 284 (%) | N = 774 (%) | N = 1582 (%) | N = 1170 (%)
Upper Respiratory Tract Infection | 7 | 5 | 6 | 8 | 6
Nasopharyngitis | 7 | 6 | 4 | 6 | 4
Headache | 7 | 2 | 6 | 5 | 3
Hypertension | 6 | 2 | 4 | 4 | 3
ALT increased | 6 | 4 | 3 | 3 | 1
Dizziness | 3 | 1 | 2 | 3 | 2
Bronchitis | 3 | 2 | 4 | 3 | 3
Rash | 2 | 1 | 4 | 3 | 1
Mouth Ulceration | 2 | 2 | 1 | 2 | 1
Abdominal Pain Upper | 2 | 2 | 3 | 3 | 2
Gastritis | 1 | 2 | 1 | 2 | 1
Transaminase increased | 1 | 5 | 2 | 2 | 1

Other infrequent and medically relevant adverse reactions occurring at an incidence less than 2% in rheumatoid arthritis patients treated with tocilizumab-IV in controlled trials were:

Infections and Infestations: oral herpes simplex

Gastrointestinal disorders: stomatitis, gastric ulcer

Investigations: weight increased, total bilirubin increased

Blood and lymphatic system disorders: leukopenia

General disorders and administration site conditions: edema peripheral

Respiratory, thoracic, and mediastinal disorders: dyspnea, cough

Eye disorders: conjunctivitis

Renal disorders: nephrolithiasis

Endocrine disorders: hypothyroidism

6.2 Clinical Trials Experience in Rheumatoid Arthritis Patients Treated with Subcutaneous Tocilizumab (Tocilizumab-SC)

The tocilizumab-SC data in rheumatoid arthritis (RA) includes 2 double-blind, controlled, multicenter studies. Study SC-I was a non-inferiority study that compared the efficacy and safety of tocilizumab 162 mg administered every week subcutaneously and 8 mg/kg intravenously every four weeks in 1262 adult subjects with rheumatoid arthritis. Study SC-II was a placebo controlled superiority study that evaluated the safety and efficacy of tocilizumab 162 mg administered every other week subcutaneously or placebo in 656 patients. All patients in both studies received background non-biologic DMARDs.

The safety observed for tocilizumab-SC administered subcutaneously was consistent with the known safety profile of intravenous tocilizumab, with the exception of injection site reactions (ISRs), which were more common with tocilizumab-SC compared with placebo SC injections (IV arm).

Injection Site Reactions

In the 6-month control period, in SC-I, the frequency of ISRs was 10.1% (64/631) and 2.4% (15/631) for the weekly tocilizumab-SC and placebo SC (IV-arm) groups, respectively. In SC-II, the frequency of ISRs was 7.1% (31/437) and 4.1% (9/218) for the every other week tocilizumab-SC and placebo groups, respectively. These ISRs (including erythema, pruritus, pain and hematoma) were mild to moderate in severity. The majority resolved without any treatment and none necessitated drug discontinuation.

Immunogenicity

In the 6-month control period in SC-I, 0.8% (5/625) in the tocilizumab-SC arm and 0.8% (5/627) in the IV arm developed anti-tocilizumab antibodies; of these, all developed neutralizing antibodies. In SC-II, 1.6% (7/434) in the tocilizumab-SC arm compared with 1.4 % (3/217) in the placebo arm developed anti- tocilizumab antibodies; of these, 1.4% (6/434) in the tocilizumab-SC arm and 0.5% (1/217) in the placebo arm also developed neutralizing antibodies.

A total of 1454 (>99%) patients who received tocilizumab-SC in the all exposure group have been tested for anti- tocilizumab antibodies. Thirteen patients (0.9%) developed anti-tocilizumab antibodies, and, of these, 12 patients (0.8%) developed neutralizing antibodies.

The rate is consistent with previous intravenous experience. No correlation of antibody development to adverse events or loss of clinical response was observed.

Laboratory Abnormalities

Neutropenia

During routine laboratory monitoring in the 6-month controlled clinical trials, a decrease in neutrophil count below 1 × 10^9/L occurred in 2.9% and 3.7% of patients receiving tocilizumab-SC weekly and every other week, respectively.

There was no clear relationship between decreases in neutrophils below 1 × 10^9/L and the occurrence of serious infections.

Thrombocytopenia

During routine laboratory monitoring in the tocilizumab-SC 6-month controlled clinical trials, none of the patients had a decrease in platelet count to ≤50,000/mm^3.

Elevated Liver Enzymes

During routine laboratory monitoring in the 6-month controlled clinical trials, elevation in ALT or AST ≥3 × ULN occurred in 6.5% and 1.4% of patients, respectively, receiving tocilizumab-SC weekly and 3.4% and 0.7% receiving tocilizumab-SC every other week.

Lipid Parameters Elevations

During routine laboratory monitoring in the tocilizumab-SC 6-month clinical trials, 19% of patients dosed weekly and 19.6% of patients dosed every other week and 10.2% of patients on placebo experienced sustained elevations in total cholesterol > 6.2 mmol/l (240 mg/dL), with 9%, 10.4% and 5.1% experiencing a sustained increase in LDL to 4.1 mmol/l (160 mg/dL) receiving tocilizumab-SC weekly, every other week and placebo, respectively.

6.3 Clinical Trials Experience in Giant Cell Arteritis Patients Treated with Subcutaneous Tocilizumab (Tocilizumab-SC)

The safety of subcutaneous tocilizumab has been studied in one Phase III study (WA28119) with 251 GCA patients. The total patient years duration in the tocilizumab-SC GCA all exposure population was 138.5 patient years during the 12-month double blind, placebo-controlled phase of the study. The overall safety profile observed in the tocilizumab-SC treatment groups was generally consistent with the known safety profile of tocilizumab. There was an overall higher incidence of infections in GCA patients relative to RA patients. The rate of infection/serious infection events was 200.2/9.7 events per 100 patient years in the tocilizumab-SC weekly group and 160.2/4.4 events per 100 patient years in the tocilizumab-SC every other week group as compared to 156.0/4.2 events per 100 patient years in the placebo + 26 week prednisone taper and 210.2/12.5 events per 100 patient years in the placebo + 52 week taper groups.

6.4 Clinical Trials Experience in Giant Cell Arteritis Patients Treated with Intravenous Tocilizumab (Tocilizumab-IV)

The safety of tocilizumab-IV was studied in an open label PK-PD and safety study in 24 patients with GCA who were in remission on tocilizumab-IV at time of enrollment. Patients received tocilizumab 7 mg/kg every 4 weeks for 20 weeks, followed by 6 mg/kg every 4 weeks for 20 weeks. The total patient years exposure to treatment was 17.5 years. The overall safety profile observed for tocilizumab administered intravenously in GCA patients was consistent with the known safety profile of tocilizumab.

6.5 Clinical Trials Experience in Polyarticular Juvenile Idiopathic Arthritis Patients Treated with Intravenous Tocilizumab (Tocilizumab-IV)

The safety of tocilizumab-IV was studied in 188 pediatric patients 2 to 17 years of age with PJIA who had an inadequate clinical response or were intolerant to methotrexate. The total patient exposure in the tocilizumab-IV all exposure population (defined as patients who received at least one dose of tocilizumab-IV) was 184.4 patient years. At baseline, approximately half of the patients were taking oral corticosteroids and almost 80% were taking methotrexate. In general, the types of adverse drug reactions in patients with PJIA were consistent with those seen in RA and SJIA patients [see Adverse Reactions (6.1 and 6.7)].

Infections

The rate of infections in the tocilizumab-IV all exposure population was 163.7 per 100 patient years. The most common events observed were nasopharyngitis and upper respiratory tract infections. The rate of serious infections was numerically higher in patients weighing less than 30 kg treated with 10 mg/kg tocilizumab (12.2 per 100 patient years) compared to patients weighing at or above 30 kg, treated with 8 mg/kg tocilizumab (4.0 per 100 patient years). The incidence of infections leading to dose interruptions was also numerically higher in patients weighing less than 30 kg treated with 10 mg/kg tocilizumab (21%) compared to patients weighing at or above 30 kg, treated with 8 mg/kg tocilizumab (8%).

Infusion Reactions

In PJIA patients, infusion-related reactions are defined as all events occurring during or within 24 hours of an infusion. In the tocilizumab-IV all exposure population, 11 patients (6%) experienced an event during the infusion, and 38 patients (20.2%) experienced an event within 24 hours of an infusion. The most common events occurring during infusion were headache, nausea and hypotension, and occurring within 24 hours of infusion were dizziness and hypotension. In general, the adverse drug reactions observed during or within 24 hours of an infusion were similar in nature to those seen in RA and SJIA patients [see Adverse Reactions (6.1 and 6.7)].

No clinically significant hypersensitivity reactions associated with tocilizumab and requiring treatment discontinuation were reported.

Immunogenicity

One patient, in the 10 mg/kg less than 30 kg group, developed positive anti-tocilizumab antibodies without developing a hypersensitivity reaction and subsequently withdrew from the study.

Laboratory Abnormalities

Neutropenia

During routine laboratory monitoring in the tocilizumab-IV all exposure population, a decrease in neutrophil counts below 1 × 10^9 per L occurred in 3.7% of patients.

There was no clear relationship between decreases in neutrophils below 1 × 10^9 per L and the occurrence of serious infections.

Thrombocytopenia

During routine laboratory monitoring in the tocilizumab-IV all exposure population, 1% of patients had a decrease in platelet count at or less than 50,000 per mm^3 without associated bleeding events.

Elevated Liver Enzymes

During routine laboratory monitoring in the tocilizumab-IV all exposure population, elevation in ALT or AST at or greater than 3 × ULN occurred in 4% and less than 1% of patients, respectively.

Lipids

During routine laboratory monitoring in the tocilizumab all exposure population, elevation in total cholesterol greater than 1.5-2 × ULN occurred in one patient (0.5%) and elevation in LDL greater than 1.5-2 × ULN occurred in one patient (0.5%).

6.6 Clinical Trials Experience in Polyarticular Juvenile Idiopathic Arthritis Patients Treated with Subcutaneous Tocilizumab (Tocilizumab-SC)

The safety of tocilizumab-SC was studied in 52 pediatric patients 1 to 17 years of age with PJIA who had an inadequate clinical response or were intolerant to methotrexate. The total patient exposure in the PJIA tocilizumab-SC population (defined as patients who received at least one dose of tocilizumab-SC and accounting for treatment discontinuation) was 49.5 patient years. In general, the safety observed for tocilizumab administered subcutaneously was consistent with the known safety profile of intravenous tocilizumab, with the exception of injection site reactions (ISRs), and neutropenia.

Injection Site Reactions

During the 1-year study, a frequency of 28.8% (15/52) ISRs was observed in tocilizumab-SC treated PJIA patients. These ISRs occurred in a greater proportion of patients at or above 30 kg (44.0%) compared with patients below 30 kg (14.8%). All ISRs were mild in severity and none of the ISRs required patient withdrawal from treatment or dose interruption. A higher frequency of ISRs was observed in tocilizumab-SC treated PJIA patients compared to what was seen in adult RA or GCA patients [see Adverse Reactions (6.2 and 6.3)].

Immunogenicity

Three patients, 1 patient below 30 kg and 2 patients at or above 30 kg, developed positive anti-tocilizumab antibodies with neutralizing potential without developing a serious or clinically significant hypersensitivity reaction. One patient subsequently withdrew from the study.

Neutropenia

During routine laboratory monitoring in the tocilizumab-SC all exposure population, a decrease in neutrophil counts below 1 × 10^9 per L occurred in 15.4% of patients, and was more frequently observed in the patients less than 30 kg (25.9%) compared to patients at or above 30 kg (4.0%). There was no clear relationship between decreases in neutrophils below 1 × 10^9 per L and the occurrence of serious infections.

6.7 Clinical Trials Experience in Systemic Juvenile Idiopathic Arthritis Patients Treated with Intravenous Tocilizumab (Tocilizumab-IV)

The data described below reflect exposure to tocilizumab-IV in one randomized, double-blind, placebo- controlled trial of 112 pediatric patients with SJIA 2 to 17 years of age who had an inadequate clinical response to nonsteroidal anti-inflammatory drugs (NSAIDs) or corticosteroids due to toxicity or lack of efficacy. At baseline, approximately half of the patients were taking 0.3 mg/kg/day corticosteroids or more, and almost 70% were taking methotrexate. The trial included a 12 week controlled phase followed by an open-label extension. In the 12 week double-blind, controlled portion of the clinical study 75 patients received treatment with tocilizumab- IV (8 or 12 mg per kg based upon body weight). After 12 weeks or at the time of escape, due to disease worsening, patients were treated with tocilizumab-IV in the open-label extension phase.

The most common adverse events (at least 5%) seen in tocilizumab-IV treated patients in the 12 week controlled portion of the study were: upper respiratory tract infection, headache, nasopharyngitis and diarrhea.

Infections

In the 12 week controlled phase, the rate of all infections in the tocilizumab-IV group was 345 per 100 patient- years and 287 per 100 patient-years in the placebo group. In the open label extension over an average duration of 73 weeks of treatment, the overall rate of infections was 304 per 100 patient-years.

In the 12 week controlled phase, the rate of serious infections in the tocilizumab-IV group was 11.5 per 100 patient years. In the open label extension over an average duration of 73 weeks of treatment, the overall rate of serious infections was 11.4 per 100 patient years. The most commonly reported serious infections included pneumonia, gastroenteritis, varicella, and otitis media.

Macrophage Activation Syndrome

In the 12 week controlled study, no patient in any treatment group experienced macrophage activation syndrome (MAS) while on assigned treatment; 3 per 112 (3%) developed MAS during open-label treatment with tocilizumab-IV. One patient in the placebo group escaped to tocilizumab-IV 12 mg per kg at Week 2 due to severe disease activity, and ultimately developed MAS at Day 70. Two additional patients developed MAS during the long-term extension. All 3 patients had tocilizumab-IV dose interrupted (2 patients) or discontinued (1 patient) for the MAS event, received treatment, and the MAS resolved without sequelae. Based on a limited number of cases, the incidence of MAS does not appear to be elevated in the tocilizumab-IV SJIA clinical development experience; however no definitive conclusions can be made.

Infusion Reactions

Patients were not premedicated, however most patients were on concomitant corticosteroids as part of their background treatment for SJIA. Infusion related reactions were defined as all events occurring during or within 24 hours after an infusion. In the 12 week controlled phase, 4% of tocilizumab-IV and 0% of placebo treated patients experienced events occurring during infusion. One event (angioedema) was considered serious and life- threatening, and the patient was discontinued from study treatment.

Within 24 hours after infusion, 16% of patients in the tocilizumab-IV treatment group and 5% of patients in the placebo group experienced an event. In the tocilizumab-IV group the events included rash, urticaria, diarrhea, epigastric discomfort, arthralgia and headache. One of these events, urticaria, was considered serious.

Anaphylaxis

Anaphylaxis was reported in 1 out of 112 patients (less than 1%) treated with tocilizumab-IV during the controlled and open label extension study [see Warnings and Precautions (5.6)].

Immunogenicity

All 112 patients were tested for anti-tocilizumab antibodies at baseline. Two patients developed positive anti- tocilizumab antibodies: one of these patients experienced serious adverse events of urticaria and angioedema consistent with an anaphylactic reaction which led to withdrawal; the other patient developed macrophage activation syndrome while on escape therapy and was discontinued from the study.

Laboratory Abnormalities

Neutropenia

During routine monitoring in the 12 week controlled phase, a decrease in neutrophil below 1 × 10^9 per L occurred in 7% of patients in the tocilizumab-IV group, and in no patients in the placebo group. In the open label extension over an average duration of 73 weeks of treatment, a decreased neutrophil count occurred in 17% of the tocilizumab-IV group. There was no clear relationship between decrease in neutrophils below 1 × 10^9 per L and the occurrence of serious infections.

Thrombocytopenia

During routine monitoring in the 12 week controlled phase, 1% of patients in the tocilizumab-IV group and 3% in the placebo group had a decrease in platelet count to no more than 100,000 per mm^3.

In the open label extension over an average duration of 73 weeks of treatment, decreased platelet count occurred in 4% of patients in the tocilizumab-IV group, with no associated bleeding.

Elevated Liver Enzymes

During routine laboratory monitoring in the 12 week controlled phase, elevation in ALT or AST at or above 3× ULN occurred in 5% and 3% of patients, respectively in the tocilizumab-IV group and in 0% of placebo patients.

In the open label extension over an average duration of 73 weeks of treatment, the elevation in ALT or AST at or above 3× ULN occurred in 13% and 5% of tocilizumab-IV treated patients, respectively.

Lipids

During routine laboratory monitoring in the 12 week controlled phase, elevation in total cholesterol greater than 1.5× ULN – 2× ULN occurred in 1.5% of the tocilizumab-IV group and in 0% of placebo patients. Elevation in LDL greater than 1.5× ULN – 2× ULN occurred in 1.9% of patients in the tocilizumab-IV group and 0% of the placebo group.

In the open label extension study over an average duration of 73 weeks of treatment, the pattern and incidence of elevations in lipid parameters remained consistent with the 12 week controlled study data.

6.8 Clinical Trials Experience in Systemic Juvenile Idiopathic Arthritis Patients Treated with Subcutaneous Tocilizumab (Tocilizumab-SC)

The safety profile of tocilizumab-SC was studied in 51 pediatric patients 1 to 17 years of age with SJIA who had an inadequate clinical response to NSAIDs and corticosteroids. In general, the safety observed for tocilizumab administered subcutaneously was consistent with the known safety profile of intravenous tocilizumab, with the exception of ISRs where a higher frequency was observed in tocilizumab-SC treated SJIA patients compared to PJIA patients and adult RA or GCA patients [see Adverse Reactions (6.2, 6.3 and 6.6)].

Injection Site Reactions (ISRs)

A total of 41.2% (21/51) SJIA patients experienced ISRs to tocilizumab-SC. The most common ISRs were erythema, pruritus, pain, and swelling at the injection site. The majority of ISRs reported were Grade 1 events and all ISRs reported were non-serious and none required patient withdrawal from treatment or dose interruption.

6.9 Clinical Trials Experience in Patients with Cytokine Release Syndrome Treated with Intravenous AVTOZMA (Tocilizumab-IV)

In a retrospective analysis of pooled outcome data from multiple clinical trials 45 patients were treated with tocilizumab 8 mg/kg (12 mg/kg for patients less than 30 kg) with or without additional high-dose corticosteroids for severe or life-threatening CAR T cell-induced CRS. A median of 1 dose of tocilizumab (range, 1-4 doses) was administered. No adverse reactions related to tocilizumab were reported [see Clinical Studies (14.9)].

6.10 Clinical Trials Experience in COVID-19 Patients Treated with Intravenous Tocilizumab (Tocilizumab-IV)

The safety of tocilizumab in hospitalized COVID-19 patients was evaluated in a pooled safety population that includes patients enrolled in EMPACTA, COVACTA, AND REMDACTA. The analysis of adverse reactions included a total of 974 patients exposed to tocilizumab. Patients received a single, 60-minute infusion of intravenous tocilizumab 8 mg/kg (maximum dose of 800 mg). If clinical signs or symptoms worsened or did not improve, one additional dose of tocilizumab 8 mg/kg could be administered between 8- 24 hours after the initial dose.

Adverse reactions summarized in Table 3 occurred in at least 3% of tocilizumab-treated patients and more commonly than in patients on placebo in the pooled safety population.

Table 3 Adverse Reactions [Patients are counted once for each category regardless of the number of reactions] Identified From the Pooled COVID-19 Safety Population
Adverse Reaction | Tocilizumab 8 mg per kg | Placebo
 | N = 974 (%) | N = 483 (%)
Hepatic Transaminases increased | 10% | 8%
Constipation | 9 % | 8%
Urinary tract infection | 5% | 4%
Hypertension | 4% | 1%
Hypokalaemia | 4% | 3%
Anxiety | 4% | 2%
Diarrhea | 4% | 2%
Insomnia | 4% | 3%
Nausea | 3% | 2%

In the pooled safety population, the rates of infection/serious infection events were 30%/19% in patients receiving tocilizumab versus 32%/23% receiving placebo.

Laboratory Abnormalities

In the pooled safety population of EMPACTA, COVACTA, and REMDACTA, neutrophil counts <1000 cells/mcl occurred in 3.4% of patients who received tocilizumab and 0.5% of patients who received placebo. Platelet counts <50,000 cells/mcl occurred in 3.2% of patients who received tocilizumab and 1.5% of patients who received placebo. ALT or AST at or above 5× ULN occurred in 11.7% of patients who received tocilizumab and 9.9% of patients who received placebo.

6.11 Postmarketing Experience

The following adverse reactions have been identified during post-approval use of tocilizumab products. Because these reactions are reported voluntarily from a population of uncertain size, it is not always possible to reliably estimate their frequency or establish a causal relationship to drug exposure.

- Hypersensitivity Reactions: Fatal anaphylaxis, Stevens-Johnson Syndrome, Drug Reaction with Eosinophilia and Systemic Symptoms (DRESS) [see Warnings and Precautions (5.6)]
- Pancreatitis
- Drug-induced liver injury, Hepatitis, Hepatic failure, Jaundice [see Warnings and Precautions (5.3)]
- Hypofibrinogenemia

7 DRUG INTERACTIONS

7.1 Concomitant Drugs for Treatment of Adult Indications

In RA patients, population pharmacokinetic analyses did not detect any effect of methotrexate (MTX), non- steroidal anti-inflammatory drugs or corticosteroids on tocilizumab clearance. Concomitant administration of a single intravenous dose of 10 mg/kg tocilizumab with 10-25 mg MTX once weekly had no clinically significant effect on MTX exposure. Tocilizumab products have not been studied in combination with biological DMARDs such as TNF antagonists [see Dosage and Administration (2.2)].

In GCA patients, no effect of concomitant corticosteroid on tocilizumab exposure was observed.

7.2 Interactions with CYP450 Substrates

Cytochrome P450s in the liver are down-regulated by infection and inflammation stimuli including cytokines such as IL-6. Inhibition of IL-6 signaling in RA patients treated with tocilizumab products may restore CYP450 activities to higher levels than those in the absence of tocilizumab products leading to increased metabolism of drugs that are CYP450 substrates. In vitro studies showed that tocilizumab has the potential to affect expression of multiple CYP enzymes including CYP1A2, CYP2B6, CYP2C9, CYP2C19, CYP2D6 and CYP3A4. Its effect on CYP2C8 or transporters is unknown. In vivo studies with omeprazole, metabolized by CYP2C19 and CYP3A4, and simvastatin, metabolized by CYP3A4, showed up to a 28% and 57% decrease in exposure one week following a single dose of tocilizumab, respectively. The effect of tocilizumab products on CYP enzymes may be clinically relevant for CYP450 substrates with narrow therapeutic index, where the dose is individually adjusted. Upon initiation or discontinuation of AVTOZMA, in patients being treated with these types of medicinal products, perform therapeutic monitoring of effect (e.g., warfarin) or drug concentration (e.g., cyclosporine or theophylline) and the individual dose of the medicinal product adjusted as needed. Exercise caution when coadministering AVTOZMA with CYP3A4 substrate drugs where decrease in effectiveness is undesirable, e.g., oral contraceptives, lovastatin, atorvastatin, etc. The effect of tocilizumab products on CYP450 enzyme activity may persist for several weeks after stopping therapy [see Clinical Pharmacology (12.3)].

7.3 Live Vaccines

Avoid use of live vaccines concurrently with AVTOZMA [see Warnings and Precautions (5.9)].

8 USE IN SPECIFIC POPULATIONS

8.1 Pregnancy

Risk Summary

The available data with tocilizumab products from a pregnancy exposure registry, retrospective cohort study, pharmacovigilance, and published literature are insufficient to draw conclusions about a drug-associated risk of major birth defects, miscarriage, or other adverse maternal or fetal outcomes. These studies had methodological limitations, including small sample size of tocilizumab exposed groups, missing exposure and outcomes information, and lack of adjustment for cofounders. Monoclonal antibodies, such as tocilizumab products, are actively transported across the placenta during the third trimester of pregnancy and may affect immune response in the in utero exposed infant [see Clinical Considerations]. In animal reproduction studies, intravenous administration of tocilizumab to Cynomolgus monkeys during organogenesis caused abortion/embryo-fetal death at doses 1.25 times and higher than the maximum recommended human dose by the intravenous route of 8 mg per kg every 2 to 4 weeks. The literature in animals suggests that inhibition of IL-6 signaling may interfere with cervical ripening and dilatation and myometrial contractile activity leading to potential delays of parturition [see Data]. Based on the animal data, there may be a potential risk to the fetus.

The estimated background risk of major birth defects and miscarriage for the indicated population is unknown. All pregnancies have a background risk of birth defect, loss or other adverse outcomes. In the U.S. general population, the estimated background risk of major birth defects and miscarriage in clinically recognized pregnancies is 2 to 4% and 15 to 20%, respectively.

Clinical Considerations

Fetal/Neonatal adverse reactions

Monoclonal antibodies are increasingly transported across the placenta as pregnancy progresses, with the largest amount transferred during the third trimester. Risks and benefits should be considered prior to administering live or live-attenuated vaccines to infants exposed to AVTOZMA in utero [see Warnings and Precautions 5.9)].

Disease-associated Maternal Risk

Published data suggest that the risk of adverse pregnancy outcomes in women with rheumatoid arthritis is associated with increased disease activity. Adverse pregnancy outcomes include preterm delivery (before 37 weeks of gestation), low birth weight (less than 2500 g) infants, and small for gestational age at birth.

Data

Animal Data

An embryo-fetal developmental toxicity study was performed in which pregnant Cynomolgus monkeys were treated intravenously with tocilizumab at daily doses of 2, 10, or 50 mg/ kg during organogenesis from gestation day (GD) 20-50. Although there was no evidence for a teratogenic/dysmorphogenic effect at any dose, tocilizumab produced an increase in the incidence of abortion/embryo-fetal death at doses 1.25 times and higher the MRHD by the intravenous route at maternal intravenous doses of 10 and 50 mg/ kg. Testing of a murine analogue of tocilizumab in mice did not yield any evidence of harm to offspring during the pre- and postnatal development phase when dosed at 50 mg/kg intravenously with treatment every three days from implantation (GD 6) until post-partum day 21 (weaning). There was no evidence for any functional impairment of the development and behavior, learning ability, immune competence and fertility of the offspring.

Parturition is associated with significant increases of IL-6 in the cervix and myometrium. The literature suggests that inhibition of IL-6 signaling may interfere with cervical ripening and dilatation and myometrial contractile activity leading to potential delays of parturition. For mice deficient in IL-6 (ll6-/- null mice), parturition was delayed relative to wild-type (ll6+/+) mice. Administration of recombinant IL-6 to ll6-/- null mice restored the normal timing of delivery.

8.2 Lactation

Risk Summary

No information is available on the presence of tocilizumab products in human milk, the effects of the drug on the breastfed infant, or the effects of the drug on milk production. Maternal immunoglobulin G (IgG) is present in human milk. If tocilizumab products are transferred into human milk, the effects of local exposure in the gastrointestinal tract and potential limited systemic exposure in the infant to tocilizumab products are unknown. The lack of clinical data during lactation precludes clear determination of the risk of tocilizumab products to an infant during lactation; therefore the developmental and health benefits of breastfeeding should be considered along with the mother's clinical need for AVTOZMA and the potential adverse effects on the breastfed child from AVTOZMA or from the underlying maternal condition.

8.4 Pediatric Use

AVTOZMA by intravenous use is indicated for the treatment of pediatric patients with:

- Active systemic juvenile idiopathic arthritis in patients 2 years of age and older
- Active polyarticular juvenile idiopathic arthritis in patients 2 years of age and older
- Severe or life-threatening CAR T cell-induced cytokine release syndrome (CRS) in patients with 2 years of age and older.

AVTOZMA by subcutaneous use is indicated for the treatment of pediatric patients with:

- Active polyarticular juvenile idiopathic arthritis in patients 2 years of age and older
- Active systemic juvenile idiopathic arthritis in patients 2 years of age and older

The safety and effectiveness of AVTOZMA in pediatric patients with conditions other than PJIA, SJIA or CRS have not been established. The safety and effectiveness in pediatric patients below the age of 2 have not been established in PJIA, SJIA or CRS.

Systemic Juvenile Idiopathic Arthritis – Intravenous Use

A multicenter, open-label, single arm study to evaluate the PK, safety and exploratory PD and efficacy of tocilizumab over 12-weeks in SJIA patients (N=11) under 2 years of age was conducted. Patients received intravenous tocilizumab 12 mg/kg every two weeks. Concurrent use of stable background treatment with corticosteroids, MTX, and/or non-steroidal anti-inflammatory drugs was permitted. Patients who completed the 12-week period could continue to the optional extension period (a total of 52-weeks or until the age of 2 years, whichever was longer).

The primary PK endpoints (Cmax, Ctrough and AUC2weeks) of tocilizumab at steady-state in this study were within the ranges of these parameters observed in patients with SJIA aged 2 to 17 years.

The safety and immunogenicity of tocilizumab for patients with SJIA under 2 years of age was assessed descriptively. SAEs, AEs leading to discontinuation, and infectious AEs were reported by 27.3%, 36.4%, and 81.8% of patients. Six patients (54.5%) experienced hypersensitivity reactions, defined as all adverse events occurring during or within 24 hours after an infusion considered related to tocilizumab. Three of these patients experienced serious hypersensitivity reactions and were withdrawn from the study. Three patients with hypersensitivity reactions (two with serious hypersensitivity reactions) developed treatment induced anti- tocilizumab antibodies after the event. There were no cases of MAS based on the protocol-specified criteria, but 2 cases of suspected MAS based on Ravelli criteria [Ravelli A, Minoia F, Davì S on behalf of the Paediatric Rheumatology International Trials Organisation, the Childhood Arthritis and Rheumatology Research Alliance, the Pediatric Rheumatology Collaborative Study Group, and the Histiocyte Society, et al. 2016 Classification Criteria for Macrophage Activation Syndrome Complicating Systemic Juvenile Idiopathic Arthritis. Annals of the Rheumatic Diseases 2016;75:481-489.] .

Cytokine Release Syndrome - Intravenous Use

In the retrospective analysis of pooled outcome data for patients treated with AVTOZMA for CAR T cell-induced CRS, 25 patients were children (2 years up to 12 years of age), and 17 patients were adolescents (12 years up to 18 years of age). There were no differences between the pediatric patients and the adults for safety or efficacy.

8.5 Geriatric Use

Of the 2644 patients who received tocilizumab in Studies I to V [see Clinical Studies (14)], a total of 435 rheumatoid arthritis patients were 65 years of age and older, including 50 patients 75 years and older. Of the 1069 patients who received tocilizumab-SC in studies SC-I and SC-II there were 295 patients 65 years of age and older, including 41 patients 75 years and older. The frequency of serious infection among tocilizumab treated subjects 65 years of age and older was higher than those under the age of 65. As there is a higher incidence of infections in the elderly population in general, caution should be used when treating the elderly.

Clinical studies that included AVTOZMA for CRS did not include sufficient numbers of patients aged 65 and over to determine whether they respond differently from younger patients.

In the EMPACTA, COVACTA, and REMDACTA studies, of the 974 COVID-19 patients in the tocilizumab arm, 375 (39%) were 65 years of age or older. No overall differences in safety or effectiveness of tocilizumab were observed between patients 65 years of age and older and those under the age of 65 years of age in these studies [see Adverse Reactions (6.1) and Clinical Studies (14.10)].

In the RECOVERY study, of the 2022 COVID-19 patients in the tocilizumab arm, 930 (46%) were 65 years of age or older. No overall differences in effectiveness of tocilizumab were observed between patients 65 years of age and older and those under the age 65 years of age in this study [see Clinical Studies (14.10)].

8.6 Hepatic Impairment

The safety and efficacy of tocilizumab products have not been studied in patients with hepatic impairment, including patients with positive HBV and HCV serology [see Warnings and Precautions (5.8)].

8.7 Renal Impairment

No dose adjustment is required in patients with mild or moderate renal impairment. Tocilizumab products have not been studied in patients with severe renal impairment [see Clinical Pharmacology (12.3)].

9 DRUG ABUSE AND DEPENDENCE

No studies on the potential for tocilizumab products to cause dependence have been performed. However, there is no evidence from the available data that tocilizumab products treatment results in dependence.

10 OVERDOSAGE

There are limited data available on overdoses with tocilizumab products. One case of accidental overdose was reported with intravenous tocilizumab in which a patient with multiple myeloma received a dose of 40 mg per kg. No adverse drug reactions were observed. No serious adverse drug reactions were observed in healthy volunteers who received single doses of up to 28 mg per kg, although all 5 patients at the highest dose of 28 mg per kg developed dose-limiting neutropenia.

In case of an overdose, it is recommended that the patient be monitored for signs and symptoms of adverse reactions. Patients who develop adverse reactions should receive appropriate symptomatic treatment.

11 DESCRIPTION

Tocilizumab-anoh is a recombinant humanized anti-human interleukin 6 (IL-6) receptor monoclonal antibody of the immunoglobulin IgG1κ (gamma 1, kappa) subclass with a typical H2L2 polypeptide structure. Each light chain and heavy chain consists of 214 and 448 amino acids, respectively. The four polypeptide chains are linked intra- and inter-molecularly by disulfide bonds. Tocilizumab-anoh has a molecular weight of approximately 148 kDa. The antibody is produced in mammalian (Chinese hamster ovary) cells.

Intravenous Infusion

AVTOZMA (tocilizumab-anoh) injection is a sterile, clear to slightly opalescent, colorless to pale yellow, preservative-free solution for further dilution prior to intravenous infusion with a pH of approximately 6.0. Each single-dose vial, formulated with a histidine and L-histidine hydrochloride monohydrate buffered solution, is available at a concentration of 20 mg/mL containing 80 mg/4 mL, 200 mg/10 mL, or 400 mg/20 mL of AVTOZMA. Each mL of solution contains histidine (0.74 mg), L-histidine hydrochloride monohydrate (1.09 mg), methionine (8.95 mg), polysorbate 80 (0.5 mg), threonine (19.06 mg), and Water for Injection, USP.

Subcutaneous Injection

AVTOZMA (tocilizumab-anoh) injection is a sterile, clear to slightly opalescent, colorless to yellow, preservative-free, histidine buffered solution for subcutaneous use with a pH of approximately 6.0.

It is supplied in a ready-to-use, single-dose 0.9 mL prefilled syringe (PFS) with a needle safety device or a ready- to-use, single-dose 0.9 mL autoinjector that delivers 162 mg tocilizumab-anoh, histidine (0.7 mg), L-histidine hydrochloride monohydrate (1.0 mg), methionine (8.1 mg), polysorbate 80 (0.2 mg), threonine (17.2 mg), and Water for Injection, USP.

12 CLINICAL PHARMACOLOGY

12.1 Mechanism of Action

Tocilizumab products bind to both soluble and membrane-bound IL-6 receptors (sIL-6R and mIL-6R), and have been shown to inhibit IL-6-mediated signaling through these receptors. IL-6 is a pleiotropic pro-inflammatory cytokine produced by a variety of cell types including T- and B-cells, lymphocytes, monocytes and fibroblasts. IL-6 has been shown to be involved in diverse physiological processes such as T-cell activation, induction of immunoglobulin secretion, initiation of hepatic acute phase protein synthesis, and stimulation of hematopoietic precursor cell proliferation and differentiation. IL-6 is also produced by synovial and endothelial cells leading to local production of IL-6 in joints affected by inflammatory processes such as rheumatoid arthritis.

12.2 Pharmacodynamics

In clinical studies in RA patients with the 4 mg per kg and 8 mg per kg intravenous doses or the 162 mg weekly and every other weekly subcutaneous doses of tocilizumab, decreases in levels of C-reactive protein (CRP) to within normal ranges were seen as early as week 2. Changes in pharmacodynamic parameters were observed (i.e., decreases in rheumatoid factor, erythrocyte sedimentation rate (ESR), serum amyloid A, fibrinogen and increases in hemoglobin) with doses, however the greatest improvements were observed with 8 mg per kg tocilizumab. Pharmacodynamic changes were also observed to occur after tocilizumab administration in GCA, PJIA, and SJIA patients (decreases in CRP, ESR, and increases in hemoglobin). The relationship between these pharmacodynamic findings and clinical efficacy is not known.

In healthy subjects administered tocilizumab in doses from 2 to 28 mg per kg intravenously and 81 to 162 mg subcutaneously, absolute neutrophil counts decreased to the nadir 3 to 5 days following tocilizumab administration. Thereafter, neutrophils recovered towards baseline in a dose dependent manner. Rheumatoid arthritis and GCA patients demonstrated a similar pattern of absolute neutrophil counts following tocilizumab administration [see Warnings and Precautions (5.4)].

12.3 Pharmacokinetics

PK of tocilizumab is characterized by nonlinear elimination which is a combination of linear clearance and Michaelis-Menten elimination. The nonlinear part of tocilizumab elimination leads to an increase in exposure that is more than dose-proportional. The pharmacokinetic parameters of tocilizumab do not change with time. Due to the dependence of total clearance on tocilizumab serum concentrations, the half-life of tocilizumab is also concentration-dependent and varies depending on the serum concentration level. Population pharmacokinetic analyses in any patient population tested so far indicate no relationship between apparent clearance and the presence of anti-drug antibodies.

Rheumatoid Arthritis - Intravenous and Subcutaneous Administration

The pharmacokinetics in healthy subjects and RA patients suggest that PK is similar between the two populations.

The population PK model was developed from an analysis dataset composed of an IV dataset of 1793 patients from Study I, Study III, Study IV, and Study V, and from an IV and SC dataset of 1759 patients from Studies SC- I and SC-II. Cmean is included in place of AUCtau, since for dosing regimens with different inter-dose intervals, the mean concentration over the dosing period characterizes the comparative exposure better than AUCtau.

At high serum concentrations, when total clearance of tocilizumab is dominated by linear clearance, a terminal half-life of approximately 21.5 days was derived from the population parameter estimates.

For doses of 4 mg/kg tocilizumab given every 4 weeks intravenously, the estimated median (range) Cmax, Ctrough, and Cmean of tocilizumab at steady state were 86.1 (44.8–202) mcg/mL, 0.1 (0.0–14.6) mcg/mL, and 18.0 (8.9– 50.7) mcg/mL, respectively. For doses of 8 mg/kg tocilizumab given every 4 weeks intravenously, the estimated median (range) Cmax, Ctrough, and Cmean of tocilizumab were 176 (75.4–557) mcg/mL, 13.4 (0.1–154) mcg/mL, and 54.0 (17–260) mcg/mL, respectively. Cmax increased dose-proportionally between doses of 4 and 8 mg/kg IV every 4 weeks, while a greater than dose-proportional increase was observed in Cmean and Ctrough. At steady-state, Cmean and Ctrough were 3.0 and 134 fold higher at 8 mg/kg as compared to 4 mg/kg, respectively.

The accumulation ratios for AUC and Cmax after multiple doses of 4 and 8 mg/kg IV Q4W are low, while the accumulation ratios for Ctrough are higher (2.62 and 2.47, respectively). For Cmax, greater than 90% of the steady- state value was reached after the 1st IV infusion. For AUCtau and Cmean, 90% of the steady-state value was reached after the 1st and 3rd infusion for 4 mg/kg and 8 mg/kg IV, while for Ctrough, approximately 90% of the steady- state value was reached after the 4th IV infusion after both doses.

For doses of 162 mg given every other week subcutaneously, the estimated median (range) steady-state Cmax, Ctrough, and Cmean of tocilizumab were 12.1 (0.4–49.3) mcg/mL, 4.1 (0.0–34.2) mcg/mL, and 9.2 (0.2– 43.6) mcg/mL, respectively.

For doses of 162 mg given every week subcutaneously, the estimated median (range) steady-state Cmax, Ctrough, and Cmean of tocilizumab were 49.8 (3–150) mcg/mL, 42.9 (1.3–144) mcg/mL, and 47.3 (2.4–147) mcg/mL, respectively. Exposures after the 162 mg SC QW regimen were greater by 5.1 (Cmean) to 10.5 fold (Ctrough) compared to the 162 mg SC Q2W regimen.

Accumulation ratios after multiple doses of either SC regimen were higher than after IV regimen with the highest ratios for Ctrough (6.02 and 6.30, for 162 mg SC Q2W and 162 mg SC QW, respectively). The higher accumulation for Ctrough was expected based on the nonlinear clearance contribution at lower concentrations. For Cmax, greater than 90% of the steady-state value was reached after the 5th SC and the 12th SC injection with the Q2W and QW regimens, respectively. For AUCtau and Cmean, 90% of the steady-state value was reached after the 6th and 12th injections for the 162 mg SC Q2W and QW regimens, respectively. For Ctrough, approximately 90% of the steady- state value was reached after the 6th and 12th injections for the 162 mg SC Q2W and QW regimens, respectively.

Population PK analysis identified body weight as a significant covariate impacting the pharmacokinetics of tocilizumab. When given IV on a mg/kg basis, individuals with body weight ≥ 100 kg are predicted to have mean steady-state exposures higher than mean values for the patient population. Therefore, tocilizumab doses exceeding 800 mg per infusion are not recommended in patients with RA [see Dosage and Administration (2.2)]. Due to the flat dosing employed for SC administration of tocilizumab, no modifications are necessary by this dosing route.

Giant Cell Arteritis – Subcutaneous and Intravenous Administration

The pharmacokinetics of tocilizumab SC in GCA patients was determined using a population pharmacokinetic analysis on a dataset composed of 149 GCA patients treated with 162 mg subcutaneously every week or with 162 mg subcutaneously every other week.

For the 162 mg every week dose, the estimated median (range) steady-state Cmax, Ctrough and Cmean of tocilizumab SC were 72.1 (12.2–151) mcg/mL, 67.2 (10.7–145) mcg/mL, and 70.6 (11.7–149) mcg/mL, respectively. The accumulation ratios for Cmean or AUCtau, Ctrough, and Cmax were 10.9, 9.6, and 8.9, respectively. Steady state was reached after 17 weeks. For the 162 mg every other week dose, the estimated median (range) steady-state Cmax, Ctrough, and Cmean of tocilizumab were 17.2 (1.1–56.2) mcg/mL, 7.7 (0.1–37.3) mcg/mL, and 13.7 (0.5– 49) mcg/mL, respectively. The accumulation ratios for Cmean or AUCtau, Ctrough, and Cmax were 2.8, 5.6, and 2.3 respectively. Steady-state was reached after 14 weeks.

The pharmacokinetics of tocilizumab IV in GCA patients was characterized by a non-compartmental pharmacokinetic analysis which included 22 patients treated with 6 mg/kg intravenously every 4 weeks for 20 weeks. The median (range) Cmax, Ctrough and Cmean of tocilizumab at steady state were 178 (115-320) mcg/mL, 22.7 (3.38-54.5) mcg/mL and 57.5 (32.9-110) mcg/mL, respectively. Steady state trough concentrations were within the range observed in GCA patients treated with 162 mg TCZ SC administered every week or every other week.

Based on pharmacokinetic exposure and extrapolation between RA and GCA patients, when given IV on a mg/kg basis, tocilizumab doses exceeding 600 mg per infusion are not recommended in patients with GCA [see Dosage and Administration (2.3)].

Polyarticular Juvenile Idiopathic Arthritis – Intravenous and Subcutaneous Administration

The pharmacokinetics of tocilizumab (TCZ) in PJIA patients was characterized by a population pharmacokinetic analysis which included 188 patients who were treated with TCZ IV or 52 patients treated with TCZ SC.

For doses of 8 mg/kg tocilizumab (patients with a body weight at or above 30 kg) given every 4 weeks intravenously, the estimated median (range) Cmax, Ctrough, and Cmean of tocilizumab at steady state were 181 (114–331) mcg/mL, 3.28 (0.02–35.4) mcg/mL, and 38.6 (22.2–83.8) mcg/mL, respectively. For doses of 10 mg/kg tocilizumab (patients with a body weight less than 30 kg) given every 4 weeks intravenously, the estimated median (range) Cmax, Ctrough, and Cmean of tocilizumab were 167 (125–220) mcg/mL, 0.35 (0– 11.8) mcg/mL, and 30.8 (16.0–48.0) mcg/mL, respectively.

The accumulation ratios were 1.05 and 1.16 for AUC4weeks, and 1.43 and 2.22 for Ctrough for 10 mg/kg (BW less than 30 kg) and 8 mg/kg (BW at or above 30 kg) intravenous doses, respectively. No accumulation for Cmax was observed. Following 10 mg/kg and 8 mg/kg TCZ IV every 4 weeks doses in PJIA patients (aged 2 to 17 years), steady state concentrations (trough and average) were within the range of exposures in adult RA patients following 4 mg/kg and 8 mg/kg every 4 weeks, and steady state peak concentrations in PJIA patients were comparable to those following 8 mg/kg every 4 weeks in adult RA patients.

For doses of 162 mg tocilizumab (patients with a body weight at or above 30 kg) given every 2 weeks subcutaneously, the estimated median (range) Cmax, Ctrough, and Cmean of tocilizumab were 29.7 (7.56– 50.3) mcg/mL, 12.7 (0.19–23.8) mcg/mL, and 23.0 (3.86–36.9) mcg/mL, respectively. For doses of 162 mg tocilizumab (patients with a body weight less than 30 kg) given every 3 weeks subcutaneously, the estimated median (range) Cmax, Ctrough, and Cmean of tocilizumab were 62.4 (39.4–121) mcg/mL, 13.4 (0.21– 52.3) mcg/mL, and 35.7 (17.4–91.8) mcg/mL, respectively.

The accumulation ratios were 1.46 and 2.04 for AUC4weeks, 2.08 and 3.58 for Ctrough, and 1.32 and 1.72 for Cmax, for 162 mg given every 3 weeks (BW less than 30 kg) and 162 mg given every 2 weeks (BW at or above 30 kg) subcutaneous doses, respectively. Following subcutaneous dosing, steady state Ctrough was comparable for patients in the two body weight groups, while steady-state Cmax and Cmean were higher for patients in the less than 30 kg group compared to the group at or above 30 kg. All patients treated with TCZ SC had steady-state Ctrough at or higher than that achieved with TCZ IV across the spectrum of body weights. The average and trough concentrations in patients after subcutaneous dosing were within the range of those achieved in adult patients with RA following the subcutaneous administration of the recommended regimens.

Systemic Juvenile Idiopathic Arthritis – Intravenous and Subcutaneous Administration

The pharmacokinetics of tocilizumab (TCZ) in SJIA patients was characterized by a population pharmacokinetic analysis which included 89 patients who were treated with TCZ IV or 51 patients treated with TCZ SC.

For doses of 8 mg/kg tocilizumab (patients with a body weight at or above 30 kg) given every 2 weeks intravenously, the estimated median (range) Cmax, Ctrough, and Cmean of tocilizumab were 253 (120– 404) mcg/mL, 70.7 (5.26–127) mcg/mL, and 117 (37.6–199) mcg/mL, respectively. For doses of 12 mg/kg tocilizumab (patients with a body weight less than 30 kg) given every 2 weeks intravenously, the estimated median (range) Cmax, Ctrough, and Cmean of tocilizumab were 274 (149–444) mcg/mL, 65.9 (19.0–135) mcg/mL, and 124 (60–194) mcg/mL, respectively.

The accumulation ratios were 1.95 and 2.01 for AUC4weeks, and 3.41 and 3.20 for Ctrough for 12 mg/kg (BW less than 30 kg) and 8 mg/kg (BW at or above 30 kg) intravenous doses, respectively. Accumulation data for Cmax were 1.37 and 1.42 for 12 mg/kg (BW less than 30 kg) and 8 mg/kg (BW at or above 30 kg) intravenous doses, respectively. Following every other week dosing with tocilizumab IV, steady state was reached by 8 weeks for both body weight groups. Mean estimated tocilizumab exposure parameters were similar between the two dose groups defined by body weight.

For doses of 162 mg tocilizumab (patients with a body weight at or above 30 kg) given every week subcutaneously, the estimated median (range) Cmax, Ctrough, and Cmean of tocilizumab were 89.8 (26.4– 190) mcg/mL, 72.4 (19.5–158) mcg/mL, and 82.4 (23.9–169) mcg/mL, respectively. For doses of 162 mg tocilizumab (patients with a body weight less than 30 kg) given every 2 weeks subcutaneously, the estimated median (range) Cmax, Ctrough, and Cmean of tocilizumab were 127 (51.7–266) mcg/mL, 64.2 (16.6–136) mcg/mL, and 92.7 (38.5–199) mcg/mL, respectively.

The accumulation ratios were 2.27 and 4.28 for AUC4weeks, 3.21 and 4.39 for Ctrough, and 1.88 and 3.66 for Cmax, for 162 mg given every 2 weeks (BW less than 30 kg) and 162 mg given every week (BW at or above 30 kg) subcutaneous doses, respectively. Following subcutaneous dosing, steady state was reached by 12 weeks for both body weight groups. All patients treated with tocilizumab SC had steady-state Cmax lower than that achieved with tocilizumab IV across the spectrum of body weights. Trough and mean concentrations in patients after SC dosing were similar to those achieved with tocilizumab IV across body weights.

COVID-19 -Intravenous Administration

The pharmacokinetics of tocilizumab in COVID-19 patients was characterized by a population pharmacokinetic analysis of a dataset composed of 380 adult patients treated with tocilizumab 8mg/kg intravenously (IV) in the COVACTA study [see Clinical Studies (14.10)] and another clinical study.

For one dose of 8 mg/kg tocilizumab IV, the estimated median (range) Cmax and Cday28 of tocilizumab were 151 (77.5-319) mcg/mL and 0.229 (0.00119-19.4) mcg/mL, respectively. For two doses of 8 mg/kg tocilizumab IV separated by at least 8 hours, the estimated median (range) Cmax and Cday28 of tocilizumab was 290 (152-604) mcg/mL and 7.04 (0.00474-54.8) mcg/mL, respectively. The weight-tiered dosing used in RECOVERY study, 800 mg for patients >90 kg, 600 mg for patients >65 and ≤90 kg, 400 mg for patients >40 and ≤65 kg, and 8mg/kg for patients ≤40 kg, is comparable to 8 mg/kg dosing and is expected to have similar exposure.

Absorption

Following subcutaneous dosing, the absorption half-life was around 4 days in RA and GCA patients. The bioavailability for the subcutaneous formulation was 80%.

Following subcutaneous dosing in PJIA patients, the absorption half-life was around 2 days, and the bioavailability for the subcutaneous formulation in PJIA patients was 96%.

Following subcutaneous dosing in SJIA patients, the absorption half-life was around 2 days, and the bioavailability for the SC formulation in SJIA patients was 95%.

In RA patients the median values of Tmax were 2.8 days after the tocilizumab every week dose and 4.7 days after the tocilizumab every other week dose.

In GCA patients, the median values of Tmax were 3 days after the tocilizumab every week dose and 4.5 days after the tocilizumab every other week dose.

Distribution

Following intravenous dosing, tocilizumab undergoes biphasic elimination from the circulation. In rheumatoid arthritis patients the central volume of distribution was 3.5 L and the peripheral volume of distribution was 2.9 L, resulting in a volume of distribution at steady state of 6.4 L.

In GCA patients, the central volume of distribution was 4.09 L, the peripheral volume of distribution was 3.37 L resulting in a volume of distribution at steady state of 7.46 L.

In pediatric patients with PJIA, the central volume of distribution was 1.98 L, the peripheral volume of distribution was 2.1 L, resulting in a volume of distribution at steady state of 4.08 L.

In pediatric patients with SJIA, the central volume of distribution was 1.87 L, the peripheral volume of distribution was 2.14 L resulting in a volume of distribution at steady state of 4.01 L.

In COVID-19 patients treated with one or two infusions of tocilizumab 8 mg/kg intravenously separated by 8 hours, the estimated central volume of distribution was 4.52 L, and the estimated peripheral volume of distribution was 4.23 L, resulting in a volume of distribution of 8.75 L.

Elimination

Tocilizumab is eliminated by a combination of linear clearance and nonlinear elimination. The concentration- dependent nonlinear elimination plays a major role at low tocilizumab concentrations. Once the nonlinear pathway is saturated, at higher tocilizumab concentrations, clearance is mainly determined by the linear clearance. The saturation of the nonlinear elimination leads to an increase in exposure that is more than dose-proportional. The pharmacokinetic parameters of tocilizumab do not change with time.

Population pharmacokinetic analyses in any patient population tested so far indicate no relationship between apparent clearance and the presence of anti-drug antibodies.

The linear clearance in the population pharmacokinetic analysis was estimated to be 12.5 mL per h in RA patients, 6.7 mL per h in GCA patients, 5.8 mL per h in pediatric patients with PJIA, and 5.7 mL per h in pediatric patients with SJIA. In COVID-19 patients, serum concentrations were below the limit of quantification after 35 days on average following one infusion of tocilizumab 8 mg/kg intravenously. The average linear clearance in the population pharmacokinetic analysis was estimated to be 17.6 mL per hour in patients with baseline ordinal scale category 3 (OS 3, patients requiring supplemental oxygen), 22.5 mL per hour in patients with baseline OS 4 (patients requiring high-flow oxygen or non-invasive ventilation), 29 mL per hour in patients with baseline OS 5 (patients requiring mechanical ventilation), and 35.4 mL per hour in patients with baseline OS 6 (patients requiring extracorporeal membrane oxygenation (ECMO) or mechanical ventilation and additional organ support).

Due to the dependence of total clearance on tocilizumab serum concentrations, the half-life of tocilizumab is also concentration-dependent and varies depending on the serum concentration level.

For intravenous administration in RA patients, the concentration-dependent apparent t1/2 is up to 11 days for 4 mg per kg and up to 13 days for 8 mg per kg every 4 weeks in patients with RA at steady-state. For subcutaneous administration in RA patients, the concentration-dependent apparent t1/2 is up to 13 days for 162 mg every week and 5 days for 162 mg every other week in patients with RA at steady-state.

In GCA patients at steady state, the effective t1/2 of tocilizumab varied between 18.3 and 18.9 days for 162 mg subcutaneously every week dosing regimen and between 4.2 and 7.9 days for 162 mg subcutaneously every other week dosing regimen. For intravenous administration in GCA patients, the TCZ concentration-dependent apparent t1/2 was 13.2 days following 6 mg/kg every 4 weeks.

The t1/2 of tocilizumab in children with PJIA is up to 17 days for the two body weight categories (8 mg/kg for body weight at or above 30 kg or 10 mg/kg for body weight below 30 kg) during a dosing interval at steady state. For subcutaneous administration, the t1/2 of tocilizumab in PJIA patients is up to 10 days for the two body weight categories (every other week regimen for body weight at or above 30 kg or every 3 week regimen for body weight less than 30 kg) during a dosing interval at steady state.

The t1/2 of tocilizumab intravenous in pediatric patients with SJIA is up to 16 days for the two body weight categories (8 mg/kg for body weight at or above 30 kg and 12 mg/kg for body weight below 30 kg every other week) during a dosing interval at steady-state. Following subcutaneous administration, the effective t1/2 of tocilizumab subcutaneous in SJIA patients is up to 14 days for both the body weight categories (162 mg every week for body weight at or above 30 kg and 162 mg every two weeks for body weight below 30 kg) during a dosing interval at steady state.

Specific Populations

Population pharmacokinetic analyses in adult rheumatoid arthritis patients and GCA patients showed that age, gender and race did not affect the pharmacokinetics of tocilizumab. Linear clearance was found to increase with body size. In RA patients, the body weight-based dose (8 mg per kg) resulted in approximately 86% higher exposure in patients who are greater than 100 kg in comparison to patients who are less than 60 kg. There was an inverse relationship between tocilizumab exposure and body weight for flat dose subcutaneous regimens.

In GCA patients treated with tocilizumab-SC, higher exposure was observed in patients with lower body weight. For the 162 mg every week subcutaneous dosing regimen, the steady-state Cmean was 51% higher in patients with body weight less than 60 kg compared to patients weighing between 60 to 100 kg. For the 162 mg every other week subcutaneous regimen, the steady-state Cmean was 129% higher in patients with body weight less than 60 kg compared to patients weighing between 60 to 100 kg. There is limited data for patients above 100 kg (n=7).

In COVID-19 patients, exposure following body-weight-based intravenous dosing (8 mg per kg tocilizumab up to 100 kg body weight with a maximum dose of 800 mg) was dependent on body weight and disease severity assessed by an ordinal scale (OS). Within an OS category, compared to patients with a mean body weight of 80 kg, exposure was 20% lower in patients weighing less than 60 kg. Exposure in patients weighing more than 100 kg was in the same range as exposure in patients with a mean body weight of 80 kg. For an 80 kg patient, exposure decreases as OS category increases; for each category increase, exposure decreases by 13%.

Patients with Hepatic Impairment

No formal study of the effect of hepatic impairment on the pharmacokinetics of tocilizumab was conducted.

Patients with Renal Impairment

No formal study of the effect of renal impairment on the pharmacokinetics of tocilizumab was conducted.

Most of the RA and GCA patients in the population pharmacokinetic analysis had normal renal function or mild renal impairment. Mild renal impairment (estimated creatinine clearance less than 80 mL per min and at or above 50 mL per min based on Cockcroft-Gault formula) did not impact the pharmacokinetics of tocilizumab.

Approximately one-third of the patients in the tocilizumab-SC GCA clinical trial had moderate renal impairment at baseline (estimated creatinine clearance of 30-59 mL/min). No impact on tocilizumab exposure was noted in these patients.

No dose adjustment is required in patients with mild or moderate renal impairment.

Drug Interaction Studies

In vitro data suggested that IL-6 reduced mRNA expression for several CYP450 isoenzymes including CYP1A2, CYP2B6, CYP2C9, CYP2C19, CYP2D6 and CYP3A4, and this reduced expression was reversed by co-incubation with tocilizumab at clinically relevant concentrations. Accordingly, inhibition of IL-6 signaling in RA patients treated with tocilizumab may restore CYP450 activities to higher levels than those in the absence of tocilizumab leading to increased metabolism of drugs that are CYP450 substrates. Its effect on CYP2C8 or transporters (e.g., P-gp) is unknown. This is clinically relevant for CYP450 substrates with a narrow therapeutic index, where the dose is individually adjusted. Upon initiation of AVTOZMA, in patients being treated with these types of medicinal products, therapeutic monitoring of the effect (e.g., warfarin) or drug concentration (e.g., cyclosporine or theophylline) should be performed and the individual dose of the medicinal product adjusted as needed. Caution should be exercised when AVTOZMA is coadministered with drugs where decrease in effectiveness is undesirable, e.g., oral contraceptives (CYP3A4 substrates) [see Drug Interactions (7.2)].

Simvastatin

Simvastatin is a CYP3A4 and OATP1B1 substrate. In 12 RA patients not treated with tocilizumab, receiving 40 mg simvastatin, exposures of simvastatin and its metabolite, simvastatin acid, was 4- to 10-fold and 2-fold higher, respectively, than the exposures observed in healthy subjects. One week following administration of a single infusion of tocilizumab (10 mg per kg), exposure of simvastatin and simvastatin acid decreased by 57% and 39%, respectively, to exposures that were similar or slightly higher than those observed in healthy subjects. Exposures of simvastatin and simvastatin acid increased upon withdrawal of tocilizumab in RA patients. Selection of a particular dose of simvastatin in RA patients should take into account the potentially lower exposures that may result after initiation of AVTOZMA (due to normalization of CYP3A4) or higher exposures after discontinuation of AVTOZMA.

Omeprazole

Omeprazole is a CYP2C19 and CYP3A4 substrate. In RA patients receiving 10 mg omeprazole, exposure to omeprazole was approximately 2 fold higher than that observed in healthy subjects. In RA patients receiving 10 mg omeprazole, before and one week after tocilizumab infusion (8 mg per kg), the omeprazole AUCinf decreased by 12% for poor (N=5) and intermediate metabolizers (N=5) and by 28% for extensive metabolizers (N=8) and were slightly higher than those observed in healthy subjects.

Dextromethorphan

Dextromethorphan is a CYP2D6 and CYP3A4 substrate. In 13 RA patients receiving 30 mg dextromethorphan, exposure to dextromethorphan was comparable to that in healthy subjects. However, exposure to its metabolite, dextrorphan (a CYP3A4 substrate), was a fraction of that observed in healthy subjects. One week following administration of a single infusion of tocilizumab (8 mg per kg), dextromethorphan exposure was decreased by approximately 5%. However, a larger decrease (29%) in dextrorphan levels was noted after tocilizumab infusion.

13 NONCLINICAL TOXICOLOGY

13.1 Carcinogenesis, Mutagenesis, Impairment of Fertility

No long-term animal studies have been performed to establish the carcinogenicity potential of tocilizumab products. Literature indicates that the IL-6 pathway can mediate anti-tumor responses by promoting increased immune cell surveillance of the tumor microenvironment. However, available published evidence also supports that IL-6 signaling through the IL-6 receptor may be involved in pathways that lead to tumorigenesis. The malignancy risk in humans from an antibody that disrupts signaling through the IL-6 receptor, such as tocilizumab, is presently unknown.

Fertility and reproductive performance were unaffected in male and female mice that received a murine analogue of tocilizumab administered by the intravenous route at a dose of 50 mg/kg every three days.

14 CLINICAL STUDIES

14.1 Rheumatoid Arthritis – Intravenous Administration

The efficacy and safety of intravenously administered tocilizumab was assessed in five randomized, double-blind, multicenter studies in patients greater than 18 years with active rheumatoid arthritis diagnosed according to American College of Rheumatology (ACR) criteria. Patients had at least 8 tender and 6 swollen joints at baseline. Tocilizumab was given intravenously every 4 weeks as monotherapy (Study I), in combination with methotrexate (MTX) (Studies II and III) or other disease-modifying anti-rheumatic drugs (DMARDs) (Study IV) in patients with an inadequate response to those drugs, or in combination with MTX in patients with an inadequate response to TNF antagonists (Study V).

Study I (NCT00109408) evaluated patients with moderate to severe active rheumatoid arthritis who had not been treated with MTX within 24 weeks prior to randomization, or who had not discontinued previous methotrexate treatment as a result of clinically important toxic effects or lack of response. In this study, 67% of patients were MTX-naïve, and over 40% of patients had rheumatoid arthritis less than 2 years. Patients received tocilizumab 8 mg per kg monotherapy or MTX alone (dose titrated over 8 weeks from 7.5 mg to a maximum of 20 mg weekly). The primary endpoint was the proportion of tocilizumab patients who achieved an ACR 20 response at Week 24.

Study II (NCT00106535) was a 104-week study with an optional 156-week extension phase that evaluated patients with moderate to severe active rheumatoid arthritis who had an inadequate clinical response to MTX. Patients received tocilizumab 8 mg per kg, tocilizumab 4 mg per kg, or placebo every four weeks, in combination with MTX (10 to 25 mg weekly). Upon completion of 52-weeks, patients received open-label treatment with tocilizumab 8 mg per kg through 104 weeks or they had the option to continue their double-blind treatment if they maintained a greater than 70% improvement in swollen/tender joint count. Two pre-specified interim analyses at week 24 and week 52 were conducted. The primary endpoint at week 24 was the proportion of patients who achieved an ACR 20 response. At weeks 52 and 104, the primary endpoints were change from baseline in modified total Sharp-Genant score and the area under the curve (AUC) of the change from baseline in HAQ-DI score.

Study III (NCT00106548) evaluated patients with moderate to severe active rheumatoid arthritis who had an inadequate clinical response to MTX. Patients received tocilizumab 8 mg per kg, tocilizumab 4 mg per kg, or placebo every four weeks, in combination with MTX (10 to 25 mg weekly). The primary endpoint was the proportion of patients who achieved an ACR 20 response at week 24.

Study IV (NCT00106574) evaluated patients who had an inadequate response to their existing therapy, including one or more DMARDs. Patients received tocilizumab 8 mg per kg or placebo every four weeks, in combination with the stable DMARDs. The primary endpoint was the proportion of patients who achieved an ACR 20 response at week 24.

Study V (NCT00106522) evaluated patients with moderate to severe active rheumatoid arthritis who had an inadequate clinical response or were intolerant to one or more TNF antagonist therapies. The TNF antagonist therapy was discontinued prior to randomization. Patients received tocilizumab 8 mg per kg, tocilizumab 4 mg per kg, or placebo every four weeks, in combination with MTX (10 to 25 mg weekly). The primary endpoint was the proportion of patients who achieved an ACR 20 response at week 24.

Clinical Response

The percentages of intravenous tocilizumab-treated patients achieving ACR 20, 50 and 70 responses are shown in Table 4. In all intravenous studies, patients treated with 8 mg per kg tocilizumab had higher ACR 20, ACR 50, and ACR 70 response rates versus MTX- or placebo-treated patients at week 24.

During the 24 week controlled portions of Studies I to V, patients treated with tocilizumab at a dose of 4 mg per kg in patients with inadequate response to DMARDs or TNF antagonist therapy had lower response rates compared to patients treated with tocilizumab 8 mg per kg.

Table 4 Clinical Response at Weeks 24 and 52 in Active and Placebo Controlled Trials of Intravenous Tocilizumab (Percent of Patients)
Percent of Patients
Response Rate | Study I |  | Study II |  |  | Study III |  |  | Study IV |  | Study V
Response Rate | MTX | Tocilizumab 8 mg per kg | Placebo + MTX | Tocilizumab 4 mg per kg + MTX | Tocilizumab 8 mg per kg + MTX | Placebo + MTX | Tocilizumab 4 mg per kg + MTX | Tocilizumab 8 mg per kg + MTX | Placebo + DMARDs | Tocilizumab 8 mg per kg + DMARDs | Placebo + MTX | Tocilizumab 4 mg per kg + MTX | Tocilizumab 8 mg per kg + MTX
Response Rate | N=284 | N=286 (95% CI) | N=393 | N=399 (95% CI [CI: 95% confidence interval of the weighted difference to placebo adjusted for site (and disease duration for Study I only)]) | N=398 (95% CI) | N=204 | N=213 (95% CI) | N=205 (95% CI) | N=413 | N=803 (95% CI) | N=158 | N=161 (95% CI) | N=170 (95% CI)
ACR 20
Week 24 | 53% | 70% (0.11, 0.27) | 27% | 51% (0.17, 0.29) | 56% (0.23, 0.35) | 27% | 48% (0.15, 0.32) | 59% (0.23, 0.41) | 24% | 61% (0.30, 0.40) | 10% | 30% (0.15, 0.36) | 50% (0.36, 0.56)
Week 52 | N/A | N/A | 25% | 47% (0.15, 0.28) | 56% (0.25, 0.38) | N/A | N/A | N/A | N/A | N/A | N/A | N/A | N/A
ACR 50
Week 24 | 34% | 44% (0.04, 0.20) | 10% | 25% (0.09, 0.20) | 32% (0.16, 0.28) | 11% | 32% (0.13, 0.29) | 44% (0.25, 0.41) | 9% | 38% (0.23, 0.33) | 4% | 17% (0.05, 0.25) | 29% (0.21, 0.41)
Week 52 | N/A | N/A | 10% | 29% (0.14, 0.25) | 36% (0.21, 0.32) | N/A | N/A | N/A | N/A | N/A | N/A | N/A | N/A
ACR 70
Week 24 | 15% | 28% (0.07, 0.22) | 2% | 11% (0.03, 0.13) | 13% (0.05, 0.15) | 2% | 12% (0.04, 0.18) | 22% (0.12, 0.27) | 3% | 21% (0.13, 0.21) | 1% | 5% (-0.06, 0.14) | 12% (0.03, 0.22)
Week 52 | N/A | N/A | 4% | 16% (0.08, 0.17) | 20% (0.12, 0.21) | N/A | N/A | N/A | N/A | N/A | N/A | N/A | N/A
Major Clinical Responses [Major clinical response is defined as achieving an ACR 70 response for a continuous 24 week periodHealth Assessment Questionnaire: 0 = best, 3 = worst; 20 questions; 8 categories: dressing and grooming, arising, eating, walking, hygiene, reach, grip, and activitiesThe same patients may not have responded at each timepoint.sThe same patients may not have responded at each timepoint.Major clinical response is defined as achieving an ACR 70 response for a continuous 24 week periodHealth Assessment Questionnaire: 0 = best, 3 = worst; 20 questions; 8 categories: dressing and grooming, arising, eating, walking, hygiene, reach, grip, and activitiesThe same patients may not have responded at each timepoint.]
Week 52 | N/A | N/A | 1% | 4% (0.01, 0.06) | 7% (0.03, 0.09) | N/A | N/A | N/A | N/A | N/A | N/A | N/A | N/A

In study II, a greater proportion of patients treated with 4 mg per kg and 8 mg per kg tocilizumab + MTX achieved a low level of disease activity as measured by a DAS 28-ESR less than 2.6 compared with placebo +MTX treated patients at week 52. The proportion of tocilizumab-treated patients achieving DAS 28-ESR less than 2.6, and the number of residual active joints in these responders in Study II are shown in Table 5.

Table 5 Proportion of Patients with DAS28-ESR Less Than 2.6 with Number of Residual Active Joints in Trials of Intravenous Tocilizumab
Study II
 | Placebo + MTX N = 393 | Tocilizumab 4 mg per kg + MTX N = 399 | Tocilizumab 8 mg per kg + MTX N = 398
DAS28-ESR less than 2.6
Proportion of responders at week 52 (n) 95% confidence interval | 3% (12) | 18% (70) 0.10, 0.19 | 32% (127) 0.24, 0.34
Of responders, proportion with 0 active joints (n) | 33% (4) | 27% (19) | 21% (27)
Of responders, proportion with 1 active joint (n) | 8% (1) | 19% (13) | 13% (16)
Of responders, proportion with 2 active joints (n) | 25% (3) | 13% (9) | 20% (25)
Of responders, proportion with 3 or more active joints (n) | 33% (4) | 41% (29) | 47% (59)
*n denotes numerator of all the percentage. Denominator is the intent-to-treat population. Not all patients received DAS28 assessments at Week 52.

The results of the components of the ACR response criteria for Studies III and V are shown in Table 6. Similar results to Study III were observed in Studies I, II and IV.

Table 6 Components of ACR Response at Week 24 in Trials of Intravenous Tocilizumab
 | Study III |  |  |  |  |  | Study V
 | Tocilizumab 4 mg per kg + MTX |  | Tocilizumab 8 mg per kg + MTX |  | Placebo + MTX |  | Tocilizumab 4 mg per kg + MTX |  | Tocilizumab 8 mg per kg + MTX |  | Placebo + MTX
 | N=213 |  | N=205 |  | N=204 |  | N=161 |  | N=170 |  | N=158
Component (mean) | Baseline | Week 24 [Data shown is mean at week 24, difference in adjusted mean change from baseline compared with placebo + MTX at week 24 and 95% confidence interval for that difference] | Baseline | Week 24 | Baseline | Week 24 | Baseline | Week 24 | Baseline | Week 24 | Baseline | Week 24
Number of tender joints (0-68) | 33 | 19 -7.0 (-10.0, -4.1) | 32 | 14.5 -9.6 (-12.6, -6.7) | 33 | 25 | 31 | 21 -10.8 (-14.6, -7.1) | 32 | 17 -15.1 (-18.8, -11.4) | 30 | 30
Number of swollen joints (0-66) | 20 | 10 -4.2 (-6.1, -2.3) | 19.5 | 8 -6.2 (-8.1, -4.2) | 21 | 15 | 19.5 | 13 -6.2 (-9.0, -3.5) | 19 | 11 -7.2 (-9.9, -4.5) | 19 | 18
Pain [Visual analog scale: 0 = best, 100 = worst] | 61 | 33 -11.0 (-17.0, -5.0) | 60 | 30 -15.8 (-21.7, -9.9) | 57 | 43 | 63.5 | 43 -12.4 (-22.1, -2.1) | 65 | 33 -23.9 (-33.7, -14.1) | 64 | 48
Patient global assessment | 66 | 34 -10.9 (-17.1, -4.8) | 65 | 31 -14.9 (-20.9, -8.9) | 64 | 45 | 70 | 46 -10.0 (-20.3, 0.3) | 70 | 36 -17.4 (-27.8, -7.0) | 71 | 51
Physician global assessment | 64 | 26 -5.6 (-10.5, -0.8) | 64 | 23 -9.0 (-13.8, -4.2) | 64 | 32 | 66.5 | 39 -10.5 (-18.6, -2.5) | 66 | 28 -18.2 (-26.3, -10.0) | 67.5 | 43
Disability index (HAQ) [Major clinical response is defined as achieving an ACR 70 response for a continuous 24 week periodHealth Assessment Questionnaire: 0 = best, 3 = worst; 20 questions; 8 categories: dressing and grooming, arising, eating, walking, hygiene, reach, grip, and activitiesThe same patients may not have responded at each timepoint.sThe same patients may not have responded at each timepoint.Major clinical response is defined as achieving an ACR 70 response for a continuous 24 week periodHealth Assessment Questionnaire: 0 = best, 3 = worst; 20 questions; 8 categories: dressing and grooming, arising, eating, walking, hygiene, reach, grip, and activitiesThe same patients may not have responded at each timepoint.] | 1.64 | 1.01 -0.18 (-0.34, -0.02) | 1.55 | 0.96 -0.21 (-0.37, -0.05) | 1.55 | 1.21 | 1.67 | 1.39 -0.25 (-0.42, -0.09) | 1.75 | 1.34 -0.34 (-0.51, -0.17) | 1.70 | 1.58
CRP (mg per dL) | 2.79 | 1.17 -1.30 (-2.0, -0.59) | 2.61 | 0.25 -2.156 (-2.86, -1.46) | 2.36 | 1.89 | 3.11 | 1.77 -1.34 (-2.5, -0.15) | 2.80 | 0.28 -2.52 (-3.72, -1.32) | 3.705 | 3.06

The percent of ACR 20 responders by visit for Study III is shown in Figure 1. Similar response curves were observed in studies I, II, IV, and V.

Figure 1 Percent of ACR 20 Responders by Visit for Study III (Inadequate Response to MTX) [Major clinical response is defined as achieving an ACR 70 response for a continuous 24 week periodHealth Assessment Questionnaire: 0 = best, 3 = worst; 20 questions; 8 categories: dressing and grooming, arising, eating, walking, hygiene, reach, grip, and activitiesThe same patients may not have responded at each timepoint.sThe same patients may not have responded at each timepoint.Major clinical response is defined as achieving an ACR 70 response for a continuous 24 week periodHealth Assessment Questionnaire: 0 = best, 3 = worst; 20 questions; 8 categories: dressing and grooming, arising, eating, walking, hygiene, reach, grip, and activitiesThe same patients may not have responded at each timepoint.]

Radiographic Response

In Study II, structural joint damage was assessed radiographically and expressed as change in total Sharp-Genant score and its components, the erosion score and joint space narrowing score. Radiographs of hands/wrists and forefeet were obtained at baseline, 24 weeks, 52 weeks, and 104 weeks and scored by readers unaware of treatments group and visit number. The results from baseline to week 52 are shown in Table 7. Tocilizumab 4 mg per kg slowed (less than 75% inhibition compared to the control group) and tocilizumab 8 mg per kg inhibited (at least 75% inhibition compared to the control group) the progression of structural damage compared to placebo plus MTX at week 52.

Table 7 Mean Radiographic Change from Baseline to Week 52 in Study II
 | Placebo + MTX | Tocilizumab 4 mg per kg + MTX | Tocilizumab 8 mg per kg + MTX
 | N=294 | N=343 | N=353
Week 52 [Week 52 analysis employs linearly extrapolated data for patients after escape, withdrawal, or loss to follow up.]
Total Sharp-Genant Score, Mean (SD) | 1.17 (3.14) | 0.33 (1.30) | 0.25 (0.98)
Adjusted Mean difference [Difference between the adjusted means (tocilizumab + MTX - Placebo + MTX)] (95%CI) |  | -0.83 (-1.13, -0.52) | -0.90 (-1.20, -0.59)
Erosion Score, Mean (SD) | 0.76 (2.14) | 0.20 (0.83) | 0.15 (0.77)
Adjusted Mean difference (95%CI) |  | -0.55 (-0.76, -0.34) | -0.60 (-0.80, -0.39)
Joint Space Narrowing Score, Mean (SD) | 0.41 (1.71) | 0.13 (0.72) | 0.10 (0.49)
Adjusted Mean difference (95%CI) |  | -0.28 (-0.44, -0.11) | -0.30 (-0.46, -0.14)
SD = standard deviation

The mean change from baseline to week 104 in Total Sharp-Genant Score for the tocilizumab 4 mg per kg groups was 0.47 (SD = 1.47) and for the 8 mg per kg groups was 0.34 (SD = 1.24). By the week 104, most patients in the control (placebo + MTX) group had crossed over to active treatment, and results are therefore not included for comparison. Patients in the active groups may have crossed over to the alternate active dose group, and results are reported per original randomized dose group.

In the placebo group, 66% of patients experienced no radiographic progression (Total Sharp-Genant Score change ≤ 0) at week 52 compared to 78% and 83% in the tocilizumab 4 mg per kg and 8 mg per kg, respectively. Following 104 weeks of treatment, 75% and 83% of patients initially randomized to tocilizumab 4 mg per kg and 8 mg per kg, respectively, experienced no progression of structural damage compared to 66% of placebo treated patients.

Health Related Outcomes

In Study II, physical function and disability were assessed using the Health Assessment Questionnaire Disability Index (HAQ-DI). Both dosing groups of tocilizumab demonstrated a greater improvement compared to the placebo group in the AUC of change from baseline in the HAQ-DI through week 52. The mean change from baseline to week 52 in HAQ-DI was 0.6, 0.5, and 0.4 for tocilizumab 8 mg per kg, tocilizumab 4 mg per kg, and placebo treatment groups, respectively. Sixty-three percent (63%) and sixty percent (60%) of patients in the tocilizumab 8 mg per kg and tocilizumab 4 mg per kg treatment groups, respectively, achieved a clinically relevant improvement in HAQ-DI (change from baseline of ≥ 0.3 units) at week 52 compared to 53% in the placebo treatment group.

Other Health-Related Outcomes

General health status was assessed by the Short Form Health Survey (SF-36) in Studies I – V. Patients receiving tocilizumab demonstrated greater improvement from baseline compared to placebo in the Physical Component Summary (PCS), Mental Component Summary (MCS), and in all 8 domains of the SF-36.

Cardiovascular Outcomes

Study WA25204 (NCT01331837) was a randomized, open-label (sponsor-blinded), 2-arm parallel-group, multicenter, non-inferiority, cardiovascular (CV) outcomes trial in patients with a diagnosis of moderate to severe RA. This CV safety study was designed to exclude a moderate increase in CV risk in patients treated with tocilizumab compared with a TNF inhibitor standard of care (etanercept).

The study included 3,080 seropositive RA patients with active disease and an inadequate response to non- biologic disease-modifying anti-rheumatic drugs, who were aged ≥50 years with at least one additional CV risk factor beyond RA. Patients were randomized 1:1 to IV tocilizumab 8 mg/kg Q4W or SC etanercept 50 mg QW and followed for an average of 3.2 years. The primary endpoint was the comparison of the time-to-first occurrence of any component of a composite of major adverse CV events (MACE; non-fatal myocardial infarction, non-fatal stroke, or CV death), with the final intent-to-treat analysis based on a total of 161 confirmed CV events (83/1538 [5.4%] for tocilizumab; 78/1542 [5.1%] for etanercept) reviewed by an independent and blinded adjudication committee.

Non-inferiority of tocilizumab to etanercept for cardiovascular risk was determined by excluding >80% relative increase in the risk of MACE. The estimated hazard ratio (HR) for the risk of MACE comparing tocilizumab to etanercept was 1.05; 95% CI (0.77, 1.43).

14.2 Rheumatoid Arthritis – Subcutaneous Administration

The efficacy and safety of subcutaneously administered tocilizumab was assessed in two double-blind, controlled, multicenter studies in patients with active RA. One study, SC-I (NCT01194414), was a non-inferiority study that compared the efficacy and safety of tocilizumab 162 mg administered every week subcutaneously to 8 mg per kg intravenously every four weeks. The second study, SC-II (NCT01232569), was a placebo controlled superiority study that evaluated the safety and efficacy of tocilizumab 162 mg administered every other week subcutaneously to placebo. Both SC-I and SC-II required patients to be >18 years of age with moderate to severe active rheumatoid arthritis diagnosed according to ACR criteria who had at least 4 tender and 4 swollen joints at baseline (SC-I) or at least 8 tender and 6 swollen joints at baseline (SC-II), and an inadequate response to their existing DMARD therapy, where approximately 20% also had a history of inadequate response to at least one TNF inhibitor. All patients in both SC studies received background non-biologic DMARD(s).

In SC-I, 1262 patients were randomized 1:1 to receive tocilizumab-SC 162 mg every week or intravenous tocilizumab 8 mg/kg every four weeks in combination with DMARD(s). In SC-II, 656 patients were randomized 2:1 to tocilizumab-SC 162 mg every other week or placebo, in combination with DMARD(s). The primary endpoint in both studies was the proportion of patients who achieved an ACR20 response at Week 24.

The clinical response to 24 weeks of tocilizumab-SC therapy is shown in Table 8. In SC-I, the primary outcome measure was ACR20 at Week 24. The pre-specified non-inferiority margin was a treatment difference of 12%. The study demonstrated non-inferiority of tocilizumab with respect to ACR20 at Week 24; ACR50, ACR70, and DAS28 responses are also shown in Table 8. In SC-II, a greater portion of patients treated with tocilizumab 162 mg subcutaneously every other week achieved ACR20, ACR50, and ACR70 responses compared to placebo-treated patients (Table 8). Further, a greater proportion of patients treated with tocilizumab 162 mg subcutaneously every other week achieved a low level of disease activity as measured by a DAS28-ESR less than 2.6 at Week 24 compared to those treated with placebo (Table 8).

Table 8 Clinical Response at Week 24 in Trials of Subcutaneous Tocilizumab (Percent of Patients)
 | SC-I [Per Protocol Population] |  | SC-II [Intent To Treat Population]
 | TCZ SC 162 mg every week + DMARD | TCZ IV 8mg/kg + DMARD | TCZ SC 162 mg every other week + DMARD | Placebo + DMARD
 | N=558 | N=537 | N=437 | N=219
ACR20
Week 24 | 69% | 73.4% | 61% | 32%
Weighted difference (95% CI) | -4% (-9.2, 1.2) | 30% (22.0, 37.0)
ACR50
Week 24 | 47% | 49% | 40% | 12%
Weighted difference (95% CI) | -2% (-7.5, 4.0) | 28% (21.5, 34.4)
ACR70
Week 24 | 24% | 28% | 20% | 5%
Weighted difference (95% CI) | -4% (-9.0, 1.3) | 15% (9.8, 19.9)
Change in DAS28 [Adjusted mean]
Week 24 | -3.5 | -3.5 | -3.1 | -1.7
Adjusted mean difference (95% CI) | 0 (-0.2, 0.1) | -1.4 (-1.7, -1.1)
DAS28 < 2.6
Week 24 | 38.4% | 36.9% | 32.0% | 4.0%
Weighted difference (95% CI) | 0.9 (-5.0, 6.8) | 28.6 (22.0, 35.2)
TCZ = tocilizumab

The results of the components of the ACR response criteria and the percent of ACR20 responders by visit for tocilizumab-SC in Studies SC-I and SC-II were consistent with those observed for tocilizumab-IV.

Radiographic Response

In study SC-II, the progression of structural joint damage was assessed radiographically and expressed as a change from baseline in the van der Heijde modified total Sharp score (mTSS). At week 24, significantly less radiographic progression was observed in patients receiving tocilizumab-SC every other week plus DMARD(s) compared to placebo plus DMARD(s); mean change from baseline in mTSS of 0.62 vs. 1.23, respectively, with an adjusted mean difference of -0.60 (-1.1, -0.1). These results are consistent with those observed in patients treated with intravenous tocilizumab.

Health Related Outcomes

In studies SC-I and SC-II, the mean decrease from baseline to week 24 in HAQ-DI was 0.6, 0.6, 0.4 and 0.3, and the proportion of patients who achieved a clinically relevant improvement in HAQ-DI (change from baseline of ≥ 0.3 units) was 65%, 67%, 58% and 47%, for the subcutaneous every week, intravenous 8 mg/kg, subcutaneous every other week, and placebo treatment groups, respectively.

Other Health-Related Outcomes

General health status was assessed by the SF-36 in Studies SC-I and SC-II. In Study SC-II, patients receiving tocilizumab every other week demonstrated greater improvement from baseline compared to placebo in the PCS, MCS, and in all 8 domains of the SF-36. In Study SC-I, improvements in these scores were similar between tocilizumab-SC every week and tocilizumab-IV 8 mg/kg.

14.3 Giant Cell Arteritis – Subcutaneous Administration

The efficacy and safety of subcutaneously administered tocilizumab was assessed in a single, randomized, double-blind, multicenter study in patients with active GCA. In Study WA28119 (NCT01791153), 251 screened patients with new-onset or relapsing GCA were randomized to one of four treatment arms. Two subcutaneous doses of tocilizumab (162 mg every week and 162 mg every other week) were compared to two different placebo control groups (pre-specified prednisone-taper regimen over 26 weeks and 52 weeks) randomized 2:1:1:1. The study consisted of a 52-week blinded period, followed by a 104-week open-label extension.

All patients received background glucocorticoid (prednisone) therapy. Each of the tocilizumab-treated groups and one of the placebo-treated groups followed a pre-specified prednisone-taper regimen with the aim to reach 0 mg by 26 weeks, while the second placebo-treated group followed a pre-specified prednisone-taper regimen with the aim to reach 0 mg by 52 weeks designed to be more in keeping with standard practice.

The primary efficacy endpoint was the proportion of patients achieving sustained remission from Week 12 through Week 52. Sustained remission was defined by a patient attaining a sustained (1) absence of GCA signs and symptoms from Week 12 through Week 52, (2) normalization of erythrocyte sedimentation rate (ESR) (to < 30 mm/hr without an elevation to ≥ 30 mm/hr attributable to GCA) from Week 12 through Week 52, (3) normalization of C-reactive protein (CRP) (to < 1 mg/dL, with an absence of successive elevations to ≥ 1mg/dL) from Week 12 through Week 52, and (4) successful adherence to the prednisone taper defined by not more than 100 mg of excess prednisone from Week 12 through Week 52. Tocilizumab 162 mg weekly and 162 mg every other week + 26 weeks prednisone taper both showed superiority in achieving sustained remission from Week 12 through Week 52 compared with placebo + 26 weeks prednisone taper (Table 9). Both tocilizumab treatment arms also showed superiority compared to the placebo + 52 weeks prednisone taper (Table 9).

Table 9 Efficacy Results from Study WA28119
 | PBO + 26 weeks prednisone taper N=50 | PBO + 52 weeks prednisone taper N=51 | TCZ 162mg SC QW + 26 weeks prednisone taper N=100 | TCZ 162 mg SC Q2W + 26 weeks prednisone taper N=49
Sustained remission [Sustained remission was achieved by a patient meeting all of the following components: absence of GCA signs and symptomsb, normalization of ESRc, normalization of CRPd and adherence to the prednisone taper regimene]
Responders, n (%) | 7 (14.0%) | 9 (17.6%) | 56 (56.0%) | 26 (53.1%)
Unadjusted difference in proportions vs PBO + 26 weeks taper (99.5% CI) | N/A | N/A | 42.0% (18.0, 66.0) | 39.1% (12.5, 65.7)
Unadjusted difference in proportions vs PBO + 52 weeks taper (99.5% CI) | N/A | N/A | 38.4% (14.4, 62.3) | 35.4% (8.6, 62.2)
Components of Sustained Remission
Sustained absence of GCA signs and symptoms [Patients who did not have any signs or symptoms of GCA recorded from Week 12 up to Week 52.] , n (%) | 20 (40.0%) | 23 (45.1%) | 69 (69.0%) | 28 (57.1%)
Sustained ESR<30 mm/hr [Patients who did not have an elevated ESR ≥30 mm/hr which was classified as attributed to GCA from Week 12 up to Week 52.] , n (%) | 20 (40.0%) | 22 (43.1%) | 83 (83.0%) | 37 (75.5%)
Sustained CRP normalization [Patients who did not have two or more consecutive CRP records of ≥ 1mg/dL from Week 12 up to Week 52.] , n (%) | 17 (34.0%) | 13 (25.5%) | 72 (72.0%) | 34 (69.4%)
Successful prednisone tapering [Patients who did not enter escape therapy and received ≤ 100mg of additional concomitant prednisone from Week 12 up to Week 52.] , n (%) | 10 (20.0%) | 20 (39.2%) | 60 (60.0%) | 28 (57.1%)
Patients not completing the study to week 52 were classified as non-responders in the primary and key secondary analysis: PBO+26: 6 (12.0%), PBO+52: 5 (9.8%), TCZ QW: 15 (15.0%), TCZ Q2W: 9 (18.4%).
CRP = C-reactive protein
ESR = erythrocyte sedimentation rate
PBO = placebo
Q2W = every other week dose
QW = every week dose
TCZ = tocilizumab

The estimated annual cumulative prednisone dose was lower in the two tocilizumab dose groups (medians of 1887 mg and 2207 mg on tocilizumab QW and Q2W, respectively) relative to the placebo arms (medians of 3804 mg and 3902 mg on placebo + 26 weeks prednisone and placebo + 52 weeks prednisone taper, respectively).

14.4 Giant Cell Arteritis – Intravenous Administration

Intravenously administered tocilizumab in patients with GCA was assessed in WP41152 (NCT03923738), an open-label PK-PD and safety study to determine the appropriate intravenous dose of tocilizumab that achieved comparable PK-PD profiles to the tocilizumab-SC regimen.

At enrollment, all patients (n=24) were in remission on tocilizumab-IV. In Period 1, all patients received open- label tocilizumab-IV 7 mg/kg every 4 weeks for 20 weeks. Patients who completed Period 1 and remained in remission (n=22) were eligible to enter Period 2, and received open-label tocilizumab-IV 6 mg/kg every 4 weeks for 20 weeks.

The efficacy of intravenous tocilizumab 6 mg/kg in adult patients with GCA is based on pharmacokinetic exposure and extrapolation to the efficacy established for subcutaneous tocilizumab in patients with GCA [see Clinical Pharmacology (12.3) and Clinical Studies (14.3)].

14.5 Polyarticular Juvenile Idiopathic Arthritis – Intravenous Administration

The efficacy of tocilizumab was assessed in a three-part study, WA19977 (NCT00988221), including an open- label extension in children 2 to 17 years of age with active polyarticular juvenile idiopathic arthritis (PJIA), who had an inadequate response to methotrexate or inability to tolerate methotrexate. Patients had at least 6 months of active disease (mean disease duration of 4.2 ± 3.7 years), with at least five joints with active arthritis (swollen or limitation of movement accompanied by pain and/or tenderness) and/or at least 3 active joints having limitation of motion (mean, 20 ± 14 active joints). The patients treated had subtypes of JIA that at disease onset included Rheumatoid Factor Positive or Negative Polyarticular JIA, or Extended Oligoarticular JIA. Treatment with a stable dose of methotrexate was permitted but was not required during the study. Concurrent use of disease modifying antirheumatic drugs (DMARDs), other than methotrexate, or other biologics (e.g., TNF antagonists or T cell costimulation modulator) were not permitted in the study.

Part I consisted of a 16-week active tocilizumab treatment lead-in period (n=188) followed by Part II, a 24-week randomized double-blind placebo-controlled withdrawal period, followed by Part III, a 64-week open-label period. Eligible patients weighing at or above 30 kg received tocilizumab at 8 mg/kg intravenously once every four weeks. Patients weighing less than 30 kg were randomized 1:1 to receive either tocilizumab 8 mg/kg or 10 mg/kg intravenously every four weeks. At the conclusion of the open-label Part I, 91% of patients taking background MTX in addition to tocilizumab and 83% of patients on tocilizumab monotherapy achieved an ACR 30 response at week 16 compared to baseline and entered the blinded withdrawal period (Part II) of the study. The proportions of patients with JIA ACR 50/70 responses in Part I were 84.0%, and 64%, respectively for patients taking background MTX in addition to tocilizumab and 80% and 55% respectively for patients on tocilizumab monotherapy.

In Part II, patients (ITT, n=163) were randomized to tocilizumab (same dose received in Part I) or placebo in a 1:1 ratio that was stratified by concurrent methotrexate use and concurrent corticosteroid use. Each patient continued in Part II of the study until Week 40 or until the patient satisfied JIA ACR 30 flare criteria (relative to Week 16) and qualified for escape.

The primary endpoint was the proportion of patients with a JIA ACR 30 flare at week 40 relative to week 16. JIA ACR 30 flare was defined as 3 or more of the 6 core outcome variables worsening by at least 30% with no more than 1 of the remaining variables improving by more than 30% relative to Week 16.

Tocilizumab treated patients experienced significantly fewer disease flares compared to placebo-treated patients (26% [21/82] versus 48% [39/81]; adjusted difference in proportions -21%, 95% CI: -35%, -8%).

During the withdrawal phase (Part II), more patients treated with tocilizumab showed JIA ACR 30/50/70 responses at Week 40 compared to patients withdrawn to placebo.

14.6 Polyarticular Juvenile Idiopathic Arthritis – Subcutaneous Administration

Subcutaneously administered tocilizumab in pediatric patients with polyarticular juvenile idiopathic arthritis (PJIA) was assessed in WA28117 (NCT01904279), a 52-week, open-label, multicenter, PK-PD and safety study to determine the appropriate subcutaneous dose of tocilizumab that achieved comparable PK/PD profiles to the tocilizumab-IV regimen. PJIA patients aged 1 to 17 years with an inadequate response or inability to tolerate MTX, including patients with well-controlled disease on treatment with tocilizumab-IV and tocilizumab-naïve patients with active disease, were treated with subcutaneous tocilizumab based on body weight.

Patients weighing at or above 30 kg (n = 25) were treated with 162 mg of tocilizumab-SC every 2 weeks and patients weighing less than 30 kg (n = 27) received 162 mg of tocilizumab-SC every 3 weeks for 52 weeks. Of these 52 patients, 37 (71%) were naive to tocilizumab and 15 (29%) had been receiving tocilizumab-IV and switched to tocilizumab-SC at baseline.

The efficacy of subcutaneous tocilizumab in children 2 to 17 years of age is based on pharmacokinetic exposure and extrapolation of the established efficacy of intravenous tocilizumab in polyarticular JIA patients and subcutaneous tocilizumab in patients with RA [see Clinical Pharmacology (12.3) and Clinical Studies (14.2 and 14.5)].

14.7 Systemic Juvenile Idiopathic Arthritis – Intravenous Administration

The efficacy of tocilizumab for the treatment of active SJIA was assessed in WA18221 (NCT00642460), a 12- week randomized, double blind, placebo-controlled, parallel group, 2-arm study. Patients treated with or without MTX, were randomized (tocilizumab:placebo = 2:1) to one of two treatment groups: 75 patients received tocilizumab infusions every two weeks at either 8 mg per kg for patients at or above 30 kg or 12 mg per kg for patients less than 30 kg and 37 were randomized to receive placebo infusions every two weeks. Corticosteroid tapering could occur from week six for patients who achieved a JIA ACR 70 response. After 12 weeks or at the time of escape, due to disease worsening, patients were treated with tocilizumab in the open-label extension phase at weight appropriate dosing.

The primary endpoint was the proportion of patients with at least 30% improvement in JIA ACR core set (JIA ACR 30 response) at Week 12 and absence of fever (no temperature at or above 37.5°C in the preceding 7 days). JIA ACR (American College of Rheumatology) responses are defined as the percentage improvement (e.g., 30%, 50%, 70%) in 3 of any 6 core outcome variables compared to baseline, with worsening in no more than 1 of the remaining variables by 30% or more. Core outcome variables consist of physician global assessment, parent per patient global assessment, number of joints with active arthritis, number of joints with limitation of movement, erythrocyte sedimentation rate (ESR), and functional ability (childhood health assessment questionnaire-CHAQ).

Primary endpoint result and JIA ACR response rates at Week 12 are shown in Table 10.

Table 10 Efficacy Findings at Week 12
 | Tocilizumab N=75 | Placebo N=37
Primary Endpoint: JIA ACR 30 response + absence of fever
Responders | 85% | 24%
Weighted difference (95% CI) | 62 (45, 78) | -
JIA ACR Response Rates at Week 12
JIA ACR 30
Responders | 91% | 24%
Weighted difference [The weighted difference is the difference between the tocilizumab and Placebo response rates, adjusted for the stratification factors (weight, disease duration, background oral corticosteroid dose and background methotrexate use).] | 67 | -
(95% CI) [CI: confidence interval of the weighted difference.] | (51, 83)
JIA ACR 50
Responders | 85% | 11%
Weighted difference | 74 | -
(95% CI) | (58, 90)
JIA ACR 70
Responders | 71% | 8%
Weighted difference | 63 | -
(95% CI) | (46, 80)

The treatment effect of tocilizumab was consistent across all components of the JIA ACR response core variables. JIA ACR scores and absence of fever responses in the open label extension were consistent with the controlled portion of the study (data available through 44 weeks).

Systemic Features

Of patients with fever or rash at baseline, those treated with tocilizumab had fewer systemic features; 35 out of 41 (85%) became fever free (no temperature recording at or above 37.5°C in the preceding 14 days) compared to 5 out of 24 (21%) of placebo-treated patients, and 14 out of 22 (64%) became free of rash compared to 2 out of 18 (11%) of placebo-treated patients. Responses were consistent in the open label extension (data available through 44 weeks).

Corticosteroid Tapering

Of the patients receiving oral corticosteroids at baseline, 8 out of 31 (26%) placebo and 48 out of 70 (69%), tocilizumab patients achieved a JIA ACR 70 response at week 6 or 8 enabling corticosteroid dose reduction. Seventeen (24%) tocilizumab patients versus 1 (3%) placebo patient were able to reduce the dose of corticosteroid by at least 20% without experiencing a subsequent JIA ACR 30 flare or occurrence of systemic symptoms to week 12. In the open label portion of the study, by week 44, there were 44 out of 103 (43%) tocilizumab patients off oral corticosteroids. Of these 44 patients 50% were off corticosteroids 18 weeks or more.

Health Related Outcomes

Physical function and disability were assessed using the Childhood Health Assessment Questionnaire Disability Index (CHAQ-DI). Seventy-seven percent (58 out of 75) of patients in the tocilizumab treatment group achieved a minimal clinically important improvement in CHAQ-DI (change from baseline of ≥ 0.13 units) at week 12 compared to 19% (7 out of 37) in the placebo treatment group.

14.8 Systemic Juvenile Idiopathic Arthritis – Subcutaneous Administration

Subcutaneously administered tocilizumab in pediatric patients with systemic juvenile idiopathic arthritis (SJIA) was assessed in WA28118 (NCT01904292), a 52-week, open-label, multicenter, PK-PD and safety study to determine the appropriate subcutaneous dose of tocilizumab that achieved comparable PK/PD profiles to the tocilizumab-IV regimen.

Eligible patients received tocilizumab subcutaneously dosed according to body weight, with patients weighing at or above 30 kg (n = 26) dosed with 162 mg of tocilizumab every week and patients weighing below 30 kg (n = 25) dosed with 162 mg of tocilizumab every 10 days (n=8) or every 2 weeks (n=17) for 52 weeks. Of these 51 patients, 26 (51%) were naive to subcutaneous tocilizumab and 25 (49%) had been receiving tocilizumab intravenously and switched to subcutaneous tocilizumab at baseline.

The efficacy of subcutaneous tocilizumab in children 2 to 17 years of age is based on pharmacokinetic exposure and extrapolation of the established efficacy of intravenous tocilizumab in systemic JIA patients [see Clinical Pharmacology (12.3) and Clinical Studies (14.7)].

14.9 Cytokine Release Syndrome - Intravenous Administration

The efficacy of tocilizumab for the treatment of CRS was assessed in a retrospective analysis of pooled outcome data from clinical trials of CAR T-cell therapies for hematological malignancies. Evaluable patients had been treated with tocilizumab 8 mg/kg (12 mg/kg for patients < 30 kg) with or without additional high-dose corticosteroids for severe or life-threatening CRS; only the first episode of CRS was included in the analysis. The study population included 24 males and 21 females (total 45 patients) of median age 12 years (range, 3–23 years); 82% were Caucasian. The median time from start of CRS to first dose of tocilizumab was 4 days (range, 0-18 days). Resolution of CRS was defined as lack of fever and off vasopressors for at least 24 hours. Patients were considered responders if CRS resolved within 14 days of the first dose of tocilizumab, if no more than 2 doses of tocilizumab were needed, and if no drugs other than tocilizumab and corticosteroids were used for treatment. Thirty-one patients (69%; 95% CI: 53%–82%) achieved a response. Achievement of resolution of CRS within 14 days was confirmed in a second study using an independent cohort that included 15 patients (range: 9–75 years old) with CAR T cell-induced CRS.

14.10 COVID-19 – Intravenous Administration

The efficacy of tocilizumab for the treatment of COVID-19 was based on RECOVERY (NCT04381936), a randomized, controlled, open-label, platform study, and supported by the results from EMPACTA (NCT04372186), a randomized, double-blind, placebo-controlled study. Results of two other randomized, double-blind, placebo-controlled studies, COVACTA (NCT04320615) and REMDACTA (NCT04409262) which evaluated the efficacy of tocilizumab for the treatment of COVID-19 are also summarized.

RECOVERY (Randomised Evaluation of COVID-19 Therapy) Collaborative Group Study in Hospitalized Adults Diagnosed with COVID-19

RECOVERY was a randomized, controlled, open-label, multicenter platform study conducted in the United Kingdom to evaluate the efficacy and safety of potential treatments in hospitalized adult patients with severe COVID-19 pneumonia. Eligible patients for the tocilizumab portion of the study had clinically suspected or laboratory-confirmed SARS-CoV-2 infection and no medical contraindications to any of the treatments and had clinical evidence of progressive COVID-19 (defined as oxygen saturation <92% on room air or receiving oxygen therapy, and CRP ≥75 mg/L). Patients were then randomized to receive either standard of care (SoC) or intravenous tocilizumab at a weight-tiered dosing comparable to the recommended dosage [see Clinical Pharmacology (12.3)] in addition to SoC.

Efficacy analyses were performed in the intent-to-treat (ITT) population comprising 4116 adult patients who were randomized to the tocilizumab + SoC arm (n=2022) or to the SoC arm (n=2094). The mean age of participants was 64 years (range: 20 to 101), and patients were 67% male, 76% White, 11% Asian, 3% Black or African American, and 1% mixed race. At baseline, 0.2% of patients were not on supplemental oxygen, 45% of patients required low flow oxygen, 41% of patients required non-invasive ventilation or high-flow oxygen, and 14% of patients required invasive mechanical ventilation; 82% of patients were reported to be receiving systemic corticosteroids.

The primary efficacy endpoint was time to death through Day 28. The results for the overall population and the subgroups of patients who were or were not receiving systemic corticosteroids at time of randomization are summarized in Table 11.

Table 11 Mortality through Day 28 in RECOVERY
 | Tocilizumab+ SoC N=2022 n (%) [P-value reflects that the RECOVERY trial primary analysis results were statistically significant at the two-sided significance level of α = 0.05.] | SoC N=2094 n (%) | Hazard Ratio (95% CI) | Risk Difference (95% CI)
Mortality | 621 (30.7%) | 729 (34.9%) | 0.85 (0.76, 0.94) p= 0.0028 | -4.1% (-7.0, -1.3)
By baseline receipt of corticosteroid use
Mortality for patients receiving systemic corticosteroids at randomization [Probabilities of dying by Day 28 were estimated by the Kaplan-Meier method.] | 482/1664 (29.0%) | 600/1721 (34.9%) | 0.79 (0.70, 0.89) | -5.9% (-9.1, -2.8)
Mortality for patients not receiving systemic corticosteroids at randomization | 139/357 (39.0%) | 127/367 (34.6%) | 1.16 (0.91, 1.48) | 4.4% (-2.6, 11.5)

EMPACTA

EMPACTA was a randomized, double-blind, placebo-controlled, multicenter study to evaluate intravenous tocilizumab 8 mg/kg in combination with SoC in hospitalized, non-ventilated adult patients with COVID-19 pneumonia. Eligible patients were at least 18 years of age, had confirmed SARS-CoV-2 infection by a positive reverse-transcriptase polymerase chain reaction (RT-PCR) result, had pneumonia confirmed by radiography, and had SpO2 < 94% on ambient air.

Of the 389 patients randomized, efficacy analyses were performed in the modified intent-to-treat (mITT) population comprising 377 patients who were randomized and received study medication (249 in the tocilizumab arm; 128 in the placebo arm). The mean age of participants was 56 years (range: 20 to 95); 59% of patients were male, 56% were of Hispanic or Latino ethnicity, 53% were White, 20% were American Indian/Alaska Native, 15% were Black/African American and 2% were Asian. At baseline, 9% patients were not on supplemental oxygen, 64% patients required low flow oxygen, 27% patients required high-flow oxygen, and 73% were on corticosteroids.

The primary efficacy endpoint evaluated time to progression to mechanical ventilation or death through Day 28. The hazard ratio comparing tocilizumab to placebo was 0.56 (95% CI, 0.33 to 0.97), a statistically significant result (log-rank, p-value = 0.036). The cumulative proportion of patients who required mechanical ventilation or died by Day 28 was 12.0% (95% CI, 8.5% to 16.9%) in the tocilizumab arm and 19.3% (95% CI, 13.3% to 27.4%) in the placebo arm.

Mortality at Day 28 was 10.4% in the tocilizumab arm versus 8.6% in the placebo arm (weighted difference (tocilizumab arm - placebo arm): 2.0% [95% CI, -5.2% to 7.8%]).

COVACTA

COVACTA was a randomized, double-blind, placebo-controlled, multicenter study to evaluate intravenous tocilizumab 8 mg/kg in combination with SoC for the treatment of adult patients hospitalized with severe COVID- 19 pneumonia. The study randomized 452 patients who were at least 18 years of age with confirmed SARS-CoV- 2 infection by a positive RT-PCR result, had pneumonia confirmed by radiography, and had oxygen saturation of 93% or lower on ambient air or a ratio of arterial oxygen partial pressure to fractional inspired oxygen of 300 mmHg or less. At baseline, 3% of patients were not on supplemental oxygen, 28% were on low flow oxygen, 30% were on non-invasive ventilation or high flow oxygen, 38% were on invasive mechanical ventilation, and 22% were on corticosteroids. The primary efficacy endpoint was clinical status on Day 28 assessed on a 7-category ordinal scale that ranged from "discharged" to "death." There were no statistically significant differences observed in the distributions of clinical status on the 7-category ordinal scale at Day 28 when comparing the tocilizumab arm to the placebo arm.

Mortality at Day 28 was 19.7% in the tocilizumab arm versus 19.4% in the placebo arm (weighted difference (tocilizumab arm - placebo arm): 0.3% [95% CI, -7.6 to 8.2]).

REMDACTA

REMDACTA was a randomized, double-blind, placebo-controlled, multicenter study to evaluate intravenous tocilizumab 8 mg/kg in combination with intravenous remdesivir (RDV) 200 mg on Day 1 followed by 100 mg once daily for a total of 10 days in hospitalized patients with severe COVID-19 pneumonia. The study randomized 649 adult patients with SARS-CoV-2 infection confirmed by a positive polymerase chain reaction (PCR) result, pneumonia confirmed by radiography, and who required supplemental oxygen > 6 L/min to maintain SpO2 >93%. At baseline, 7% of patients were on low flow oxygen, 80% were on non-invasive ventilation or high flow oxygen, 14% were on invasive mechanical ventilation, and 84% were on corticosteroids.

The primary efficacy endpoint was time from randomization to hospital discharge or 'ready for discharge' up to Day 28. There was no statistically significant difference between the treatment arms with respect to time to hospital discharge or "ready for discharge" through Day 28.

Mortality at Day 28 was 18.1% in the tocilizumab + RDV arm versus 19.5% in the placebo +RDV arm (weighted difference (tocilizumab arm - placebo arm): -1.3% [95% CI, -7.8% to 5.2%]).

Mortality Across Studies in Patients Receiving Baseline Corticosteroids

A study-level meta-analysis was conducted on EMPACTA, COVACTA, REMDACTA and RECOVERY studies. For each of the four studies, the risk difference through Day 28 was estimated by the Kaplan-Meier method in the subgroup of patients receiving baseline corticosteroids, summarized in Figure 2. Patients from the RECOVERY trial represent 78.8% of the total sample size in this meta-analysis. The combined risk difference showed that tocilizumab treatment (n=2261) resulted in a 4.61% absolute reduction in the risk of death at Day 28 (risk difference=-4.6%; 95% CI: -7.3% to -1.9%) compared to SoC (n=2034).

Figure 2 Risk Differences Through Day 28 for Baseline Corticosteroid Use Subpopulation in RECOVERY, EMPACTA, COVACTA and REMDACTA studies

16 HOW SUPPLIED/STORAGE AND HANDLING

For Intravenous Infusion

AVTOZMA (tocilizumab-anoh) injection is a preservative-free, sterile clear to slightly opalescent, colorless to pale yellow solution for intravenous infusion supplied in a single-dose vial packaged within cartons in the following strengths and packaging configurations:

- 80 mg/ 4 mL (20 mg/mL): carton of one vial (NDC 72606-042-01); carton of 4 vials (NDC 72606-042-02).
- 200 mg/ 10 mL (20 mg/mL): carton of one vial (NDC 72606-043-01); carton of 4 vials (NDC 72606-043-02).
- 400 mg/ 20 mL (20 mg/mL): carton of one vial (NDC 72606-044-01); carton of 4 vials (NDC 72606-044-02).

For Subcutaneous Injection

AVTOZMA (tocilizumab-anoh) injection is supplied as a preservative-free, sterile, clear to slightly opalescent, colorless to yellow solution for subcutaneous administration. The following packaging configurations are available:

- Each single-dose prefilled syringe delivers 162 mg/0.9 mL: carton of one syringe (NDC 72606-045-01); carton of 4 syringes (NDC 72606-045-02); carton of 3 packs of 4 syringes (NDC 72606-045-03). The syringe plunger stopper and needle cover are not made with natural rubber latex.
- Each single-dose prefilled autoinjector 162 mg/0.9 mL: carton of one syringe (NDC 72606-045-04); carton of 4 syringes (NDC 72606-045-05); carton of 3 packs of 4 syringes (NDC 72606-045-06). The syringe plunger stopper and needle cover are not made with natural rubber latex.

Storage and Handling: Do not use beyond expiration date on the container, package, prefilled syringe, or autoinjector. AVTOZMA must be refrigerated at 36°F to 46°F (2ºC to 8ºC). Do not freeze. Protect the vials, syringes, and autoinjectors from light by storage in the original carton until time of use, and keep syringes and autoinjectors dry. Once removed from the refrigerator, the prefilled syringe and autoinjector can be stored at room temperature at or below 77°F (25°C) for up to 3 weeks. The prefilled syringe and autoinjector must always be kept in the carton.

17 PATIENT COUNSELING INFORMATION

Advise the patient to read the FDA-approved patient labeling (Medication Guide and Instructions for Use).

Serious Infections

Inform patients that AVTOZMA may lower their resistance to infections [see Warnings and Precautions (5.1)]. Instruct the patient of the importance of contacting their doctor immediately when symptoms suggesting infection appear in order to assure rapid evaluation and appropriate treatment.

Gastrointestinal Perforation

Inform patients that some patients who have been treated with AVTOZMA have had serious side effects in the stomach and intestines [see Warnings and Precautions (5.2)]. Instruct the patient of the importance of contacting their doctor immediately when symptoms of fever, severe, persistent abdominal pain, and change in bowel habits appear to assure rapid evaluation and appropriate treatment.

Hypersensitivity and Serious Allergic Reactions

Inform patients that some patients who have been treated with AVTOZMA have developed serious allergic reactions, including anaphylaxis, as well as serious skin reactions [see Warnings and Precautions (5.6)]. Advise patients to stop taking AVTOZMA and seek immediate medical attention if they experience any symptom of serious allergic reactions (including rash, hives, and swelling of the face, lips, tongue, and throat that may cause difficulty in breathing or swallowing).

Instruction on Injection Technique

Assess patient suitability for home use for subcutaneous injection. Perform the first injection under the supervision of a qualified healthcare professional. If a patient or caregiver is to administer subcutaneous AVTOZMA, instruct him/her in injection techniques and assess his/her ability to inject subcutaneously to ensure proper administration of subcutaneous AVTOZMA and the suitability for home use [see Instructions for Use].

Prior to use, remove the prefilled syringe (PFS) or autoinjector from the refrigerator and allow to sit at room temperature outside of the carton for 30 minutes (PFS) or 45 minutes (autoinjector), out of the reach of children. Do not warm AVTOZMA in any other way.

Advise patients to consult their healthcare provider if the full dose is not received.

A puncture-resistant container for disposal of needles, syringes and autoinjectors should be used and should be kept out of the reach of children. Instruct patients or caregivers in the technique as well as proper needle, syringe and autoinjector disposal, and caution against reuse of these items.

Pregnancy

Inform female patients of reproductive potential that AVTOZMA may cause fetal harm and to inform their prescriber of a known or suspected pregnancy [see Use in Specific Populations (8.1)].

AVTOZMA®
(tocilizumab-anoh)

Manufactured by:
CELLTRION, Inc.
23, Academy-ro, Yeonsu-gu,
Incheon, 22014, Republic of Korea
US License Number 1996

Distributed by:
CELLTRION USA, Inc.
One Evertrust Plaza Suite 1207
Jersey City, NJ 07302

Medication Guide
AVTOZMA® (AV-TOZE'-MAH)
(tocilizumab-anoh) injection
for intravenous use
AVTOZMA® (AV-TOZE'-MAH)
(tocilizumab-anoh) injection
for subcutaneous use

What is the most important information I should know about AVTOZMA?

AVTOZMA can cause serious side effects including:

1. Serious Infections. AVTOZMA is a medicine that affects your immune system. AVTOZMA can lower the ability of your immune system to fight infections. Some people have serious infections while taking AVTOZMA, including tuberculosis (TB), and infections caused by bacteria, fungi, or viruses that can spread throughout the body. Some people have died from these infections. Your healthcare provider should assess you for TB before starting AVTOZMA (except if you have COVID-19).

If you have COVID-19, your healthcare provider should monitor you for signs and symptoms of new infections during and after treatment with AVTOZMA.

Your healthcare provider should monitor you closely for signs and symptoms of TB during and after treatment with AVTOZMA.

- You should not start taking AVTOZMA if you have any kind of infection unless your healthcare provider says it is okay.

Before starting AVTOZMA, tell your healthcare provider if you:

- think you have an infection or have symptoms of an infection, with or without a fever, such as:

- sweating or chills
- shortness of breath
- warm, red, or painful skin or sores on your body

- feel very tired
- muscle aches
- blood in phlegm
- diarrhea or stomach pain

- cough
- weight loss
- burning when you urinate or urinating more often than normal

- are being treated for an infection.
- get a lot of infections or have infections that keep coming back.
- have diabetes, HIV, or a weak immune system. People with these conditions have a higher chance for infections.
- have TB, or have been in close contact with someone with TB.
- live or have lived, or have traveled to certain parts of the country (such as the Ohio and Mississippi River valleys and the Southwest) where there is an increased chance for getting certain kinds of fungal infections (histoplasmosis, coccidiomycosis, or blastomycosis). These infections may happen or become more severe if you use AVTOZMA. Ask your healthcare provider if you do not know if you have lived in an area where these infections are common.
- have or have had hepatitis B.

After starting AVTOZMA, call your healthcare provider right away if you have any symptoms of an infection. AVTOZMA can make you more likely to get infections or make worse any infection that you have.

2. Tears (perforation) of the stomach or intestines.
  - Tell your healthcare provider if you have had diverticulitis (inflammation in parts of the large intestine) or ulcers in your stomach or intestines. Some people taking AVTOZMA get tears in their stomach or intestine. This happens most often in people who also take nonsteroidal anti-inflammatory drugs (NSAIDs), corticosteroids, or methotrexate.
  - Tell your healthcare provider right away if you have fever and new onset stomach-area pain that does not go away, and a change in your bowel habits.
3. Liver problems (Hepatotoxicity): Some people have experienced serious life-threatening liver problems, which required a liver transplant or led to death. Your healthcare provider may tell you to stop taking AVTOZMA if you develop new or worse liver problems during treatment with AVTOZMA. Tell your healthcare provider right away if you have any of the following symptoms:

- feeling tired (fatigue)
- lack of appetite for several days or longer (anorexia)
- yellowing of your skin or the whites of your eyes (jaundice)
- abdominal swelling and pain on the right side of your stomach-area
- light colored stools

- weakness
- nausea and vomiting
- confusion
- dark "tea-colored" urine

4. Changes in certain laboratory test results. Your healthcare provider should do blood tests before you start receiving AVTOZMA. If you have rheumatoid arthritis (RA) or giant cell arteritis (GCA) your healthcare provider should do blood tests every 4 to 8 weeks after you start receiving AVTOZMA for the first 6 months and then every 3 months after that. If you have polyarticular juvenile idiopathic arthritis (PJIA) you will have blood tests done every 4 to 8 weeks during treatment. If you have systemic juvenile idiopathic arthritis (SJIA) you will have blood tests done every 2 to 4 weeks during treatment. These blood tests are to check for the following side effects of AVTOZMA:
  - low neutrophil count. Neutrophils are white blood cells that help the body fight off bacterial infections.
  - low platelet count. Platelets are blood cells that help with blood clotting and stop bleeding.
  - increase in certain liver function tests.
  - increase in blood cholesterol levels. You may also have changes in other laboratory tests, such as your blood cholesterol levels. Your healthcare provider should do blood tests to check your cholesterol levels 4 to 8 weeks after you start receiving AVTOZMA.
  Your healthcare provider will determine how often you will have follow-up blood tests. Make sure you get all your follow-up blood tests done as ordered by your healthcare provider.
  You should not receive AVTOZMA if your neutrophil or platelet counts are too low or your liver function tests are too high.
  Your healthcare provider may stop your AVTOZMA treatment for a period of time or change your dose of medicine if needed because of changes in these blood test results.
5. Cancer. AVTOZMA may increase your risk of certain cancers by changing the way your immune system works. Tell your healthcare provider if you have ever had any type of cancer.

See "What are the possible side effects with AVTOZMA?" for more information about side effects.

What is AVTOZMA?

AVTOZMA is a prescription medicine called an Interleukin-6 (IL-6) receptor antagonist. AVTOZMA is used:

- To treat adults with moderately to severely active rheumatoid arthritis (RA), after at least one other medicine called a Disease-Modifying Anti-Rheumatic Drug (DMARD) has been used and did not work well.
- To treat adults with giant cell arteritis (GCA).
- To treat people with active PJIA ages 2 and above.
- To treat people with active SJIA ages 2 and above.
- To treat hospitalized adults with coronavirus disease 2019 (COVID-19) receiving systemic corticosteroids and requiring supplemental oxygen or mechanical ventilation.
- AVTOZMA is not approved for subcutaneous use in people with COVID-19.

It is not known if AVTOZMA is safe and effective in children with PJIA or SJIA under 2 years of age or in children with conditions other than PJIA or SJIA.

Do not take AVTOZMA: if you are allergic to tocilizumab products, or any of the ingredients in AVTOZMA. See the end of this Medication Guide for a complete list of ingredients in AVTOZMA.

Before you receive AVTOZMA, tell your healthcare provider about all of your medical conditions, including if you:

- have an infection. See "What is the most important information I should know about AVTOZMA?"
- have liver problems.
- have any stomach-area (abdominal) pain or been diagnosed with diverticulitis or ulcers in your stomach or intestines.
- have had a reaction to tocilizumab products or any of the ingredients in AVTOZMA before.
- have or had a condition that affects your nervous system, such as multiple sclerosis.
- have recently received or are scheduled to receive a vaccine:
  - All vaccines should be brought up-to-date before starting AVTOZMA, unless urgent treatment initiation is required.
  - People who take AVTOZMA should not receive live vaccines.
  - People taking AVTOZMA can receive non-live vaccines.
- plan to have surgery or a medical procedure.
- are pregnant or plan to become pregnant. AVTOZMA may harm your unborn baby. Tell your healthcare provider if you become pregnant or think you may be pregnant during treatment with AVTOZMA.
- are breastfeeding or plan to breastfeed. It is not known if AVTOZMA passes into your breast milk. Talk to your healthcare provider about the best way to feed your baby if you take AVTOZMA.

Tell your healthcare provider about all of the medicines you take, including prescription, over-the-counter medicines, vitamins and herbal supplements. AVTOZMA and other medicines may affect each other causing side effects.

Especially tell your healthcare provider if you take:

- any other medicines to treat your RA. Taking AVTOZMA with these medicines may increase your risk of infection.
- medicines that affect the way certain liver enzymes work. Ask your healthcare provider if you are not sure if your medicine is one of these.

Know the medicines you take. Keep a list of them to show to your healthcare provider and pharmacist when you get a new medicine.

How will I receive AVTOZMA?

Into a vein (IV or intravenous infusion) for Rheumatoid Arthritis, Giant Cell Arteritis, PJIA, SJIA or COVID- 19:

- If your healthcare provider prescribes AVTOZMA as an IV infusion, you will receive AVTOZMA from a healthcare provider through a needle placed in a vein in your arm. The infusion will take about 1 hour to give you the full dose of medicine.
- For rheumatoid arthritis, giant cell arteritis or PJIA you will receive a dose of AVTOZMA about every 4 weeks.
- For SJIA you will receive a dose of AVTOZMA about every 2 weeks.
- For COVID-19, you will receive a single dose of AVTOZMA, and if needed one additional dose.
- While taking AVTOZMA, you may continue to use other medicines that help treat your rheumatoid arthritis, PJIA, SJIA or COVID-19 such as methotrexate, non-steroidal anti-inflammatory drugs (NSAIDs) and prescription steroids, as instructed by your healthcare provider.
- Keep all of your follow-up appointments and get your blood tests as ordered by your healthcare provider.

Under the skin (SC or subcutaneous injection) for Rheumatoid Arthritis, Giant Cell Arteritis, PJIA or SJIA:

- See the Instructions for Use at the end of this Medication Guide for instructions about the right way to prepare and give your AVTOZMA injections at home.
- AVTOZMA is available as a single-dose Prefilled Syringe or single-dose Prefilled Autoinjector.
- You may also receive AVTOZMA as an injection under your skin (subcutaneous). If your healthcare provider decides that you or a caregiver can give your injections of AVTOZMA at home, you or your caregiver should receive training on the right way to prepare and inject AVTOZMA. Do not try to inject AVTOZMA until you have been shown the right way to give the injections by your healthcare provider.
- For PJIA or SJIA, you may self-inject with the Prefilled Syringe or Prefilled Autoinjector, or your caregiver can give you AVTOZMA, if both your healthcare provider and parent/legal guardian find it appropriate.
- Your healthcare provider will tell you how much AVTOZMA to use and when to use it.

What are the possible side effects with AVTOZMA?

AVTOZMA can cause serious side effects, including:

- See "What is the most important information I should know about AVTOZMA?"
- Hepatitis B infection in people who carry the virus in their blood. If you are a carrier of the hepatitis B virus (a virus that affects the liver), the virus may become active while you use AVTOZMA. Your healthcare provider may do blood tests before you start treatment with AVTOZMA and while you are using AVTOZMA. Tell your healthcare provider if you have any of the following symptoms of a possible hepatitis B infection:

- feel very tired
- vomiting
- chills
- dark urine

- skin or eyes look yellow
- clay-colored bowel movements
- stomach discomfort
- skin rash

- little or no appetite
- fevers
- muscle aches

- Serious Allergic Reactions. Serious allergic reactions, including death, can happen with AVTOZMA. These reactions can happen with any infusion or injection of AVTOZMA, even if they did not occur with an earlier infusion or injection. Stop taking AVTOZMA, contact your healthcare provider, and get emergency help right away if you have any of the following signs of a serious allergic reaction:
  - swelling of your face, lips, mouth, or tongue
  - trouble breathing
  - wheezing
  - severe itching
  - skin rash, hives, redness, or swelling outside of the injection site area
  - dizziness or fainting
  - fast heartbeat or pounding in your chest (tachycardia)
  - sweating
- Nervous system problems. While rare, Multiple Sclerosis has been diagnosed in people who take AVTOZMA. It is not known what effect AVTOZMA may have on some nervous system disorders.

The most common side effects of AVTOZMA include:

- upper respiratory tract infections (common cold, sinus infections)
- headache
- increased blood pressure (hypertension)
- injection site reactions

Tell your healthcare provider about any side effect that bothers you or does not go away. These are not all the possible side effects of AVTOZMA. For more information, ask your healthcare provider or pharmacist.
Call your doctor for medical advice about side effects. You may report side effects to FDA at 1-800-FDA-1088.

General information about the safe and effective use of AVTOZMA.

Medicines are sometimes prescribed for purposes other than those listed in a Medication Guide. Do not give AVTOZMA to other people, even if they have the same symptoms that you have. It may harm them. You can ask your pharmacist or healthcare provider for information about AVTOZMA that is written for health professionals.

What are the ingredients in AVTOZMA?

Active ingredient: tocilizumab-anoh.
Inactive ingredients of Intravenous AVTOZMA: histidine, L-histidine hydrochloride monohydrate, methionine, polysorbate 80, threonine, and water for Injection.
Inactive ingredients of Subcutaneous AVTOZMA: histidine, L-histidine hydrochloride monohydrate, methionine, polysorbate 80, threonine, and water for Injection.

Manufactured by: CELLTRION, Inc., 23, Academy-ro, Yeonsu-gu, Incheon, 22014, Republic of Korea
US License Number 1996

Distributed by: CELLTRION USA, Inc., One Evertrust Plaza, Suite 1207, Jersey City, NJ 07302, USA

Medication Guide has been approved by the U.S. Food and Drug Administration

Issued: 1/2025

Instructions for Use

AVTOZMA® (AV-TOZE'-MAH)
(tocilizumab-anoh)
Injection, For Subcutaneous Use
Single-dose Prefilled Syringe

Read and follow the Instructions for Use that come with your AVTOZMA Preﬁlled Syringe before you start using it and each time you get a reﬁll. There may be new information. Before you use AVTOZMA, make sure your healthcare provider shows you the right way to use it.

Important Information

- Do not remove the prefilled syringe cap until you are ready to inject AVTOZMA.
- Do not try to take apart the prefilled syringe at any time.
- Do not reuse the same syringe.
- Do not shake the prefilled syringe.
- Do not use the prefilled syringe if it has been dropped or damaged.

Storing AVTOZMA

- Store the unused prefilled syringe in the original carton in a refrigerator between 36°F to 46°F (2°C to 8°C). Do not freeze.
- When removed from the refrigerator, AVTOZMA can be stored up to 3 weeks at or below 77°F (25°C). If not used within the 3 weeks, AVTOZMA should be thrown away (discarded).
- Keep the prefilled syringe out of direct sunlight.
- Do not remove the prefilled syringe from its original carton during storage.
- Do not leave the prefilled syringe unattended.
- Keep the prefilled syringe out of the reach of children.

Parts of your Prefilled Syringe (See Figure A).

Figure A

Preparing for the Injection

1. Gather the supplies for the injection.a.Prepare a clean, flat surface, such as a table or countertop, in a well-lit area.b.Take the carton containing the preﬁlled syringe out of the refrigerator.c.Make sure you have the following supplies (see Figure B):-Carton containing AVTOZMA preﬁlled syringe
Not included in the carton:-Cotton ball or gauze-Adhesive bandage-FDA-cleared sharps disposal container-Alcohol swab

Figure B

2. Inspect the carton (see Figure C).a.Look at the carton and make sure you have the correct medicine and dose strength. (AVTOZMA)b.Check the expiration (EXP) date on the carton to make sure the date has not passed.

- Do not use the prefilled syringe if the expiration (EXP) date has passed.
- Do not use the prefilled syringe if the carton looks like it has been opened or damaged if you are opening the carton for the first time and check to make sure that it is properly sealed.

Figure C

3. Inspect the Prefilled Syringe.a.Open the carton and remove 1 single-dose prefilled syringe from the carton. Return any remaining AVTOZMA prefilled syringes in the carton to the refrigerator.b.Check the expiration (EXP) date on the AVTOZMA prefilled syringe (see Figure D).

- Do not use the prefilled syringe if the expiration (EXP) date has passed. If the expiration (EXP) date has passed, safely throw away (dispose of) the prefilled syringe in your FDA-cleared sharps disposal container and get a new one.

c.Check the prefilled syringe to make sure it is not damaged and shows no sign of leakage.

- Do not use the prefilled syringe if it has been dropped, damaged, or has leaked.

Figure D

4. Wait 30 minutes.a.Leave the prefilled syringe outside of the carton at room temperature between 68°F to 77°F (20°C to 25°C) for 30 minutes to allow it to warm up (see Figure E).

- Do not warm the prefilled syringe using heat sources such as hot water or a microwave.
- Do not leave the prefilled syringe in the direct sunlight.
- Do not remove the cap while allowing your prefilled syringe to reach room temperature.
- If the prefilled syringe does not reach room temperature, this could cause discomfort and make it hard to push the plunger.

Figure E

5. Inspect the medicine.a.Hold your AVTOZMA with the cap pointing down.b.Look at the medicine and conﬁrm that the liquid is clear, to slightly pearly and colorless to yellow and does not contain any particles or ﬂakes (see Figure F).

- Do not use the prefilled syringe if the liquid is discolored, cloudy, or has particles or ﬂakes in it. Safely dispose of the prefilled syringe in a FDA-cleared sharps disposal container and use a new one.
- Air bubbles are normal.

Figure F

6. Wash your hands.a.Wash your hands with soap and water and dry them thoroughly (see Figure G).

Figure G

7. Choose an injection site (see Figure H).a.You may inject into-The front of the thighs-The stomach (abdomen), except for the 2 inches (5 cm) around the belly button.-The outer area of the upper arm (only if you are a caregiver).

- Do not inject into the upper arm by yourself.
- Choose a different injection site for each new injection at least 1 inch (2.5 cm) from the last area you injected.
- Do not inject into moles, scars, bruises, or areas where the skin is tender, red, hard or not intact.

Figure H

8. Clean the injection site.a.Wipe the injection site with an alcohol swab and let it air dry for about 10 seconds (see Figure I). This will reduce the chance of getting an infection.

- Do not touch the injection site again before giving the injection.
- Do not fan or blow on the clean area.

Figure I

Giving the Injection

9. Remove the cap.a.Hold the prefilled syringe by the syringe body using 1 hand.
Gently pull the cap straight off with the other hand (see Figure J).
Note: If you cannot remove the cap, you should ask a caregiver for help or contact your healthcare provider.

- Do not hold the plunger while removing the cap.
- You may see a drop of liquid at the tip of the needle. This is normal.
- If the preﬁlled syringe is not used within 5 minutes of needle cap removal, the preﬁlled syringe should be thrown away (disposed of) in the puncture resistant container or sharps container and a new preﬁlled syringe should be used.

b.Throw away (dispose of) the cap right away in your FDA-cleared sharps disposal container (see step 14 and Throw away (dispose of) preﬁlled syringe and Figure N)

- Do not re-cap the preﬁlled syringe.
- Do not touch the needle shield at the tip of the preﬁlled syringe to avoid accidental needle stick injury.

Figure J

10. Insert the preﬁlled syringe into the injection site.a.Gently pinch a fold of skin at the injection site with 1 hand.
Note: Pinching the skin is important to make sure that you inject under the skin (into fatty tissue) but not any deeper (into muscle).b.With a quick and "dart-like" motion, insert the Needle completely into the fold of skin at a 45 to 90-degree angle (see Figure K).
Note: It is important to use the correct angle to make sure the medicine is delivered under the skin (into fatty tissue), or the injection could be painful, and the medicine may not work.

- Do not touch the plunger while inserting the needle into the skin.
- Do not pull back on the plunger rod at any time.

Figure K

11. Give the injection.a.After the needle is inserted, release the pinch.b.Slowly push the plunger all the way down until the full dose of medicine gets injected, and the syringe is empty (see Figure L).

- Do not change the position of the prefilled syringe after the injection has started.
- If the plunger is not fully pressed, the needle guard will not extend to cover the needle when it is removed.
- If the needle is not covered, proceed carefully to dispose of the syringe (see step 14. Throw away (dispose of) prefilled syringe.

Figure L

12. Remove the prefilled syringe from the injection site.a.After the preﬁlled syringe is empty, remove the needle from the injection site and release the plunger until the entire needle is covered by the guard (see Figure M).

- Some bleeding may occur (see step 13. Care for the injection site).
- In case of skin contact with medicine, wash the area that touched the medicine with water.
- Do not reuse the preﬁlled syringe.

Figure M

After the Injection

13. Care for the injection site.a.If a little bleeding occurs, treat the injection site by gently pressing, not rubbing, a cotton ball or gauze to the site and apply an adhesive bandage if needed.

- Do not rub the injection site.

14. Throw away (dispose of) the preﬁlled syringe.a.Put the used prefilled syringe and other supplies in your FDA-cleared sharps disposal container right away after use (see Figure N).
Note: If your injection is given by another person, this person must also be careful when removing the prefilled syringe and disposing of it to prevent accidental needle stick injury and passing infection.

- Do not re-use the prefilled syringe.
- Do not put the cap back onto the prefilled syringe.
- Do not throw away (dispose of) your used sharps disposal container in your household trash.
- Do not recycle your used sharps disposal container.
- Keep the AVTOZMA prefilled syringe and disposal container out of the reach of children.

Figure N

If you do not have an FDA-cleared sharps disposal container, you may use a household container that is:-made of a heavy-duty plastic-can be closed with a tight-fitting, puncture-resistant lid, without sharps being able to come out-upright stable during use-leak-resistant-properly labeled to warn of hazardous waste inside the container

When your sharps disposal container is almost full, you will need to follow your community guidelines for the right way to dispose of your sharps disposal container. There may be state or local laws about how you should dispose of used prefilled syringes. For more information about the safe sharps disposal, and for specific information about sharps disposal in the state that you live in, go to the FDA's website at: http://www.fda.gov/safesharpsdisposal.

15. Record your injection.a.Write the date, time, and speciﬁc part of your body where you injected yourself.

This Instructions for Use has been approved by the U.S. Food and Drug Administration.
Issued: 1/2025

Manufactured by: CELLTRION, Inc., 23, Academy-ro, Yeonsu-gu, Incheon, 22014, Republic of Korea
US License Number 1996

Distributed by: CELLTRION USA, Inc., One Evertrust Plaza Suite 1207, Jersey City, NJ 07302

Instructions for Use

VTOZMA® (AV-TOZE'-MAH)
(tocilizumab-anoh)
Injection, For Subcutaneous Use
Single-dose Prefilled Autoinjector

Read and follow the Instructions for Use that come with your AVTOZMA prefilled autoinjector before you start using it and each time you get a reﬁll. There may be new information. Before you use AVTOZMA, make sure your healthcare provider shows you the right way to use it.

Important Information

- Do not remove the prefilled autoinjector cap until you are ready to inject AVTOZMA.
- Do not try to take apart the prefilled autoinjector at any time.
- Do not reuse the same prefilled autoinjector.
- Do not inject through clothing.
- Do not use the prefilled autoinjector if it has been dropped or damaged.

Storing AVTOZMA

- Store the unused prefilled autoinjector in the original carton in a refrigerator between 36°F to 46ºF (2°C to 8ºC). Do not freeze.
- When removed from the refrigerator, AVTOZMA can be stored up to 3 weeks at or below 77°F (25°C). If not used within the 3 weeks, AVTOZMA should be thrown away (discarded).
- Keep the prefilled autoinejctor out of direct sunlight.
- Do not remove the prefilled autoinjector from its original carton during storage.
- Do not leave the prefilled autoinjector unattended.
- Keep the prefilled autoinjector out of the reach of children.

Parts of your AVTOZMA prefilled autoinjector (See Figure A).

Figure A

Preparing for the Injection

1. Gather the supplies for the injection.a.Prepare a clean, flat surface, such as a table or countertop, in a well-lit area.b.Take the carton containing the prefilled autoinjector out of the refrigerator.c.Make sure you have the following supplies (see Figure B):-Carton containing AVTOZMA preﬁlled autoinjector
Not included in the carton:-Cotton ball or gauze-Adhesive bandage-FDA-cleared Sharps disposal container-Alcohol swab

Figure B

2. Inspect the carton (see Figure C).a.Look at the carton and make sure you have the correct medicine and dose strength. (AVTOZMA)b.Check the expiration (EXP) date on the carton to make sure the date has not passed.

- Do not use the prefilled autoinjector if the expiration (EXP) date has passed.
- If you are opening the carton for the first time, check to make sure that it is properly sealed.
- Do not use the prefilled autoinjector if the carton looks like it has been opened or damaged.

Figure C

3. Inspect the Prefilled autoinjector.a.Open the carton and remove one single-dose prefilled autoinjector from the carton. Return any remaining AVTOZMA prefilled autoinjectors in the box to the refrigerator.b.Check the expiration (EXP) date on the AVTOZMA prefilled autoinjector (see Figure D).

- Do not use the prefilled autoinjector if the expiration (EXP) date has passed. If the expiration (EXP) date has passed, safely throw away (dispose of) the prefilled autoinjector in your sharps disposal container and get a new one.

c.Check the prefilled autoinjector to make sure it is not damaged and shows no sign of leakage.

- Do not use the prefilled autoinjector if it has been dropped, damaged, or has leaked.

Note: A small gap between the orange cap and injector body is normal.

Figure D

4. Wait 45 minutes.a.Leave the prefilled autoinjector outside of the carton at room temperature between 68°F to 77°F (20°C to 25°C) for 45 minutes to allow it to warm up (see Figure E).

- Do not warm the prefilled autoinjector using heat sources such as hot water or a microwave.
- Do not leave the prefilled autoinjector in the direct sunlight.
- Do not remove the cap while allowing your prefilled autoinjector to reach room temperature.
- If the prefilled autoinjector does not reach room temperature, this could cause discomfort.

Figure E

5. Inspect the medicine.a.Hold your AVTOZMA with the cap pointing down.b.Look at the medicine and conﬁrm that the liquid is clear, to slightly pearly and colorless to yellow and does not contain any particles or ﬂakes (see Figure F).

- Do not use the prefilled autoinjector if the liquid is discolored, cloudy, or has particles or ﬂakes in it. Safely dispose of the prefilled autoinjector in a FDA-cleared sharps disposal container and use a new one.
- Air bubbles are normal.

Figure F

6. Wash your hands.a.Wash your hands with soap and water and dry them thoroughly (see Figure G).

Figure G

7. Choose an injection site (see Figure H).a.You may inject into-The front of the thighs-The stomach (abdomen), except for the 2 inches (5 cm) around the belly button.-The outer area of the upper arm (only if you are a caregiver).

- Do not inject into the upper arm by yourself.
- Choose a different injection site for each new injection at least 1 inch (2.5 cm) from the last area you injected.
- Do not inject into moles, scars, bruises, or areas where the skin is tender, red, hard or not intact.

Figure H

8. Clean the injection site.b.Wipe the injection site with an alcohol swab and let it air dry (see Figure I). This will reduce the chance of getting an infection.

- Do not touch the injection site again before giving the injection.
- Do not fan or blow on the clean area.

Figure I

Giving the Injection

9. Remove the cap.a.Hold the prefilled autoinjector by the injector body with the cap on top using 1 hand.
Gently pull the cap straight off with the other hand (see Figure J).
Note: If you cannot remove the cap, you should ask a caregiver for help or contact your healthcare provider.b.Throw away (dispose of) the cap right away in your FDA-cleared sharps disposal container (see step 14 and Figure O)

- Do not re-cap the prefilled autoinjector.
- Do not touch the needle shield at the tip of the prefilled autoinjector to avoid accidental needle stick injury.
- After you remove the cap, the prefilled autoinjector is ready for use. If the prefilled autoinjector is not used within 3 minutes of cap removal, throw away the prefilled autoinjector in a FDA-cleared sharps disposal container and use a new prefilled autoinjector.

Figure J

10. Place the prefilled autoinjector on the injection site.a.Hold the prefilled autoinjector comfortably in 1 hand so that you can see the window (see Figure K).b.Without pinching or stretching the skin, place the prefilled autoinjector against the skin at a 90-degree angle (see Figure L).
Note: It is important to use the correct angle to make sure the medicine is delivered under the skin (into fatty tissue), or the injection could be painful, and the medicine may not work

- Do not inject into muscle or a blood vessel.

Figure K

Figure L

11. Give the injection.a.Firmly press the prefilled autoinjector into the skin to begin the injection.b.When the injection starts you will hear the 1st "click" and the orange indicator will begin to ﬁll the window (see Figure M).c.Keep holding the prefilled autoinjector ﬁrmly against the skin and listen for the 2nd "click".d.After you hear the 2nd "click", continue to hold the prefilled autoinjector ﬁrmly against the skin and count slowly to 5 to make sure you inject the full dose (see Figure M).e.Watch the orange indicator until it stops moving and has reached the end of the window to be sure the full dose of medicine is injected.

Figure M

12. Remove the prefilled autoinjector from the injection site.a.When the orange indicator has stopped moving, lift the prefilled autoinjector straight off of the injection site at a 90-degree angle to remove the needle from the skin.

- The needle cover will automatically move out and lock into place covering the needle (see Figure N).

Note: If the window has not turned completely orange or if the medicine is still injecting, this means you have not received a full dose. Carefully place the prefilled autoinjector into the FDA-cleared sharps disposal container and call your healthcare provider immediately.

- Do not touch the needle cover of the prefilled autoinjector.
- Do not try to re-use the prefilled autoinjector.
- Do not repeat the injection with another prefilled autoinjector.

Figure N

After the Injection

13. Care for the injection site.a.If a little bleeding occurs, treat the injection site by gently pressing, not rubbing, a cotton ball or gauze to the site and apply an adhesive bandage if needed.

- Do not rub the injection site

14. Dispose of AVTOZMA.a.Put the used prefilled autoinjector and other supplies in your FDA-cleared sharps disposal container right away after use (see Figure O).
Note: If your injection is given by another person, this person must also be careful when removing the prefilled autoinjector and disposing of it to prevent accidental needle stick injury and passing infection.

- Do not re-use the prefilled autoinjector.
- Do not put the cap back onto the prefilled autoinjector.
- Do not dispose of your used sharps disposal container in your household trash.
- Do not recycle your used sharps disposal container.
- Keep the AVTOZMA prefilled autoinjector and disposal container out of the reach of children.

Figure O

If you do not have an FDA-cleared sharps disposal container, you may use a household container that is:-made of a heavy-duty plastic-can be closed with a tight-fitting, puncture-resistant lid, without sharps being able to come out-upright stable during use-leak-resistant-properly labeled to warn of hazardous waste inside the container

When your sharps disposal container is almost full, you will need to follow your community guidelines for the right way to dispose of your sharps disposal container. There may be state or local laws about how you should dispose of used autoinjectors. For more information about the safe sharps disposal, and for specific information about sharps disposal in the state that you live in, go to the FDA's website at: http://www.fda.gov/safesharpsdisposal.

15. Record your injection.a.Write the date, time, and speciﬁc part of your body where you injected yourself.

This Instructions for Use has been approved by the U.S. Food and Drug Administration.
Issued: 1/2025

Manufactured by: CELLTRION, Inc., 23, Academy-ro, Yeonsu-gu, Incheon, 22014, Republic of Korea
US License Number 1996

Distributed by: CELLTRION USA, Inc., One Evertrust Plaza Suite 1207, Jersey City, NJ 07302

PRINCIPAL DISPLAY PANEL - 80 mg/4 mL Vial Carton

NDC 72606-042-02
Rx only

Avtozma®
(tocilizumab-anoh)

Injection
80 mg/4 mL
(20 mg/mL)

For Intravenous Infusion After Dilution.
Single-Dose Vial.
Discard Unused Portion.

4 vials

CELLTRION USA
CELLTRION

PRINCIPAL DISPLAY PANEL - 200 mg/10 mL Vial Carton

NDC 72606-043-02
Rx only

Avtozma®
(tocilizumab-anoh)

Injection
200 mg/10 mL
(20 mg/mL)

For Intravenous Infusion After Dilution.
Single-Dose Vial.
Discard Unused Portion.

4 vials

CELLTRION USA
CELLTRION

PRINCIPAL DISPLAY PANEL - 400 mg/20 mL Vial Carton

NDC 72606-044-02
Rx only

Avtozma®
(tocilizumab-anoh)

Injection
400 mg/20 mL
(20 mg/mL)

For Intravenous Infusion After Dilution.
Single-Dose Vial.
Discard Unused Portion.

4 vials

CELLTRION USA
CELLTRION

PRINCIPAL DISPLAY PANEL - 162 mg/0.9 mL Prefilled Syringe Carton - NDC 72606-045-01

Avtozma®
(tocilizumab-anoh)
Injection

162 mg/0.9 mL

FOR SUBCUTANEOUS USE ONLY
ATTENTION: Dispense the enclosed
Medication Guide to each patient

NDC 72606-045-01

Rx only

Each carton contains 1 single-dose Prefilled syringe with safety guard,
1 Medication Guide,
1 Prescribing Information and 1 Instructions for Use

1
single-dose
Prefilled syringe with safety guard

CELLTRION USA
CELLTRION

PRINCIPAL DISPLAY PANEL - 162 mg/0.9 mL Prefilled Syringe Carton - NDC 72606-045-02

Avtozma®
(tocilizumab-anoh)
Injection

162 mg/0.9 mL

FOR SUBCUTANEOUS USE ONLY
ATTENTION: Dispense the enclosed
Medication Guide to each patient

NDC 72606-045-02

Rx only

Each carton contains 4 single-dose Prefilled syringes with safety guard,
1 Medication Guide,
1 Prescribing Information and 1 Instructions for Use

4
single-dose
Prefilled syringe with safety guard

CELLTRION USA
CELLTRION

PRINCIPAL DISPLAY PANEL - 4 Prefilled Syringe Carton - NDC 72606-045-03

Avtozma®
(tocilizumab-anoh)
Injection

162 mg/0.9 mL

FOR SUBCUTANEOUS USE ONLY
ATTENTION: Dispense the enclosed
Medication Guide to each patient

NDC 72606-045-03

Rx only

Each carton contains 4 single-dose Prefilled syringes with safety guard,
1 Medication Guide,
1 Prescribing Information and 1 Instructions for Use

4
single-dose
Prefilled syringe with safety guard

CELLTRION USA
CELLTRION

PRINCIPAL DISPLAY PANEL - 12 Prefilled Syringe Carton - NDC 72606-045-03

Avtozma®
(tocilizumab-anoh)
Injection

162 mg/0.9 mL

FOR SUBCUTANEOUS USE ONLY
ATTENTION: Dispense the enclosed
Medication Guide to each patient

Multipack contains:

- Three cartons
- Each carton contains four 0.9-mL single-dose prefilled syringes with safety guard
- 1 Medication Guide
- 1 Prescribing Information
- 1 Instructions for Use

NDC 72606-045-03

Rx only

Multipack:
12 (3 packs of 4) prefilled syringes with safety guard

12
single-dose
Prefilled syringes with safety guard

CELLTRION USA
CELLTRION

PRINCIPAL DISPLAY PANEL - 162 mg/0.9 mL Autoinjector Carton - NDC 72606-045-04

Avtozma®
(tocilizumab-anoh)
Injection

162 mg/0.9 mL

FOR SUBCUTANEOUS USE ONLY
ATTENTION: Dispense the enclosed Medication Guide to each patient

NDC 72606-045-04

Rx only

Each carton contains 1 single-dose Autoinjector,
1 Medication Guide,
1 Prescribing Information and 1 Instructions for Use

1
single-dose
Autoinjector

CELLTRION USA
CELLTRION

PRINCIPAL DISPLAY PANEL - 162 mg/0.9 mL Autoinjectors Carton - NDC 72606-045-05

Avtozma®
(tocilizumab-anoh)
Injection

162 mg/0.9 mL

FOR SUBCUTANEOUS USE ONLY
ATTENTION: Dispense the enclosed
Medication Guide to each patient

NDC 72606-045-05

Rx only

Each carton contains 4 single-dose Autoinjectors,
1 Medication Guide,
1 Prescribing Information and 1 Instructions for Use

4
single-dose
Autoinjectors

CELLTRION USA
CELLTRION

PRINCIPAL DISPLAY PANEL - 4 Autoinjectors Carton - NDC 72606-045-06

Avtozma®
(tocilizumab-anoh)
Injection

162 mg/0.9 mL

FOR SUBCUTANEOUS USE ONLY
ATTENTION: Dispense the enclosed
Medication Guide to each patient

NDC 72606-045-06

Rx only

Each carton contains 4 single-dose Autoinjectors,
1 Medication Guide,
1 Prescribing Information and 1 Instructions for Use

4
single-dose
Autoinjectors

CELLTRION USA
CELLTRION

PRINCIPAL DISPLAY PANEL - 12 Autoinjectors Carton - NDC 72606-045-06

Avtozma®
(tocilizumab-anoh)
Injection

162 mg/0.9 mL

FOR SUBCUTANEOUS USE ONLY
ATTENTION: Dispense the enclosed
Medication Guide to each patient

Multipack contains:

- Three cartons
- Each carton contains four 0.9-mL single-dose autoinjectors
- 1 Medication Guide
- 1 Prescribing Information
- 1 Instructions for Use

NDC 72606-045-06

Rx only

Multipack:
12 (3 packs of 4) autoinjectors

12
single-dose
Autoinjectors

CELLTRION USA
CELLTRION